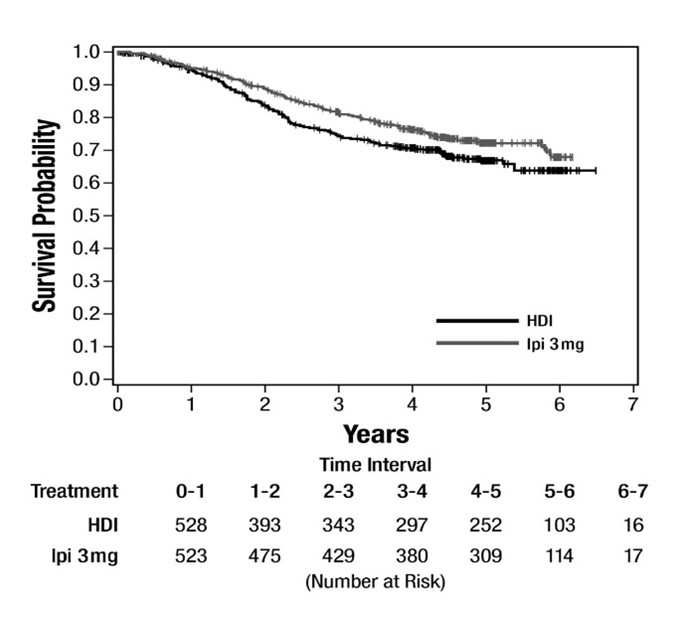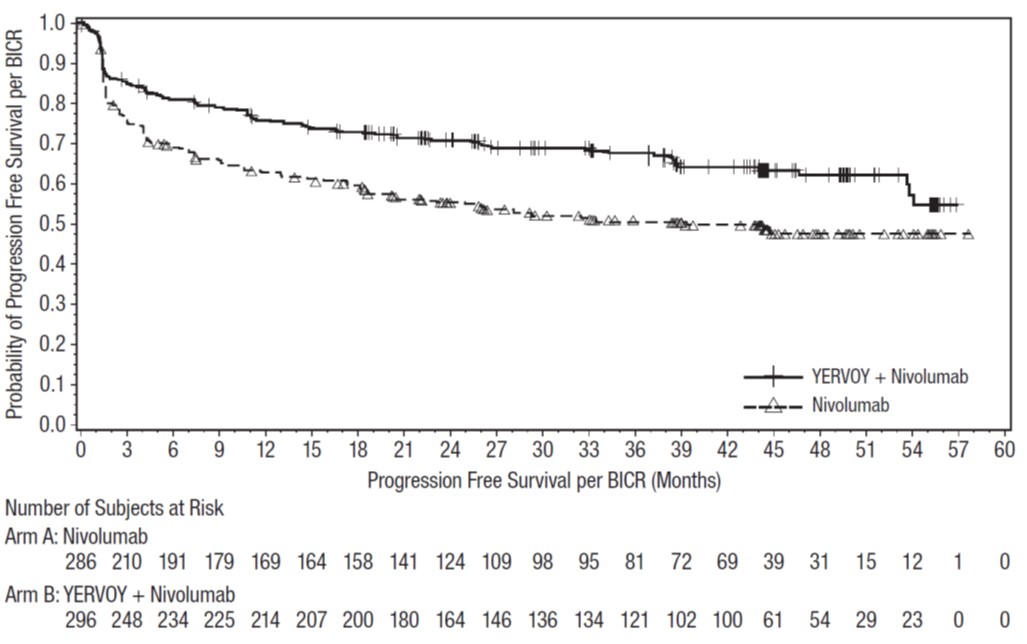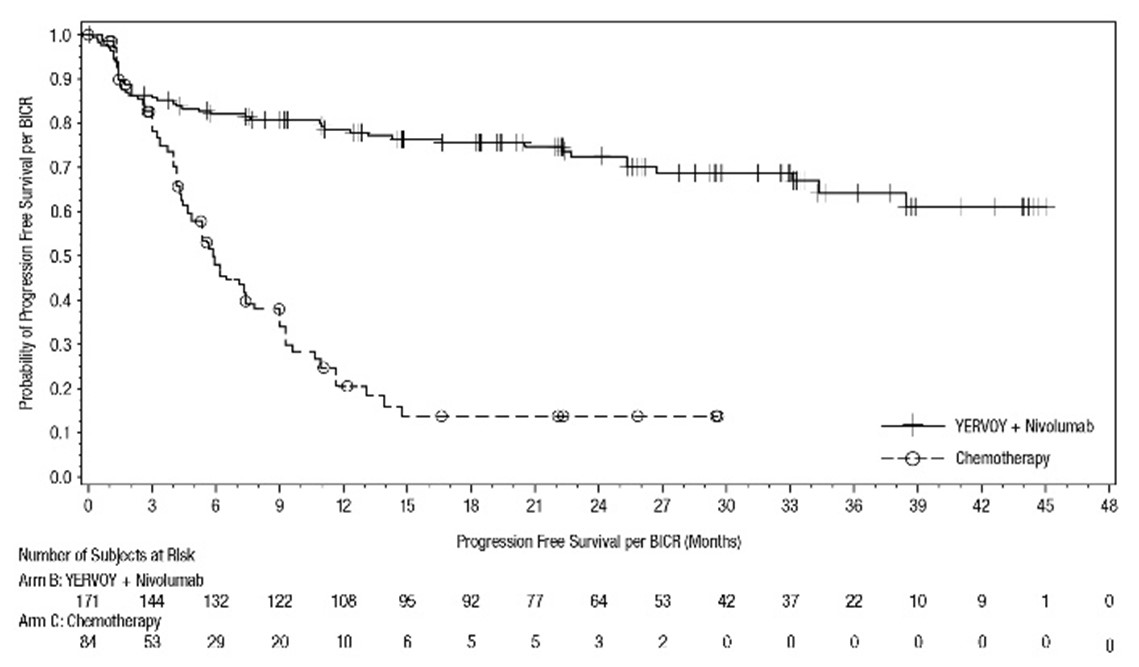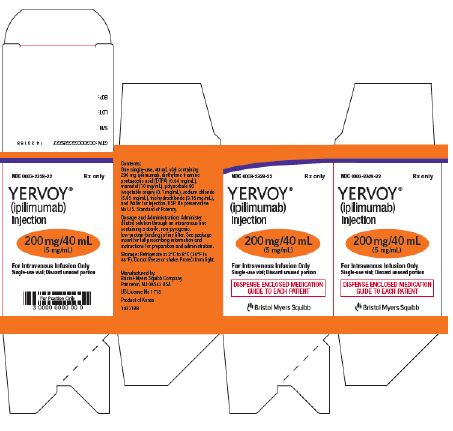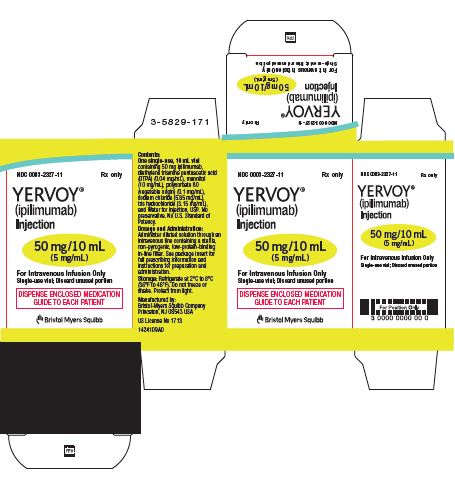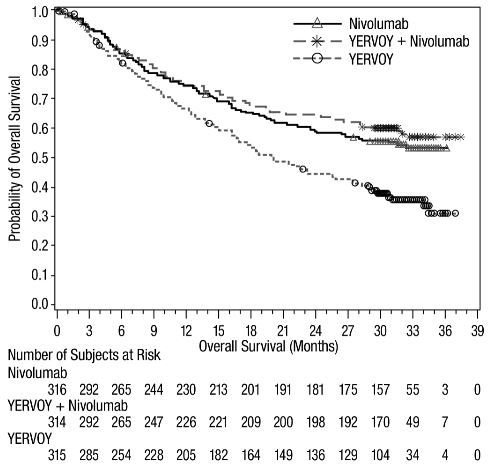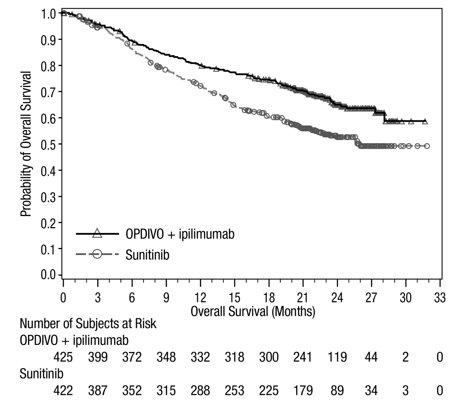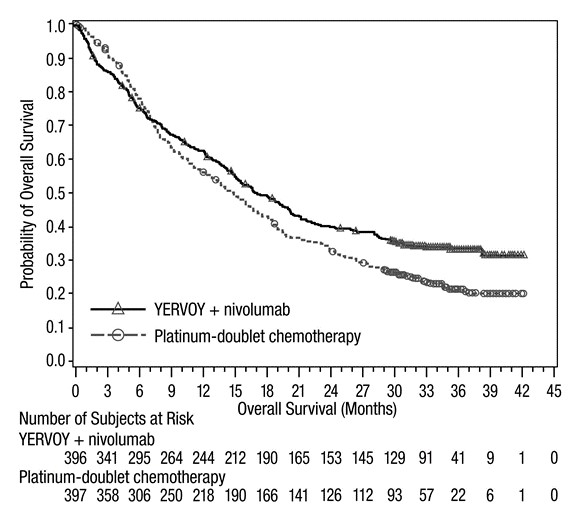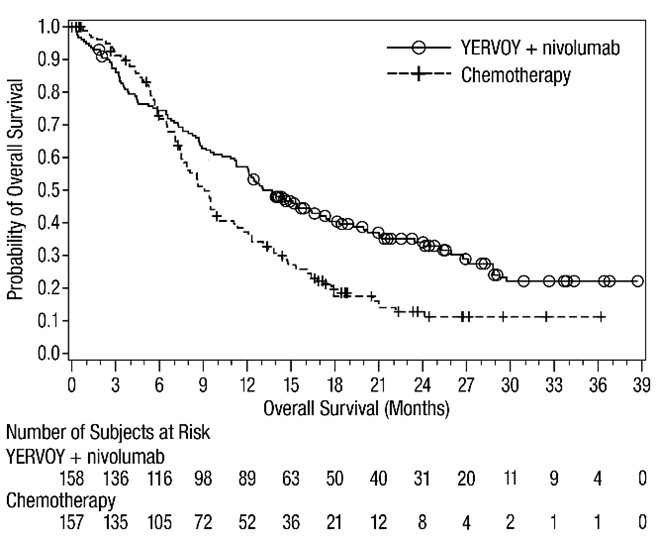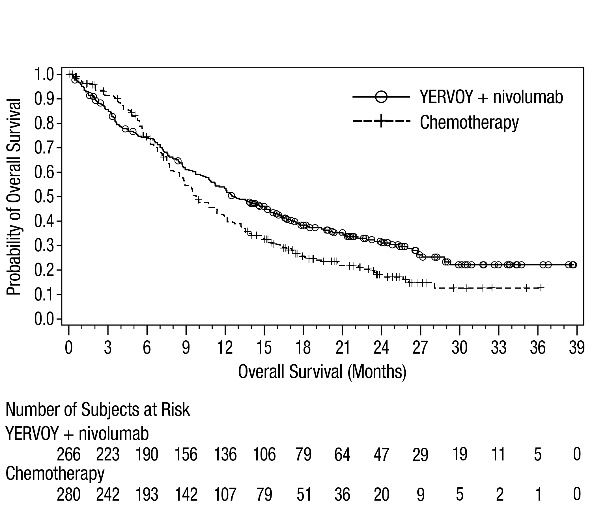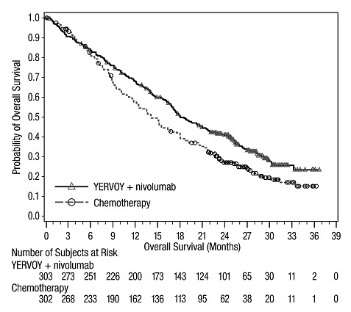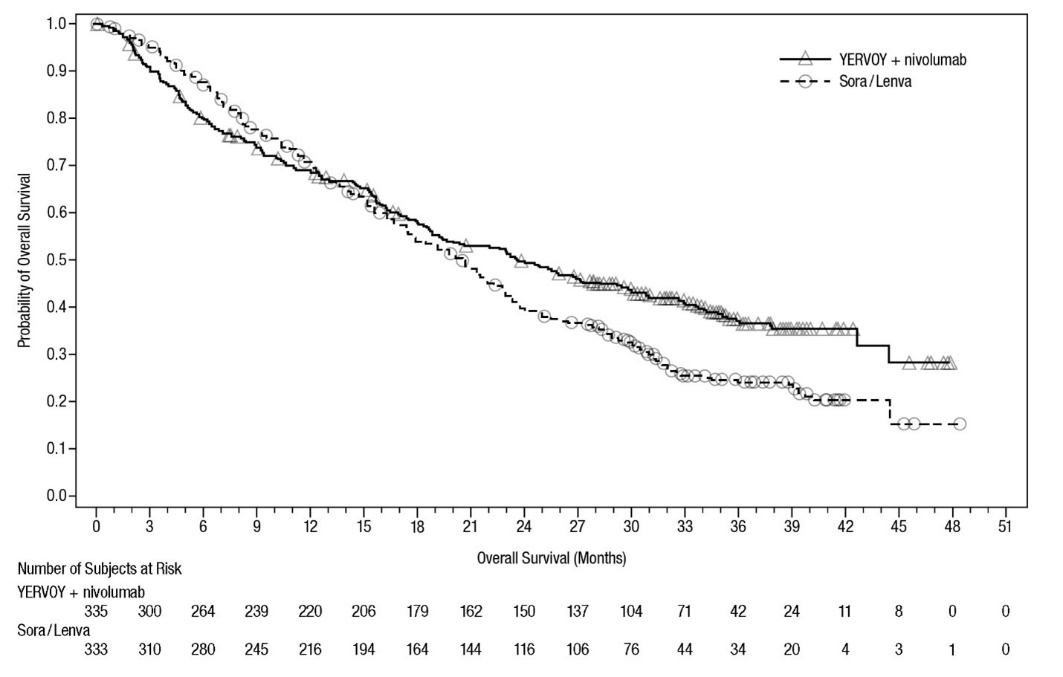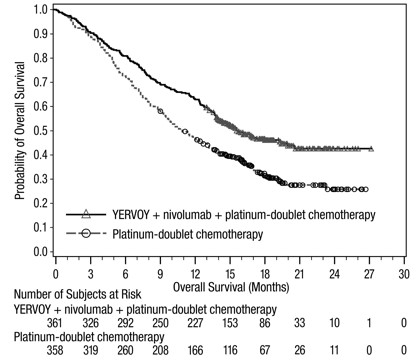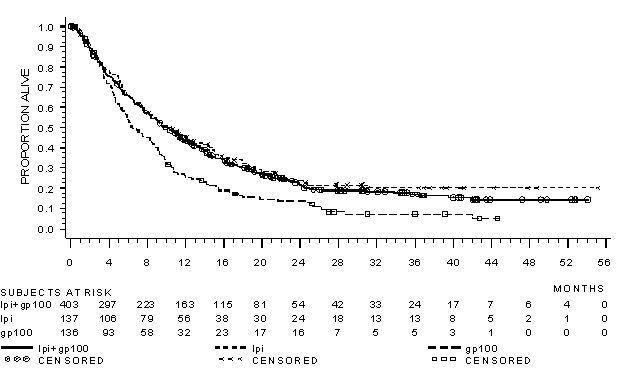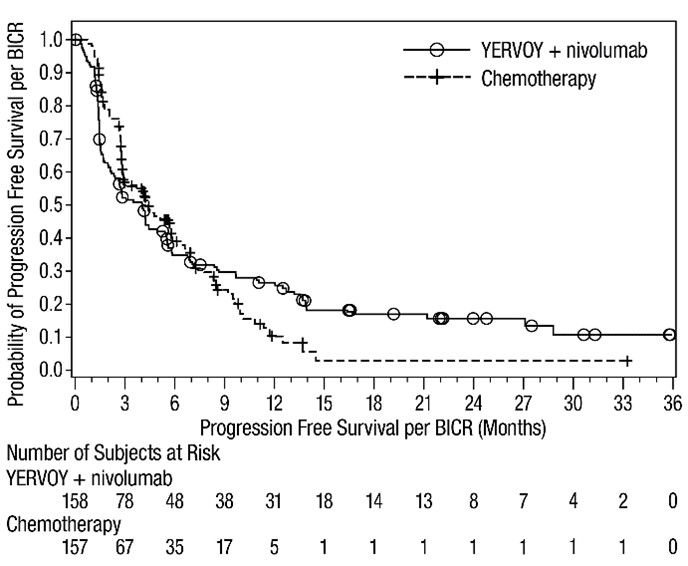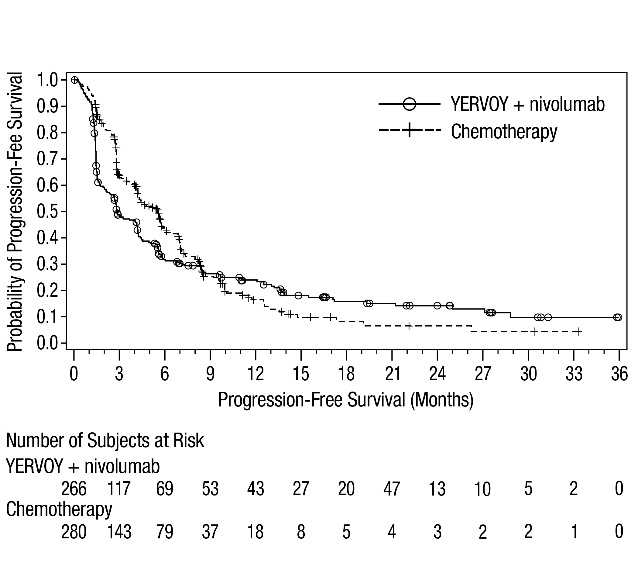 DRUG LABEL: YERVOY
NDC: 0003-2327 | Form: INJECTION
Manufacturer: E.R. Squibb & Sons, L.L.C.
Category: prescription | Type: HUMAN PRESCRIPTION DRUG LABEL
Date: 20250528

ACTIVE INGREDIENTS: IPILIMUMAB 5 mg/1 mL
INACTIVE INGREDIENTS: TROMETHAMINE HYDROCHLORIDE 3.15 mg/1 mL; SODIUM CHLORIDE 5.85 mg/1 mL; MANNITOL 10 mg/1 mL; PENTETIC ACID 0.04 mg/1 mL; POLYSORBATE 80 0.1 mg/1 mL; WATER

HIGHLIGHTS OF PRESCRIBING INFORMATION

These highlights do not include all the information needed to use YERVOY safely and effectively. See full prescribing information for YERVOY.
YERVOY® (ipilimumab) injection, for intravenous use
Initial U.S. Approval: 2011

RECENT MAJOR CHANGES

Indications and Usage (1) | 5/2025
Dosage and Administration (2) | 5/2025

1 INDICATIONS AND USAGE

YERVOY is a human cytotoxic T-lymphocyte antigen 4 (CTLA-4)-blocking antibody indicated for:

Melanoma

- Treatment of unresectable or metastatic melanoma in adults and pediatric patients 12 years and older as a single agent or in combination with nivolumab. (1.1)
- Adjuvant treatment of adult patients with cutaneous melanoma with pathologic involvement of regional lymph nodes of more than 1 mm who have undergone complete resection, including total lymphadenectomy. (1.2)

Renal Cell Carcinoma (RCC)

- Treatment of adult patients with intermediate or poor risk advanced renal cell carcinoma, as first-line treatment in combination with nivolumab. (1.3)

Colorectal Cancer

- Treatment of adults and pediatric patients 12 years and older with unresectable or metastatic microsatellite instability-high (MSI-H) or mismatch repair deficient (dMMR) colorectal cancer (CRC) in combination with nivolumab. (1.4)

Hepatocellular Carcinoma

- adult patients with unresectable or metastatic hepatocellular carcinoma (HCC) as first-line treatment in combination with nivolumab. (1.5)
- in combination with nivolumab in adult patients with unresectable or metastatic HCC who have been previously treated with sorafenib. (1.5)

Non-Small Cell Lung Cancer (NSCLC)

- Treatment of adult patients with metastatic non-small cell lung cancer expressing PD-L1 (≥1%) as determined by an FDA-approved test, with no EGFR or ALK genomic tumor aberrations, as first-line treatment in combination with nivolumab. (1.6)
- Treatment of adult patients with metastatic or recurrent non-small cell lung cancer with no EGFR or ALK genomic tumor aberrations as first-line treatment, in combination with nivolumab and 2 cycles of platinum-doublet chemotherapy. (1.6)

Malignant Pleural Mesothelioma

- Treatment of adult patients with unresectable malignant pleural mesothelioma, as first-line treatment in combination with nivolumab. (1.7)

Esophageal Cancer

- Treatment of adult patients with unresectable advanced or metastatic esophageal squamous cell carcinoma, as first line treatment in combination with nivolumab whose tumors express PD-L1 (≥1). (1.8)

2 DOSAGE AND ADMINISTRATION

- Administer by intravenous infusion after dilution based upon recommended infusion rate for each indication. (2)
- Unresectable or Metastatic Melanoma:
  ∘ YERVOY 3 mg/kg every 3 weeks for a maximum of 4 doses. (2.2)
  ∘ YERVOY 3 mg/kg immediately following nivolumab 1 mg/kg on the same day, every 3 weeks for 4 doses. After completing 4 doses of the combination, administer nivolumab as a single agent as recommended in the Full Prescribing Information for nivolumab. (2.2)
- Adjuvant Treatment of Melanoma: YERVOY 3 mg/kg every 3 weeks for 4 doses, followed by 3 mg/kg every 12 weeks for up to 4 additional doses. (2.2)
- Advanced Renal Cell Carcinoma: YERVOY 1 mg/kg immediately following nivolumab 3 mg/kg on the same day, every 3 weeks for 4 doses. After completing 4 doses of the combination, administer nivolumab as a single agent as recommended in Full Prescribing Information for nivolumab. (2.2)
- Treatment of microsatellite instability-high (MSI-H) or mismatch repair deficient (dMMR) colorectal cancer in combination with nivolumab:
  ∘ Adult and pediatric patients weighing 40 kg or greater: YERVOY 1 mg/kg immediately following nivolumab 240 mg on the same day every 3 weeks for a maximum of 4 doses. After completing the combination, administer nivolumab as a single agent as recommended in Full Prescribing Information for nivolumab. (2.2)
  ∘ Pediatric patients weighing less than 40 kg: YERVOY 1 mg/kg immediately following nivolumab 3 mg/kg on the same day every 3 weeks for a maximum of 4 doses. After completing the combination, administer nivolumab as a single agent as recommended in Full Prescribing Information for nivolumab. (2.2)
- Hepatocellular Carcinoma: YERVOY 3 mg/kg intravenously over 30 minutes immediately following nivolumab 1 mg/kg intravenously over 30 minutes on the same day, every 3 weeks for up to 4 doses. After completing up to 4 doses of the combination, administer nivolumab as a single agent as recommended in Full Prescribing Information for nivolumab. (2.2)
- Metastatic non-small cell lung cancer:
  ∘ YERVOY 1 mg/kg every 6 weeks with nivolumab 360 mg every 3 weeks. (2.2)
  ∘ YERVOY 1 mg/kg every 6 weeks with nivolumab 360 mg every 3 weeks and 2 cycles of platinum-doublet chemotherapy. (2.2)
- Malignant pleural mesothelioma: YERVOY 1 mg/kg every 6 weeks with nivolumab 360 mg every 3 weeks. (2.2)
- Esophageal squamous cell carcinoma: YERVOY 1 mg/kg every 6 weeks with nivolumab 3 mg/kg every 2 weeks or 360 mg every 3 weeks. (2.2)
- See full Prescribing Information for preparation and administration instructions and dosage modifications for adverse reactions.

3 DOSAGE FORMS AND STRENGTHS

- Injection: 50 mg/10 mL (5 mg/mL) and 200 mg/40 mL (5 mg/mL) in a single-dose vial. (3)

4 CONTRAINDICATIONS

- None. (4)

5 WARNINGS AND PRECAUTIONS

- Severe and Fatal Immune-Mediated Adverse Reactions: Immune-mediated adverse reactions (IMAR) can occur in any organ system or tissue, including the following: immune-mediated colitis, immune-mediated hepatitis, immune-mediated dermatologic adverse reactions, immune-mediated endocrinopathies, immune-mediated pneumonitis, and immune-mediated nephritis with renal dysfunction, and can occur at any time during treatment or after discontinuation. Monitor for symptoms and signs that may be clinical manifestations of IMAR. Evaluate clinical chemistries including liver enzymes, creatinine, adrenocorticotropic hormone level and thyroid function including at baseline and before each dose. In general, withhold YERVOY for severe (grade 3) and permanently discontinue for life-threatening (grade 4) immune-mediated adverse reactions. See Full Prescribing Information for additional dosage modifications. (2.3, 5.1)
- Infusion-Related Reactions: Discontinue for severe and life-threatening infusion-related reactions. Interrupt or slow the rate of infusion in patients with mild or moderate infusion-related reactions. (2.3, 5.2)
- Complications of allogeneic HSCT: Fatal and other serious complications can occur in patients who receive allogeneic HSCT before or after being treated with YERVOY. (5.3)
- Embryo-Fetal Toxicity: Can cause fetal harm. Advise of potential risk to a fetus and use of effective contraception. (5.4, 8.1, 8.3)

6 ADVERSE REACTIONS

Most common adverse reactions (≥20%) with YERVOY as a single agent are fatigue, diarrhea, pruritus, rash, nausea, and headache. (6.1)

Most common adverse reactions (≥20%) with YERVOY in combination with nivolumab are fatigue, diarrhea, rash, pruritus, nausea, musculoskeletal pain, pyrexia, cough, decreased appetite, vomiting, abdominal pain, dyspnea, upper respiratory tract infection, arthralgia, headache, hypothyroidism, constipation, decreased weight, and dizziness. (6.1)

Most common adverse reactions (≥20%) with YERVOY in combination with nivolumab and platinum-doublet chemotherapy are fatigue, musculoskeletal pain, nausea, diarrhea, rash, decreased appetite, constipation, and pruritus. (6.1)

To report SUSPECTED ADVERSE REACTIONS, contact Bristol-Myers Squibb at 1-800-721-5072 or FDA at 1-800-FDA-1088 or www.fda.gov/medwatch.

8 USE IN SPECIFIC POPULATIONS

- Lactation: Advise not to breastfeed. (8.2)

FULL PRESCRIBING INFORMATION

1 INDICATIONS AND USAGE

1.1 Unresectable or Metastatic Melanoma

YERVOY, as a single agent or in combination with nivolumab, is indicated for the treatment of unresectable or metastatic melanoma in adult and pediatric patients 12 years and older.

1.2 Adjuvant Treatment of Melanoma

YERVOY is indicated for the adjuvant treatment of adult patients with cutaneous melanoma with pathologic involvement of regional lymph nodes of more than 1 mm who have undergone complete resection, including total lymphadenectomy.

1.3 Advanced Renal Cell Carcinoma

YERVOY, in combination with nivolumab, is indicated for the first-line treatment of adult patients with intermediate or poor risk advanced renal cell carcinoma (RCC).

1.4 Microsatellite Instability-High or Mismatch Repair Deficient Metastatic Colorectal Cancer

- YERVOY, in combination with nivolumab, is indicated for the treatment of adult and pediatric patients 12 years and older with unresectable or metastatic microsatellite instability-high (MSI-H) or mismatch repair deficient (dMMR) colorectal cancer (CRC).

1.5 Hepatocellular Carcinoma

- YERVOY, in combination with nivolumab, is indicated for the first-line treatment of adult patients with unresectable or metastatic hepatocellular carcinoma (HCC).
- YERVOY, in combination with nivolumab, is indicated for the treatment of adult patients with unresectable or metastatic HCC who have been previously treated with sorafenib.

1.6 Metastatic Non-Small Cell Lung Cancer

YERVOY, in combination with nivolumab, is indicated for the first-line treatment of adult patients with metastatic non-small cell lung cancer (NSCLC) whose tumors express PD-L1 (≥1%) as determined by an FDA-approved test [see Dosage and Administration (2.1)], with no EGFR or ALK genomic tumor aberrations.

YERVOY, in combination with nivolumab and 2 cycles of platinum-doublet chemotherapy, is indicated for the first-line treatment of adult patients with metastatic or recurrent NSCLC, with no EGFR or ALK genomic tumor aberrations.

1.7 Malignant Pleural Mesothelioma

YERVOY, in combination with nivolumab, is indicated for the first-line treatment of adult patients with unresectable malignant pleural mesothelioma.

1.8 Esophageal Cancer

YERVOY, in combination with nivolumab, is indicated for the first-line treatment of adult patients with unresectable advanced or metastatic esophageal squamous cell carcinoma (ESCC) whose tumors express PD-L1 (≥1) [see Dosage and Administration (2.1)].

2 DOSAGE AND ADMINISTRATION

2.1 Patient Selection

Information on FDA-approved tests for patient selection is available at:

https://www.fda.gov/CompanionDiagnostics

Non-Small Cell Lung Cancer

- Select patients with metastatic NSCLC for treatment with YERVOY in combination with nivolumab based on PD-L1 expression [see Clinical Studies (14.6)].

Esophageal Cancer

- Select patients with unresectable or advanced or metastatic ESCC for treatment with YERVOY in combination with nivolumab based on PD-L1 expression [see Clinical Studies (14.8)].
- An FDA-approved companion diagnostic for the detection of PD-L1 expression in patients with advanced or metastatic ESCC is not available.

2.2 Recommended Dosage

The recommended dosages of YERVOY as a single agent are presented in Table 1.

Administer YERVOY as a 30-minute intravenous infusion [see Preparation and Administration (2.4)].

Table 1: Recommended Dosages for YERVOY as a Single Agent
Indication | Recommended YERVOY Dosage | Duration of Therapy
Unresectable or metastatic melanoma | 3 mg/kg every 3 weeks | Maximum of 4 doses
Adjuvant treatment of melanoma | 3 mg/kg every 3 weeks; followed by 3 mg/kg every 12 weeks | Every 3 weeks up to a maximum of 4 doses; Every 12 weeks for up to 4 additional doses

The recommended dosages of YERVOY in combination with other therapeutic agents are presented in Table 2. Administer YERVOY on the same day as other therapeutic agents.

Refer to the respective Prescribing Information for each therapeutic agent administered in combination with YERVOY for recommended dosage information, as appropriate.

Table 2: Recommended Dosages of YERVOY in Combination with Other Therapeutic Agents*
Indication | Recommended YERVOY Dosage | Duration of Therapy
Unresectable or metastatic melanoma | 3 mg/kg every 3 weeks; with nivolumab 1 mg/kg | In combination with nivolumab for a maximum of 4 doses or until unacceptable toxicity, whichever occurs earlier.; After completing 4 doses of combination therapy, administer nivolumab as a single agent until disease progression or unacceptable toxicity.†
Advanced renal cell carcinoma | 1 mg/kg every 3 weeks; with nivolumab 3 mg/kg | In combination with nivolumab for a maximum of 4 doses.; After completing 4 doses of combination therapy, administer nivolumab as single agent until disease progression or unacceptable toxicity.†
Microsatellite instability-high (MSI‑H) or mismatch repair deficient (dMMR) metastatic colorectal cancer | Adult patients and pediatric patients age 12 years and older and weighing 40 kg or more:; 1 mg/kg every 3 weeks; with nivolumab 240 mg | In combination with nivolumab for a maximum of 4 doses.†; After completing 4 doses of combination therapy, administer nivolumab as single agent until disease progression, unacceptable toxicity, or up to 2 years.†
Microsatellite instability-high (MSI‑H) or mismatch repair deficient (dMMR) metastatic colorectal cancer | Pediatric patients age 12 years and older and weighing less than 40 kg:; 1 mg/kg every 3 weeks with nivolumab 3 mg/kg | In combination with nivolumab for a maximum of 4 doses.†; After completing 4 doses of combination therapy, administer nivolumab as single agent until disease progression, unacceptable toxicity, or up to 2 years.†
Hepatocellular carcinoma | 3 mg/kg every 3 weeks; with nivolumab 1 mg/kg | In combination with nivolumab for a maximum of 4 doses.; After completing a maximum of 4 doses of combination therapy, administer nivolumab as single agent until disease progression or unacceptable toxicity.†
Metastatic non-small cell lung cancer expressing PD‑L1 | 1 mg/kg every 6 weeks; with nivolumab 360 mg every 3 weeks | In combination with nivolumab until disease progression, unacceptable toxicity, or up to 2 years in patients without disease progression.†
Metastatic or recurrent non-small cell lung cancer | 1 mg/kg every 6 weeks; with nivolumab 360 mg every 3 weeks; and histology-based platinum‑doublet; chemotherapy every 3 weeks | In combination with nivolumab until disease progression, unacceptable toxicity, or up to 2 years in patients without disease progression.†
Metastatic or recurrent non-small cell lung cancer | 1 mg/kg every 6 weeks; with nivolumab 360 mg every 3 weeks; and histology-based platinum‑doublet; chemotherapy every 3 weeks | 2 cycles of histology-based platinum-doublet chemotherapy
Malignant pleural mesothelioma | 1 mg/kg every 6 weeks; with nivolumab 360 mg every 3 weeks | In combination with nivolumab until disease progression, unacceptable toxicity, or up to 2 years in patients without disease progression.†
Esophageal squamous cell carcinoma | 1 mg/kg every 6 weeks with nivolumab 3 mg/kg every 2 weeks or 360 mg every 3 weeks | In combination with nivolumab until disease progression, unacceptable toxicity, or up to 2 years.
* Refer to the Prescribing Information for the agents administered in combination with YERVOY for recommended dosing information, as appropriate.
† Refer to the Prescribing Information for nivolumab for dosage information after completing use in combination with YERVOY.

2.3 Recommended Dosage Modifications for Adverse Reactions

No dose reduction for YERVOY is recommended. In general, withhold YERVOY for severe (Grade 3) immune-mediated adverse reactions. Permanently discontinue YERVOY for life-threatening (Grade 4) immune-mediated adverse reactions, recurrent severe (Grade 3) immune-mediated reactions that require systemic immunosuppressive treatment, persistent moderate (Grade 2) or severe (Grade 3) reactions lasting 12 weeks or longer after last YERVOY dose (excluding endocrinopathy), or an inability to reduce corticosteroid dose to 10 mg or less of prednisone or equivalent per day within 12 weeks of initiating steroids. Dosage modifications for YERVOY or YERVOY in combination with nivolumab for adverse reactions that require management different from these general guidelines are summarized in Table 3.

When YERVOY is administered in combination with nivolumab, withhold or permanently discontinue both YERVOY and nivolumab for toxicity.

Table 3: Recommended Dosage Modifications for Adverse Reactions
Adverse Reaction | Severity* | Dosage Modifications
Immune-Mediated Adverse Reactions [See Warnings and Precautions (5.1)]
Colitis | Grade 2 | Withholda
Colitis | Grade 3 or 4 | Permanently discontinue
Hepatitis with no tumor involvement of the liver; or; Hepatitis with tumor involvement of the liver/non-HCC | AST or ALT increases to more than 3 times and up to 5 times the ULN; or; Total bilirubin increases to more than 1.5 times and up to 3 times the ULN | Withholda
Hepatitis with no tumor involvement of the liver; or; Hepatitis with tumor involvement of the liver/non-HCC | AST or ALT more than 5 times the ULN; or; Total bilirubin more than 3 times the ULN | Permanently discontinue
Hepatitis with tumor involvement of the liverb/HCCc | Baseline AST/ALT is more than 1 and up to 3 times ULN and increases to more than 5 and up to 10 times ULN; or; Baseline AST/ALT is more than 3 and up to 5 times ULN and increases to more than 8 and up to 10 times ULN. | Withholda
Hepatitis with tumor involvement of the liverb/HCCc | AST/ALT increases to more than 10 times ULN; or; Total bilirubin increases to more than 3 times ULN. | Permanently discontinue
Exfoliative Dermatologic Conditions | Suspected SJS, TEN, or DRESS | Withhold
Exfoliative Dermatologic Conditions | Confirmed SJS, TEN, or DRESS | Permanently discontinue
Endocrinopathiesd | Grades 3 or 4 | Withhold until clinically stable or permanently discontinue depending on severity
Pneumonitis | Grade 2 | Withholda
Pneumonitis | Grade 3 or 4 | Permanently discontinue
Nephritis with Renal Dysfunction | Grade 2 or 3 increased blood creatinine | Withholda
Nephritis with Renal Dysfunction | Grade 4 increased blood creatinine | Permanently discontinue
Neurological Toxicities | Grade 2 | Withholda
Neurological Toxicities | Grade 3 or 4 | Permanently discontinue
Myocarditis | Grade 2, 3 or 4 | Permanently discontinue
Ophthalmologic | Grade 2, 3, or 4 that does not improve to Grade 1 within 2 weeks while receiving topical therapy or that requires systemic treatment | Permanently discontinue
Other Adverse Reactions
Infusion-Related Reactions [see Warnings and Precautions (5.2)] | Grade 1 or 2 | Interrupt or slow the rate of infusion
Infusion-Related Reactions [see Warnings and Precautions (5.2)] | Grade 3 or 4 | Permanently discontinue
ALT = alanine aminotransferase, AST = aspartate aminotransferase, DRESS = Drug Rash with Eosinophilia and Systemic Symptoms, SJS = Stevens Johnson Syndrome, TEN = toxic epidermal necrolysis, ULN = upper limit of normal
* Based on Common Terminology Criteria for Adverse Events (CTCAE), Version 4.03
a Resume in patients with complete or partial resolution (Grade 0 or 1) after corticosteroid taper. Permanently discontinue if no complete or partial resolution within 12 weeks of last dose or inability to reduce prednisone to 10 mg per day (or equivalent) or less within 12 weeks of initiating steroids.
b If AST/ALT are less than or equal to ULN at baseline, withhold or permanently discontinue YERVOY based on recommendations for hepatitis with no liver involvement.
c This guidance is only applicable to HCC patients who are being treated with YERVOY in combination with nivolumab.
d Depending on clinical severity, consider withholding for Grade 2 endocrinopathy until symptom improvement with hormone replacement. Resume once acute symptoms have resolved.

2.4 Preparation and Administration

- Do not shake product.
- Visually inspect for particulate matter and discoloration prior to administration. Discard vial if solution is cloudy, there is pronounced discoloration (solution may have pale-yellow color), or there is foreign particulate matter other than translucent-to-white, amorphous particles.

Preparation of Solution

- Allow the vial(s) to stand at room temperature for approximately 5 minutes prior to preparation of infusion.
- Withdraw the required volume of YERVOY and transfer into an intravenous bag.
- Dilute with 0.9% Sodium Chloride Injection, USP or 5% Dextrose Injection, USP to a final concentration ranging from 1 mg/mL to 2 mg/mL. Mix diluted solution by gentle inversion.
- After preparation, store the diluted solution either refrigerated at 2°C to 8°C (36°F to 46°F) or at room temperature of 20°C to 25°C (68°F to 77°F) for no more than 24 hours from the time of preparation to the time of infusion.
- Discard partially used or empty vials of YERVOY.

Administration

- Do not co-administer other drugs through the same intravenous line.
- Flush the intravenous line with 0.9% Sodium Chloride Injection, USP or 5% Dextrose Injection, USP after each dose.
- Administer diluted YERVOY solution by intravenous infusion over 30 minutes through an intravenous line containing a sterile, non-pyrogenic, low-protein-binding in-line filter.
- When administered in combination with nivolumab, infuse nivolumab first followed by YERVOY on the same day.
- When administered with nivolumab and platinum-doublet chemotherapy, infuse nivolumab first followed by YERVOY and then platinum-doublet chemotherapy on the same day.
- Use separate infusion bags and filters for each infusion.

3 DOSAGE FORMS AND STRENGTHS

Injection: 50 mg/10 mL (5 mg/mL) and 200 mg/40 mL (5 mg/mL) as a clear to slightly opalescent, colorless to pale-yellow solution in a single-dose vial.

4 CONTRAINDICATIONS

None.

5 WARNINGS AND PRECAUTIONS

5.1 Severe and Fatal Immune-Mediated Adverse Reactions

YERVOY is a fully human monoclonal antibody that blocks T-cell inhibitory signals induced by the CTLA-4 pathway, thereby removing inhibition of the immune response with the potential for induction of immune-mediated adverse reactions. Immune-mediated adverse reactions listed herein may not be inclusive of all possible severe and fatal immune-mediated reactions.

Immune-mediated adverse reactions, which may be severe or fatal, can occur in any organ system or tissue. Immune-mediated adverse reactions can occur at any time after starting YERVOY. While immune-mediated adverse reactions usually manifest during treatment, immune-mediated adverse reactions can also manifest after discontinuation of YERVOY.

Early identification and management are essential to ensure safe use of YERVOY. Monitor for signs and symptoms that may be clinical manifestations of underlying immune-mediated adverse reactions. Evaluate clinical chemistries including liver enzymes, creatinine, adrenocorticotropic hormone (ACTH) level, and thyroid function at baseline and before each dose. Institute medical management promptly, including specialty consultation as appropriate.

Withhold or permanently discontinue YERVOY depending on severity [see Dosage and Administration (2.3)]. In general, if YERVOY requires interruption or discontinuation, administer systemic corticosteroid therapy (1 to 2 mg/kg/day prednisone or equivalent) until improvement to Grade 1 or less. Upon improvement to Grade 1 or less, initiate corticosteroid taper and continue to taper over at least 1 month. Consider administration of other systemic immunosuppressants in patients whose immune-mediated adverse reactions are not controlled with corticosteroid therapy.

Immune-Mediated Colitis

YERVOY can cause immune-mediated colitis, which may be fatal. Cytomegalovirus (CMV) infection/reactivation has been reported in patients with corticosteroid-refractory immune-mediated colitis. In cases of corticosteroid-refractory colitis, consider repeating infectious workup to exclude alternative etiologies.

YERVOY 3 mg/kg as a Single Agent

Immune-mediated colitis occurred in 12% (62/511) of patients who received YERVOY 3 mg/kg as a single agent, including Grade 3-5 (7%) and Grade 2 (5%). Colitis led to permanent discontinuation of YERVOY in 4.3% and withholding of at least one dose of YERVOY in 0.2% of patients.

Systemic corticosteroids were required in 74% (46/62) of patients with immune-mediated colitis. Five patients required coadministration of another immunosuppressant with corticosteroids. Colitis resolved in 76% of the 62 patients. One patient was withheld one or more doses of YERVOY for colitis, and no patient received additional treatment after symptom improvement.

YERVOY 1 mg/kg with 3 mg/kg Nivolumab

Immune-mediated colitis occurred in 9% (60/666) of patients who received YERVOY 1 mg/kg with nivolumab for the treatment of RCC or mCRC, including Grade 3 (4.4%), and Grade 2 (3.7%). Colitis led to permanent discontinuation of YERVOY and nivolumab in 3.2% and withholding of YERVOY and nivolumab in 2.7% of patients.

In patients who received YERVOY 1 mg/kg with nivolumab, use of systemic corticosteroids was one of the diagnostic criteria required to identify immune-mediated colitis. Systemic corticosteroids were therefore required in 100% (60/60) of patients with immune-mediated colitis. Approximately 23% of patients required coadministration of another immunosuppressant with corticosteroids. Colitis resolved in 95% of the 60 patients. Of the 18 patients in whom YERVOY or nivolumab was withheld for colitis, 16 received additional treatment after symptom improvement; of these, 10 had recurrence of colitis.

YERVOY 3 mg/kg with 1 mg/kg Nivolumab

Immune-mediated colitis occurred in 25% (115/456) of patients with melanoma or HCC receiving YERVOY 3 mg/kg with nivolumab 1 mg/kg every 3 weeks, including Grade 4 (0.4%), Grade 3 (14%), and Grade 2 (8%) adverse reactions. Colitis led to permanent discontinuation of YERVOY with nivolumab in 14% and withholding of treatment in 4.4% of patients.

Systemic corticosteroids were required in 100% (115/115) of patients with colitis. Approximately 23% of patients required addition of infliximab to high-dose corticosteroids. Colitis resolved in 93% of 115 patients. Of the 20 patients in whom YERVOY with nivolumab was withheld for colitis, 16 reinitiated treatment after symptom improvement, and 9 had recurrence of colitis.

Immune-Mediated Hepatitis

YERVOY 3 mg/kg as a Single Agent

Immune-mediated hepatitis occurred in 4.1% (21/511) of patients who received YERVOY 3 mg/kg as a single agent, including Grade 3-5 (1.6%) and Grade 2 (2.5%). Hepatitis led to permanent discontinuation of YERVOY in 0.4% of patients and withholding of at least one dose of YERVOY in none of the patients.

Systemic corticosteroids were required in 29% (6/21) of patients with immune-mediated hepatitis. No patients required the coadministration of another immunosuppressant with corticosteroids. Hepatitis resolved in 86% of the 21 patients.

YERVOY 3 mg/kg with Vemurafenib

The safety and effectiveness of YERVOY in combination with vemurafenib have not been established [see Indications and Usage (1)]. In a dose-finding trial, Grade 3 increases in transaminases with or without concomitant increases in total bilirubin occurred in 6 of 10 patients who received concurrent YERVOY (3 mg/kg) and vemurafenib (960 mg or 720 mg twice daily).

YERVOY 1 mg/kg with 3 mg/kg Nivolumab

Immune-mediated hepatitis occurred in 7% (48/666) of patients who received YERVOY 1 mg/kg with nivolumab for the treatment of RCC or mCRC, including Grade 4 (1.2%), Grade 3 (4.9%), and Grade 2 (0.4%). Hepatitis led to permanent discontinuation of YERVOY and nivolumab in 3.6% and withholding of YERVOY and nivolumab in 2.6% of patients.

In patients who received YERVOY 1 mg/kg with nivolumab, use of systemic corticosteroids was one of the diagnostic criteria required to identify immune-mediated hepatitis. Systemic corticosteroids were therefore required in 100% (48/48) of patients with immune-mediated hepatitis. Approximately 19% of patients required coadministration of another immunosuppressant with corticosteroids. Hepatitis resolved in 88% of the 48 patients. Of the 17 patients in whom YERVOY or nivolumab was withheld for hepatitis, 14 received additional treatment after symptom improvement; of these, 10 had recurrence of hepatitis.

YERVOY 3 mg/kg with 1 mg/kg Nivolumab

Immune-mediated hepatitis occurred in 15% (70/456) of patients with melanoma or HCC receiving YERVOY 3 mg/kg with nivolumab 1 mg/kg every 3 weeks, including Grade 4 (2.4%), Grade 3 (11%), and Grade 2 (1.8%) adverse reactions. Immune-mediated hepatitis led to permanent discontinuation of YERVOY with nivolumab in 8% and withholding of treatment in 3.5% of patients.

Systemic corticosteroids were required in 100% (70/70) of patients with hepatitis. Approximately 9% of patients with immune-mediated hepatitis required addition of mycophenolic acid to high-dose corticosteroids. Hepatitis resolved in 91% of the 70 patients. Of the 16 patients in whom YERVOY with nivolumab was withheld for hepatitis, 14 reinitiated treatment after symptom improvement, and 8 had recurrence of hepatitis.

Immune-Mediated Dermatologic Adverse Reactions

YERVOY can cause immune-mediated rash or dermatitis, including bullous and exfoliative dermatitis, Stevens Johnson Syndrome, toxic epidermal necrolysis (TEN), and DRESS (Drug Rash with Eosinophilia and Systemic Symptoms). Topical emollients and/or topical corticosteroids may be adequate to treat mild to moderate non-bullous/exfoliative rashes. Withhold or permanently discontinue YERVOY depending on severity [see Dosage and Administration (2.3)].

YERVOY 3 mg/kg as a Single Agent

Immune-mediated rash occurred in 15% (76/511) of patients who received YERVOY 3 mg/kg as a single agent, including Grade 3-5 (2.5%) and Grade 2 (12%). Rash led to permanent discontinuation of YERVOY in 0.2% and withholding of at least one dose of YERVOY in 1.4% of patients.

Systemic corticosteroids were required in 43% (33/76) of patients with immune-mediated rash. Rash resolved in 71% of the 76 patients. Of the 7 patients in whom YERVOY was withheld for rash, 3 received additional treatment after symptom improvement; of these, 1 had recurrence of rash.

YERVOY 1 mg/kg with 3 mg/kg Nivolumab

Immune-mediated rash occurred in 16% (108/666) of patients who received YERVOY 1 mg/kg with nivolumab for the treatment of RCC or mCRC, including Grade 3 (3.5%) and Grade 2 (4.2%). Rash led to permanent discontinuation of YERVOY and nivolumab in 0.5% of patients and withholding of YERVOY and nivolumab in 2.0% of patients.

In patients who received YERVOY 1 mg/kg with nivolumab, use of systemic corticosteroids was one of the diagnostic criteria required to identify immune-mediated rash. Systemic corticosteroids were therefore required in 100% (108/108) of patients. Rash resolved in 75% of 108 patients. Of the 13 patients in whom YERVOY or nivolumab was withheld for rash, 11 received additional treatment after symptom improvement; of these, 5 had recurrence of rash.

YERVOY 3 mg/kg with 1 mg/kg Nivolumab

Immune-mediated rash occurred in 28% (127/456) of patients with melanoma or HCC receiving YERVOY 3 mg/kg with nivolumab 1 mg/kg every 3 weeks, including Grade 3 (4.8%) and Grade 2 (10%) adverse reactions. Immune-mediated rash led to permanent discontinuation of YERVOY with nivolumab in 0.4% and withholding of treatment in 3.9% of patients.

Systemic corticosteroids were required in 100% (127/127) of patients with immune-mediated rash. Rash resolved in 84% of the 127 of patients. Of the 18 patients in whom YERVOY with nivolumab was withheld for rash, 15 reinitiated treatment after symptom improvement, and 8 had recurrence of rash.

Immune-Mediated Endocrinopathies

YERVOY 3 mg/kg as a Single Agent

Grade 2-5 immune-mediated endocrinopathies occurred in 4% (21/511) of patients who received YERVOY 3 mg/kg as a single agent.

Severe to life-threatening (Grade 3-4) endocrinopathies occurred in 9 patients (1.8%). All 9 of these patients had hypopituitarism with some patients having additional concomitant endocrinopathies, such as adrenal insufficiency, hypogonadism, and hypothyroidism. Six of the 9 patients were hospitalized for severe endocrinopathies.

Moderate (Grade 2) endocrinopathy occurred in 12 patients (2.3%), including hypothyroidism, adrenal insufficiency, hypopituitarism, hyperthyroidism and Cushing’s syndrome.

Of the 21 patients with moderate to life-threatening endocrinopathy, 17 required long-term hormone replacement therapy, including adrenal hormones (n=10) and thyroid hormones (n=13).

YERVOY 1 mg/kg with 3 mg/kg Nivolumab

Hypophysitis:

YERVOY can cause immune-mediated hypophysitis. Hypophysitis can present with acute symptoms associated with mass effect such as headache, photophobia, or visual field cuts. Hypophysitis can cause hypopituitarism. Initiate hormone replacement as clinically indicated. Withhold or permanently discontinue YERVOY depending on severity [see Dosage and Administration (2.3)].

Hypophysitis occurred in 4.4% (29/666) of patients who received YERVOY 1 mg/kg with nivolumab for the treatment of RCC or mCRC, including Grade 4 (0.3%), Grade 3 (2.4%), and Grade 2 (0.9%). Hypophysitis led to permanent discontinuation of YERVOY and nivolumab in 1.2% and withholding of YERVOY with nivolumab in 2.1% of patients. Approximately 72% of patients with hypophysitis received hormone replacement therapy. Systemic corticosteroids were required in 72% (21/29) of patients with immune-mediated hypophysitis. Hypophysitis resolved in 59% of the 29 patients. Of the 14 patients in whom YERVOY or nivolumab was withheld for hypophysitis, 11 received additional treatment after symptom improvement; of these, 2 had recurrence of hypophysitis.

Adrenal Insufficiency:

Adrenal insufficiency occurred in 7% (48/666) of patients who received YERVOY 1 mg/kg with nivolumab for the treatment of RCC or mCRC, including Grade 4 (0.3%), Grade 3 (2.5%), and Grade 2 (4.1%). Adrenal insufficiency led to permanent discontinuation of YERVOY with nivolumab in 1.2% and withholding of YERVOY with nivolumab in 2.1% of patients. Approximately 94% of patients with adrenal insufficiency received hormone replacement therapy. Systemic corticosteroids were required in 94% (45/48) of patients with adrenal insufficiency. Adrenal insufficiency resolved in 29% of the 48 patients. Of the 14 patients in whom YERVOY or nivolumab was withheld for adrenal insufficiency, 11 received additional treatment after symptom improvement; of these, 2 had recurrence of adrenal insufficiency.

Hyperthyroidism:

Hyperthyroidism occurred in 12% (80/666) of patients who received YERVOY 1 mg/kg with nivolumab for the treatment of RCC or mCRC, including Grade 3 (0.6%) and Grade 2 (4.5%). No patients discontinued YERVOY for hyperthyroidism. Hyperthyroidism led to withholding of YERVOY with nivolumab in 2.3% of patients. Approximately 19% received a thyroid synthesis inhibitor. Systemic corticosteroids were required in 20% (16/80) of patients with hyperthyroidism. Hyperthyroidism resolved in 85% of the 80 patients. Of the 15 patients in whom YERVOY or nivolumab was withheld for hyperthyroidism, 11 received additional treatment after symptom improvement; of these, 3 had recurrence of hyperthyroidism.

Hypothyroidism:

Hypothyroidism occurred in 18% (122/666) of patients who received YERVOY 1 mg/kg with nivolumab for the treatment of RCC or mCRC, including Grade 3 (0.6%) and Grade 2 (11%). Hypothyroidism led to permanent discontinuation of YERVOY with nivolumab in 0.2% and withholding of YERVOY with nivolumab in 1.4% of patients. Approximately 82% received thyroid hormone replacement. Systemic corticosteroids were required in 7% (9/122) of patients with hypothyroidism. Hypothyroidism resolved in 27% of the 122 patients. Of the 9 patients in whom YERVOY or nivolumab was withheld for hypothyroidism, 5 received additional treatment after symptom improvement; of these, one patient had recurrence of hypothyroidism.

Thyroiditis:

Thyroiditis occurred in 2.7% (22/666) of patients who received YERVOY 1 mg/kg with nivolumab for the treatment of RCC or mCRC, including Grade 3 (4.5%) and Grade 2 (2.2%). Thyroiditis led to permanent discontinuation of YERVOY with nivolumab in 0.2% and withholding of YERVOY with nivolumab in 0.8% of patients. Systemic corticosteroids were required in 18% (4/22) of patients with thyroiditis. Thyroiditis resolved in 64% of the 22 patients. Of the 5 patients in whom YERVOY or nivolumab was withheld for thyroiditis, 5 received additional treatment after symptom improvement; of these, no patients had recurrence of thyroiditis.

Type 1 Diabetes Mellitus:

Diabetes occurred in 2.7% (15/666) of patients who received YERVOY 1 mg/kg with nivolumab for the treatment of RCC or mCRC, including Grade 4 (0.6%), Grade 3 (0.3%), and Grade 2 (0.9%). Diabetes led to the permanent discontinuation of YERVOY with nivolumab in 0.5% and withholding of YERVOY with nivolumab in 0.5% of patients. Systemic corticosteroids were required in 7% (1/15) of patients with diabetes. Diabetes resolved in 27% of the 15 patients. Of the 3 patients in whom YERVOY or nivolumab was withheld for diabetes, 2 received additional treatment after symptom improvement; of these, none had recurrence of diabetes.

YERVOY 3 mg/kg with 1 mg/kg Nivolumab

Hypophysitis:

Hypophysitis occurred in 9% (42/456) of patients with melanoma or HCC receiving YERVOY 3 mg/kg with nivolumab 1 mg/kg every 3 weeks, including Grade 3 (2.4%) and Grade 2 (6%) adverse reactions. Hypophysitis led to permanent discontinuation of YERVOY with nivolumab in 0.9% and withholding of treatment in 4.2% of patients.

Approximately 86% of patients with hypophysitis received hormone replacement therapy. Systemic corticosteroids were required in 88% (37/42) of patients with hypophysitis. Hypophysitis resolved in 38% of the 42 patients. Of the 19 patients in whom YERVOY with nivolumab was withheld for hypophysitis, 9 reinitiated treatment after symptom improvement, and 1 had recurrence of hypophysitis.

Adrenal Insufficiency:

Adrenal insufficiency occurred in 8% (35/456) of patients with melanoma or HCC receiving YERVOY 3 mg/kg with nivolumab 1 mg/kg every 3 weeks, including Grade 4 (0.2%), Grade 3 (2.4%), and Grade 2 (4.2%) adverse reactions. Adrenal insufficiency led to permanent discontinuation of YERVOY with nivolumab in 0.4% of patients and withholding of treatment in 2.0% of patients.

Approximately 71% (25/35) of patients with adrenal insufficiency received hormone replacement therapy, including systemic corticosteroids. Adrenal insufficiency resolved in 37% of the 35 patients. Of the 9 patients in whom YERVOY with nivolumab was withheld for adrenal insufficiency, 7 reinitiated treatment after symptom improvement, and all required hormone replacement therapy for their ongoing adrenal insufficiency.

Hypothyroidism:

Hypothyroidism occurred in 20% (91/456) of patients with melanoma or HCC receiving YERVOY 3 mg/kg with nivolumab 1 mg/kg every 3 weeks, including Grade 3 (0.4%) and Grade 2 (11%) adverse reactions. Hypothyroidism led to permanent discontinuation of YERVOY with nivolumab in 0.9% of patients and withholding of treatment in 0.9% of patients.

Approximately 89% of patients with hypothyroidism received levothyroxine. Systemic corticosteroids were required in 2.2% (2/91) of patients with hypothyroidism. Hypothyroidism resolved in 41% of the 91 patients. Of the 4 patients in whom YERVOY with nivolumab was withheld for hypothyroidism, 2 reinitiated treatment after symptom improvement, and none had recurrence of hypothyroidism.

Hyperthyroidism:

Hyperthyroidism occurred in 9% (42/456) of patients with melanoma or HCC receiving YERVOY 3 mg/kg with nivolumab 1 mg/kg every 3 weeks, including Grade 3 (0.9%) and Grade 2 (4.2%) adverse reactions. Hyperthyroidism led to permanent discontinuation of YERVOY with nivolumab in no patients and withholding of treatment in 2.4% of patients.

Approximately 26% of patients with hyperthyroidism received methimazole and 21% received carbimazole. Systemic corticosteroids were required in 17% (7/42) of patients. Hyperthyroidism resolved in 91% of the 42 patients. Of the 11 patients in whom YERVOY with nivolumab was withheld for hyperthyroidism, 8 reinitiated treatment after symptom improvement, and 1 had recurrence of hyperthyroidism.

Immune-Mediated Pneumonitis

YERVOY 1 mg/kg with 3 mg/kg Nivolumab

Immune-mediated pneumonitis occurred in 3.9% (26/666) of patients who received YERVOY 1 mg/kg with nivolumab for the treatment of RCC or mCRC, including Grade 3 (1.4%) and Grade 2 (2.6%). Pneumonitis led to permanent discontinuation of YERVOY and nivolumab in 1.8% and withholding of YERVOY and nivolumab in 1.5% of patients.

In patients who received YERVOY 1 mg/kg with nivolumab, use of systemic corticosteroids was one of the diagnostic criteria required to identify immune-mediated pneumonitis. Systemic corticosteroids were therefore required in 100% (26/26) of patients with immune-mediated pneumonitis. Approximately 8% required coadministration of another immunosuppressant with corticosteroids. Pneumonitis resolved in 92% of the 26 patients. Of the 10 patients in whom YERVOY or nivolumab was withheld for pneumonitis, 10 received additional treatment after symptom improvement; of these, 4 had recurrence of pneumonitis.

In NSCLC, immune-mediated pneumonitis occurred in 9% (50/576) of patients receiving YERVOY 1 mg/kg every 6 weeks with nivolumab 3 mg/kg every 2 weeks, including Grade 4 (0.5%), Grade 3 (3.5%), and Grade 2 (4.0%) immune-mediated pneumonitis. Four patients (0.7%) died due to pneumonitis. The median duration was 1.5 months (range: 5 days to 25+ months). Immune-mediated pneumonitis led to permanent discontinuation of YERVOY with nivolumab in 5% of patients and withholding of YERVOY with nivolumab in 3.6% of patients.

Systemic corticosteroids were required in 100% of patients with pneumonitis followed by a corticosteroid taper. Pneumonitis resolved in 72% of the patients. Approximately 13% (2/16) of patients had recurrence of pneumonitis after re-initiation of YERVOY with nivolumab.

YERVOY 3 mg/kg with 1 mg/kg Nivolumab

Immune-mediated pneumonitis occurred in 7% (31/456) of patients who received YERVOY 3 mg/kg with nivolumab for the treatment of HCC or melanoma, including Grade 4 (0.2%), Grade 3 (2.0%), and Grade 2 (4.4%). Immune-mediated pneumonitis led to permanent discontinuation or withholding of treatment in 2.9% and 3.9% of patients, respectively.

Systemic corticosteroids were required in 100% of patients with pneumonitis. Pneumonitis resolved in 94% of the patients. Of the 13 patients in whom YERVOY or nivolumab was withheld for pneumonitis, 13 received additional treatment after symptom improvement, and 4 had recurrence of pneumonitis.

Immune-Mediated Nephritis with Renal Dysfunction

YERVOY 1 mg/kg with 3 mg/kg Nivolumab

Immune-mediated nephritis with renal dysfunction occurred in 4.1% (27/666) of patients who received YERVOY 1 mg/kg with nivolumab for the treatment of RCC or mCRC, including Grade 4 (0.6%), Grade 3 (1.1%), and Grade 2 (2.2%). Nephritis with renal dysfunction led to permanent discontinuation of YERVOY and nivolumab in 1.2% and withholding of nivolumab and YERVOY in 1.8% of patients.

In patients who received YERVOY 1 mg/kg with nivolumab, use of systemic corticosteroids was one of the diagnostic criteria required to identify immune-mediated nephritis with renal dysfunction. Systemic corticosteroids were therefore required in 100% (27/27) of patients with immune-mediated nephritis with renal dysfunction. Nephritis with renal dysfunction resolved in 67% of the 27 patients. Of the 12 patients in whom YERVOY or nivolumab was withheld for nephritis, 10 received additional treatment after symptom improvement; of these, 4 had recurrence of nephritis.

Other Immune-Mediated Adverse Reactions

Across clinical trials of YERVOY administered as a single agent or in combination with nivolumab, the following clinically significant immune-mediated adverse reactions, some with fatal outcome, occurred in <1% of patients unless otherwise specified, as shown below:

Nervous System: Autoimmune neuropathy (2%), meningitis, encephalitis, myelitis and demyelination, myasthenic syndrome/myasthenia gravis, Guillain-Barré syndrome, nerve paresis, motor dysfunction

Cardiovascular: Angiopathy, myocarditis, pericarditis, temporal arteritis, vasculitis

Ocular: Blepharitis, episcleritis, iritis, orbital myositis, scleritis, uveitis. Some cases can be associated with retinal detachment. If uveitis occurs in combination with other immune-mediated adverse reactions, consider a Vogt-Koyanagi-Harada-like syndrome, which has been observed in patients receiving YERVOY and may require treatment with systemic corticosteroids to reduce the risk of permanent vision loss.

Gastrointestinal: Duodenitis, gastritis, pancreatitis (1.3%)

Musculoskeletal and Connective Tissue: Arthritis, myositis, polymyalgia rheumatica, polymyositis, rhabdomyolysis

Other (hematologic/immune): Aplastic anemia, conjunctivitis, cytopenias (2.5%), eosinophilia (2.1%), erythema multiforme, histiocytic necrotizing lymphadenitis (Kikuchi lymphadenitis), hypersensitivity vasculitis, meningitis, neurosensory hypoacusis, psoriasis, sarcoidosis, systemic inflammatory response syndrome, and solid organ transplant rejection.

5.2 Infusion-Related Reactions

Severe infusion-related reactions can occur with YERVOY. Discontinue YERVOY in patients with severe or life-threatening infusion reactions. Interrupt or slow the rate of infusion in patients with mild or moderate infusion reactions [see Dosage and Administration (2.3)]. Infusion-related reactions occurred in 0.6% (3/511) of patients who received single-agent YERVOY 3 mg/kg for the unresectable or metastatic treatment of melanoma. Infusion-related reactions occurred in 5% (33/666) of patients who received YERVOY 1 mg/kg with nivolumab for the treatment of RCC or CRC. Infusion-related reactions occurred in 8% (4/49) of patients who received YERVOY 3 mg/kg with nivolumab for the treatment of HCC. Infusion-related reactions occurred in 12% (37/300) of patients with malignant pleural mesothelioma who received YERVOY 1 mg/kg every 6 weeks with nivolumab 3 mg/kg every 2 weeks.

5.3 Complications of Allogeneic Hematopoietic Stem Cell Transplant after YERVOY

Fatal or serious graft-versus-host disease (GVHD) can occur in patients who receive YERVOY either before or after allogeneic hematopoietic stem cell transplantation (HSCT). These complications may occur despite intervening therapy between CTLA-4 receptor blocking antibody and allogeneic HSCT.

Follow patients closely for evidence of GVHD and intervene promptly [see Adverse Reactions (6.2)]. Consider the benefit versus risks of treatment with YERVOY after allogeneic HSCT.

5.4 Embryo-Fetal Toxicity

Based on its mechanism of action and findings from animal studies, YERVOY can cause fetal harm when administered to a pregnant woman. In animal reproduction studies, administration of ipilimumab to cynomolgus monkeys from the onset of organogenesis through delivery resulted in higher incidences of abortion, stillbirth, premature delivery (with corresponding lower birth weight) and higher incidences of infant mortality in a dose-related manner. The effects of ipilimumab are likely to be greater during the second and third trimesters of pregnancy. Advise pregnant women of the potential risk to a fetus. Advise females of reproductive potential to use effective contraception during treatment with YERVOY and for 3 months after the last dose [see Use in Specific Populations (8.1, 8.3)].

5.5 Risks Associated When Administered in Combination with Nivolumab

YERVOY is indicated for use in combination with nivolumab for patients with advanced RCC, MSI-H or dMMR mCRC, HCC, and NSCLC. Refer to the nivolumab Full Prescribing Information for additional risk information that applies to the combination use treatment.

6 ADVERSE REACTIONS

The following clinically significant adverse reactions are described elsewhere in the labeling:

- Severe and fatal immune-mediated adverse reactions [see Warnings and Precautions (5.1)].
- Infusion-related reactions [see Warnings and Precautions (5.2)].

6.1 Clinical Trials Experience

Because clinical trials are conducted under widely varying conditions, adverse reaction rates observed in the clinical trials of a drug cannot be directly compared with rates in the clinical trials of another drug and may not reflect the rates observed in clinical practice.

The data described in the Warnings and Precautions section reflect exposure to YERVOY 3 mg/kg as a single agent (or in combination with an investigational gp100 peptide vaccine) in 511 patients in Study MDX010-20; YERVOY 1 mg/kg administered with nivolumab 3 mg/kg in 1,362 patients in CHECKMATE-214, CHECKMATE-142, CHECKMATE-227, and CHECKMATE-743; YERVOY 3 mg/kg administered with nivolumab 1 mg/kg in 456 patients enrolled in CHECKMATE-067, CHECKMATE-040, and another randomized trial; and to YERVOY 1 mg/kg, administered in combination with nivolumab and platinum-doublet chemotherapy in CHECKMATE-9LA.

Unresectable or Metastatic Melanoma

The safety of YERVOY was evaluated in 643 previously treated patients with unresectable or metastatic melanoma in Study MDX010-20 [see Clinical Studies (14.1)]. Study MDX010-20 excluded patients with active autoimmune disease or those receiving systemic immunosuppression for organ transplantation. Patients received YERVOY 3 mg/kg by intravenous infusion for 4 doses as a single agent (n=131), YERVOY with an investigational gp100 peptide vaccine (n=380), or gp100 peptide vaccine as a single agent (n=132). Patients in the trial received a median of 4 doses (range: 1 to 4 doses).

The trial population characteristics were: median age 57 years (range: 19 to 90), 59% male, 94% White, and baseline ECOG performance status 0 (56%).

YERVOY was discontinued for adverse reactions in 10% of patients. Table 4 presents adverse reactions from Study MDX010-20.

Table 4: Selected Adverse Reactions (≥5%) in Patients Receiving YERVOY with a Difference Between Arms of >5% for All Grades and >1% for Grades 3 to 5 Compared to gp100 Peptide Vaccine in Study MDX010-20
Adverse Reactions | YERVOY 3 mg/kg n=131 |  | YERVOY 3 mg/kg and gp100; n=380 |  | gp100; n=132
Adverse Reactions | All Grades (%) | Grade 3 to 5 (%) | All Grades; (%) | Grade 3 to 5 (%) | All Grades (%) | Grade 3 to 5 (%)
General and Administration-Site Conditions
Fatigue | 41 | 7 | 34 | 5 | 31 | 3
Gastrointestinal
Diarrhea | 32 | 5 | 37 | 4 | 20 | 1
Colitis | 8 | 5 | 5 | 3 | 2 | 0
Dermatologic
Pruritus | 31 | 0 | 21 | <1 | 11 | 0
Rash | 29 | 2 | 25 | 2 | 8 | 0

Unresectable or Metastatic Melanoma: In Combination with Nivolumab

The safety of YERVOY, administered with nivolumab or as a single agent, was evaluated in CHECKMATE-067, a randomized (1:1:1), double-blind trial in 937 patients with previously untreated, unresectable or metastatic melanoma [see Clinical Studies (14.1)]. The trial excluded patients with autoimmune disease, a medical condition requiring systemic treatment with corticosteroids (more than 10 mg daily prednisone equivalent) or other immunosuppressive medication within 14 days of the start of study therapy, a positive test result for hepatitis B or C, or a history of HIV.

Patients were randomized to receive:

- YERVOY 3 mg/kg by intravenous infusion over 90 minutes with nivolumab 1 mg/kg by intravenous infusion every 3 weeks for 4 doses followed by nivolumab as a single agent at a dose of 3 mg/kg by intravenous infusion every 2 weeks (YERVOY and nivolumab arm; n=313), or
- Nivolumab 3 mg/kg by intravenous infusion every 2 weeks (nivolumab arm; n=313), or
- YERVOY 3 mg/kg by intravenous infusion over 90 minutes every 3 weeks for up to 4 doses (YERVOY arm; n=311).

The median duration of exposure to nivolumab was 2.8 months (range: 1 day to 36.4 months) for the YERVOY and nivolumab arm. In the YERVOY and nivolumab arm, 39% were exposed to nivolumab for ≥6 months and 30% exposed for >1 year.

Serious adverse reactions (74%), adverse reactions leading to permanent discontinuation (47%) or to dosing delays (58%), and Grade 3 or 4 adverse reactions (72%) occurred in patients treated with YERVOY and nivolumab.

The most frequent (≥10%) serious adverse reactions in the YERVOY and nivolumab arm were diarrhea (13%), colitis (10%), and pyrexia (10%). The most frequent adverse reactions leading to discontinuation of both drugs in the YERVOY and nivolumab arm were colitis (10%), diarrhea (8%), increased ALT (4.8%), increased AST (4.5%), and pneumonitis (1.9%).

The most common (≥20%) adverse reactions in the YERVOY and nivolumab arm were fatigue, diarrhea, rash, nausea, pyrexia, pruritus, musculoskeletal pain, vomiting, decreased appetite, cough, headache, dyspnea, upper respiratory tract infection, arthralgia, and increased transaminases.

Tables 5 and 6 summarize the incidence of adverse reactions and laboratory abnormalities, respectively, in CHECKMATE-067.

Table 5: Adverse Reactions Occurring in ≥10% of Patients on the YERVOY and Nivolumab Arm or the Nivolumab Arm and at a Higher Incidence than in the YERVOY Arm (Between Arm Difference of ≥5% All Grades or ≥2% Grades 3-4) - CHECKMATE-067
Adverse Reaction | YERVOY and Nivolumab (n=313) |  | Nivolumab; (n=313) |  | YERVOY; (n=311)
Adverse Reaction | All Grades (%) | Grades 3-4 (%) | All Grades (%) | Grades 3-4 (%) | All Grades (%) | Grades 3-4 (%)
General
Fatiguea | 62 | 7 | 59 | 1.6 | 51 | 4.2
Pyrexia | 40 | 1.6 | 16 | 0 | 18 | 0.6
Gastrointestinal
Diarrhea | 54 | 11 | 36 | 5 | 47 | 7
Nausea | 44 | 3.8 | 30 | 0.6 | 31 | 1.9
Vomiting | 31 | 3.8 | 20 | 1.0 | 17 | 1.6
Skin and Subcutaneous Tissue
Rashb | 53 | 6 | 40 | 1.9 | 42 | 3.5
Vitiligo | 9 | 0 | 10 | 0.3 | 5 | 0
Musculoskeletal and Connective Tissue
Musculoskeletal painc | 32 | 2.6 | 42 | 3.8 | 36 | 1.9
Arthralgia | 21 | 0.3 | 21 | 1.0 | 16 | 0.3
Metabolism and Nutrition
Decreased appetite | 29 | 1.9 | 22 | 0 | 24 | 1.3
Respiratory, Thoracic and Mediastinal
Cough/productive cough | 27 | 0.3 | 28 | 0.6 | 22 | 0
Dyspnea/exertional dyspnea | 24 | 2.9 | 18 | 1.3 | 17 | 0.6
Infections
Upper respiratory tract infectiond | 23 | 0 | 22 | 0.3 | 17 | 0
Endocrine
Hypothyroidism | 19 | 0.6 | 11 | 0 | 5 | 0
Hyperthyroidism | 11 | 1.3 | 6 | 0 | 1 | 0
Investigations
Decreased weight | 12 | 0 | 7 | 0 | 7 | 0.3
Vascular
Hypertensione | 7 | 2.2 | 11 | 5 | 9 | 2.3
Toxicity was graded per NCI CTCAE v4.
a Includes asthenia and fatigue.
b Includes pustular rash, dermatitis, acneiform dermatitis, allergic dermatitis, atopic dermatitis, bullous dermatitis, exfoliative dermatitis, psoriasiform dermatitis, drug eruption, exfoliative rash, erythematous rash, generalized rash, macular rash, maculopapular rash, morbilliform rash, papular rash, papulosquamous rash, and pruritic rash.
c Includes back pain, bone pain, musculoskeletal chest pain, musculoskeletal discomfort, myalgia, neck pain, pain in extremity, and spinal pain.
d Includes upper respiratory tract infection, nasopharyngitis, pharyngitis, and rhinitis.
e Includes hypertension and blood pressure increased.

Clinically important adverse reactions in <10% of patients who received YERVOY with nivolumab:

Gastrointestinal Disorders: stomatitis, intestinal perforation

Skin and Subcutaneous Tissue Disorders: vitiligo

Musculoskeletal and Connective Tissue Disorders: myopathy, Sjogren’s syndrome, spondyloarthropathy, myositis (including polymyositis)

Nervous System Disorders: neuritis, peroneal nerve palsy

Table 6: Laboratory Abnormalities Worsening from Baselinea Occurring in ≥20% of Patients Treated with YERVOY with Nivolumab or Single-Agent Nivolumab and at a Higher Incidence than in the YERVOY Arm (Between Arm Difference of ≥5% All Grades or ≥2% Grades 3-4) - CHECKMATE-067
Laboratory Abnormality | YERVOY and Nivolumab |  | Nivolumab |  | YERVOY
Laboratory Abnormality | All Grades (%) | Grade 3-4 (%) | All Grades (%) | Grade 3-4 (%) | All Grades (%) | Grade 3-4 (%)
Chemistry
Increased ALT | 55 | 16 | 25 | 3.0 | 29 | 2.7
Hyperglycemia | 53 | 5 | 46 | 7 | 26 | 0
Increased AST | 52 | 13 | 29 | 3.7 | 29 | 1.7
Hyponatremia | 45 | 10 | 22 | 3.3 | 26 | 7
Increased lipase | 43 | 22 | 32 | 12 | 24 | 7
Increased alkaline phosphatase | 41 | 6 | 27 | 2.0 | 23 | 2.0
Hypocalcemia | 31 | 1.1 | 15 | 0.7 | 20 | 0.7
Increased amylase | 27 | 10 | 19 | 2.7 | 15 | 1.6
Increased creatinine | 26 | 2.7 | 19 | 0.7 | 17 | 1.3
Hematology
Anemia | 52 | 2.7 | 41 | 2.6 | 41 | 6
Lymphopenia | 39 | 5 | 41 | 4.9 | 29 | 4.0
a Each test incidence is based on the number of patients who had both baseline and at least one on-study laboratory measurement available: YERVOY and nivolumab (range: 75 to 297); nivolumab (range: 81 to 306); YERVOY (range: 61 to 301)

Adjuvant Treatment of Melanoma

The safety of YERVOY was evaluated in Study E1609, an open-label, multicenter, randomized trial for the adjuvant treatment of patients with completely resected node positive cutaneous melanoma [see Clinical Studies (14.2)]. Patients received YERVOY 3 mg/kg intravenously every 3 weeks for 4 doses followed by 3 mg/kg every 12 weeks for up to 4 additional doses, or high-dose interferon-α2b (HDI). Among patients who received YERVOY, 55% were exposed for 6 months or longer and 42% were exposed for greater than 1 year.

Fatal adverse reactions occurred in 1.4% of patients who received YERVOY, including gastric perforation (0.2%), and cardiac arrest (0.2%). Permanent discontinuation of YERVOY due to an adverse reaction occurred in 35% of patients.

The most common adverse reactions (≥20%) in the YERVOY arm were fatigue, diarrhea, rash, pruritus, nausea, and headache. Table 7 summarizes adverse reactions in E1609.

Table 7: Adverse Reactions (>10%) in Patients Receiving YERVOY 3 mg/kg in E1609
Adverse Reaction | YERVOY 3 mg/kg n=516 |  | HDI n=520
Adverse Reaction | All Grades (%) | Grade 3 to 4 (%) | All Grades (%) | Grade 3 to 4 (%)
General disorders and administration site conditions
Fatigue | 56 | 3 | 87 | 22
Decreased appetite | 14 | 0.6 | 53 | 2.1
Pyrexia | 10 | 0 | 31 | 0.8
Gastrointestinal
Diarrhea | 49 | 10 | 34 | 0.8
Nausea | 29 | 1.2 | 66 | 4.2
Abdominal Pain | 19 | 1 | 9 | 0.4
Vomiting | 11 | 0.6 | 26 | 2.3
Colitis | 10 | 8 | 1 | 0.4
Dermatologic
Rash | 46 | 4 | 18 | 1
Pruritus | 41 | 2 | 15 | 0
Nervous System Disorders
Headache | 25 | 2 | 45 | 3
Endocrine
Endocrine disorders, other | 19 | 4.1 | 2 | 0
Hypothyroidism | 11 | 0.6 | 10 | 0.2
Adrenal insufficiency | 10 | 2 | 0.6 | 0

Other Clinical Experience

Across clinical studies in which patients received YERVOY as a single agent at doses ranging from 0.3 to 10 mg/kg, the following adverse reactions were also reported (incidence <1% unless otherwise noted): urticaria (2%), large intestinal ulcer, esophagitis, acute respiratory distress syndrome, renal failure, and infusion reaction.

Advanced Renal Cell Carcinoma: In Combination with Nivolumab

The safety of YERVOY in combination with nivolumab was evaluated in 1082 patients with previously untreated advanced RCC in CHECKMATE-214 [see Clinical Studies (14.3)]. Patients received YERVOY 1 mg/kg with nivolumab 3 mg/kg intravenously every 3 weeks for 4 doses followed by nivolumab as a single agent at a dose of 3 mg/kg every 2 weeks (n=547) or sunitinib 50 mg orally daily for first 4 weeks of each 6-week cycle (n=535). The median duration of treatment was 7.9 months (range: 1 day to 21.4+ months) in YERVOY and nivolumab arm. In this trial, 57% of patients in the YERVOY and nivolumab arm were exposed to treatment for greater than 6 months and 38% of patients were exposed to treatment for greater than 1 year.

Serious adverse reactions occurred in 59% of patients receiving YERVOY with nivolumab. The most frequent serious adverse reactions reported in ≥2% of patients treated with YERVOY and nivolumab were diarrhea, pyrexia, pneumonia, pneumonitis, hypophysitis, acute kidney injury, dyspnea, adrenal insufficiency, and colitis.

In patients who received YERVOY with nivolumab, study therapy was discontinued for adverse reactions in 31% and delayed for adverse reactions in 54%.

The most common adverse reactions (≥20%) in the YERVOY and nivolumab arm were fatigue, rash, diarrhea, musculoskeletal pain, pruritus, nausea, cough, pyrexia, arthralgia, vomiting, dyspnea, and decreased appetite. Table 8 summarizes adverse reactions in CHECKMATE-214.

Table 8: Adverse Reactions (>15%) in Patients Receiving YERVOY and Nivolumab in CHECKMATE-214
Adverse Reaction | YERVOY 1 mg/kg and Nivolumab n=547 |  | Sunitinib n=535
Adverse Reaction | Grades 1-4; (%) | Grades 3-4; (%) | Grades 1-4; (%) | Grades 3-4; (%)
General and Administration Site Conditions
Fatiguea | 58 | 8 | 69 | 13
Pyrexia | 25 | 0.7 | 17 | 0.6
Edemab | 16 | 0.5 | 17 | 0.6
Skin and Subcutaneous Tissue
Rashc | 39 | 3.7 | 25 | 1.1
Pruritus/generalized pruritus | 33 | 0.5 | 11 | 0
Gastrointestinal
Diarrhea | 38 | 4.6 | 58 | 6
Nausea | 30 | 2.0 | 43 | 1.5
Vomiting | 20 | 0.9 | 28 | 2.1
Abdominal pain | 19 | 1.6 | 24 | 1.9
Constipation | 17 | 0.4 | 18 | 0
Musculoskeletal and Connective Tissue
Musculoskeletal paind | 37 | 4.0 | 40 | 2.6
Arthralgia | 23 | 1.3 | 16 | 0
Respiratory, Thoracic, and Mediastinal
Cough/productive cough | 28 | 0.2 | 25 | 0.4
Dyspnea/exertional dyspnea | 20 | 2.4 | 21 | 2.1
Metabolism and Nutrition
Decreased appetite | 21 | 1.8 | 29 | 0.9
Nervous System
Headache | 19 | 0.9 | 23 | 0.9
Endocrine
Hypothyroidism | 18 | 0.4 | 27 | 0.2
Toxicity was graded per NCI CTCAE v4.
a Includes asthenia.
b Includes peripheral edema, peripheral swelling.
c Includes dermatitis described as acneiform, bullous, and exfoliative, drug eruption, rash described as exfoliative, erythematous, follicular, generalized, macular, maculopapular, papular, pruritic, and pustular, fixed-drug eruption.
d Includes back pain, bone pain, musculoskeletal chest pain, musculoskeletal discomfort, myalgia, neck pain, pain in extremity, spinal pain.

Table 9 summarizes the laboratory abnormalities in CHECKMATE-214.

Table 9: Laboratory Abnormalities (>15%) Worsening from Baseline in Patients Receiving YERVOY and Nivolumab in CHECKMATE-214
Laboratory Abnormality | YERVOY 1 mg/kg and Nivolumaba |  | Sunitiniba
Laboratory Abnormality | Grades 1-4 (%) | Grades 3-4 (%) | Grades 1-4 (%) | Grades 3-4 (%)
Chemistry
Increased lipase | 48 | 20 | 51 | 20
Increased creatinine | 42 | 2.1 | 46 | 1.7
Increased ALT | 41 | 7 | 44 | 2.7
Increased AST | 40 | 4.8 | 60 | 2.1
Increased amylase | 39 | 12 | 33 | 7
Hyponatremia | 39 | 10 | 36 | 7
Increased alkaline phosphatase | 29 | 2.0 | 32 | 1.0
Hyperkalemia | 29 | 2.4 | 28 | 2.9
Hypocalcemia | 21 | 0.4 | 35 | 0.6
Hypomagnesemia | 16 | 0.4 | 26 | 1.6
Hematology
Anemia | 43 | 3.0 | 64 | 9
Lymphopenia | 36 | 5 | 63 | 14
a Each test incidence is based on the number of patients who had both baseline and at least one on-study laboratory measurement available: nivolumab and YERVOY group (range: 490 to 538 patients) and sunitinib group (range: 485 to 523 patients).

In addition, among patients with TSH ≤ ULN at baseline, a lower proportion of patients experienced a treatment-emergent elevation of TSH > ULN in the YERVOY with nivolumab group compared to the sunitinib group (31% and 61%, respectively).

MSI-H or dMMR Metastatic Colorectal Cancer

Treatment of MSI -H or dMMR mCRC: In Combination with Nivolumab

The safety of YERVOY in combination with nivolumab was evaluated in CHECKMATE-8HW, a randomized, open-label, three arm trial in immunotherapy naïve patients with MSI-H or dMMR mCRC [see Clinical Studies (14.4)]. Patients received one of the following:

- YERVOY 1 mg/kg every 3 weeks and nivolumab 240 mg every 3 weeks for a maximum of 4 doses, then nivolumab 480 mg every 4 weeks.
- Nivolumab 240 mg every 2 weeks for 6 doses, then nivolumab 480 mg every 4 weeks.
- Investigator’s choice chemotherapy: mFOLFOX or FOLFIRI [see Clinical Studies (14.4)].

In the YERVOY and nivolumab arm, the median duration of exposure to YERVOY was 2.1 months (range 1 day to 3.7 months); patients received a median of 4 doses (range 1-4). The median duration of treatment in the YERVOY and nivolumab arm was 20.5 months (range: 1 day to 35.9 months); 70% were exposed to treatment for >6 months, and 63% were exposed for >1 year. The median duration of treatment was 16.4 months (range: 1 day to 36 months) in the nivolumab-only arm; 64% were exposed to treatment for >6 months, and 54% were exposed for >1 year.

Serious adverse reactions occurred in 46% of patients receiving YERVOY in combination with nivolumab, and 39% of patients receiving nivolumab alone. The most frequent serious adverse reactions reported in ≥1% of patients who received YERVOY with nivolumab were adrenal insufficiency (2.8%), hypophysitis (2.8%), diarrhea (2.0%), abdominal pain (2.0%), small intestinal obstruction (2.0%), pneumonia (1.7%), acute kidney injury (1.4%), immune-mediated enterocolitis (1.4%), pneumonitis (1.4%), colitis (1.1%), large intestinal obstruction (1.1%), and urinary tract infection (1.1%). The most frequent serious adverse reactions reported in >1% of patients who received OPDIVO, as a single agent, were intestinal obstruction (2.3%), acute kidney injury (1.7%), COVID-19 (1.7%), abdominal pain (1.4%), diarrhea (1.4%), ileus (1.4%), subileus (1.4%), pulmonary embolism (1.4%), adrenal insufficiency (1.1%) and pneumonia (1.1%).

Fatal adverse reactions occurred in 2 (0.6%) patients who received YERVOY in combination with nivolumab; these included myocarditis, and pneumonitis (1 each).

YERVOY and/or nivolumab were permanently discontinued in 19% of patients receiving the combination. The most frequent adverse reactions (>1%) leading to permanent discontinuation were adrenal insufficiency (1.4%), immune-mediated enterocolitis (1.1%), and pneumonitis (1.1%). Nivolumab was permanently discontinued in 13% of patients receiving single agent nivolumab. Adverse reactions leading to the delay of YERVOY and/or nivolumab occurred in 48% of patients receiving the combination; single agent nivolumab was delayed in 37% of patients due to adverse reactions.

The most common adverse reactions reported in ≥20% of patients treated with YERVOY in combination with nivolumab were fatigue, diarrhea, pruritus, abdominal pain, musculoskeletal pain, and nausea. The most common adverse reactions reported in ≥20% of patients treated with nivolumab as a single agent, were fatigue, diarrhea, abdominal pain, pruritus, and musculoskeletal pain.

Tables 10 and 11 summarize the adverse reactions and selected laboratory abnormalities, for YERVOY in combination with nivolumab and nivolumab arms respectively, in CHECKMATE-8HW.

Table 10: Adverse Reactions in ≥10% in Patient and a Difference Between Arms of >5% for All Grades in - CHECKMATE-8HW
Adverse Reaction | YERVOY and Nivolumab (n=352) |  | Nivolumab (n=351)
Adverse Reaction | All Grades (%) | Grades 3 or 4 (%) | All Grades (%) | Grades 3 or 4 (%)
Gastrointestinal
Diarrheaa | 35 | 4.5 | 30 | 3.4
Skin and Subcutaneous Tissue
Pruritus | 30 | 0 | 23 | 0
Musculoskeletal and Connective Tissue
Arthralgia | 20 | 0.6 | 15 | 0.6
Endocrine
Hypothyroidism | 18 | 0.6 | 10 | 0
Hyperthyroidism | 12 | 0 | 5 | 0
Toxicity was graded per NCI CTCAE v5.
a Includes colitis, diarrhea, enterocolitis, immune-mediated enterocolitis

Table 11: Laboratory Values Worsening from Baselinea in ≥10% of Patients and a Difference Between Arms of >5% for All Grades - CHECKMATE-8HW
Laboratory Abnormalitya | YERVOY and Nivolumab (n=352) |  | Nivolumab (n=351)
Laboratory Abnormalitya | All Grades (%) | Grades 3-or 4 (%) | All Grades (%) | Grades 3 or -4 (%)
Hematology
Lymphocytes decreased | 30 | 5 | 37 | 4
Neutrophils decreased | 21 | 1.7 | 12 | 0.6
Chemistry
Lipase increased | 44 | 10 | 32 | 11
Amylase increased | 41 | 4.6 | 33 | 5
ALT increased | 39 | 3.5 | 32 | 1.4
AST increased | 38 | 3.2 | 29 | 1.4
Sodium decreased | 36 | 3.2 | 30 | 2.3
Creatinine increased | 32 | 2 | 25 | 1.4
Potassium increased | 29 | 1.2 | 35 | 0.9
Glucose decreased | 17 | 0 | 12 | 0
a Each test incidence is based on the number of patients who had both baseline and at least one on-study laboratory measurement available: YERVOY and nivolumab group (range: 108 to 343 patients) or nivolumab group (range: 102 to 348 patients).

Hepatocellular Carcinoma: In Combination with Nivolumab

Unresectable or Metastatic Hepatocellular Carcinoma (HCC)

The safety of YERVOY in combination with nivolumab was evaluated in CHECKMATE-9DW, a randomized, open-label trial in adult patients with unresectable or metastatic HCC [see Clinical Studies (14.5)]. Patients received YERVOY in combination with nivolumab (n=332) or investigator’s choice of lenvatinib (n=275) or sorafenib (n=50) at the following dosage:

- YERVOY 3 mg/kg administered intravenously over 30 minutes in combination with nivolumab 1 mg/kg administered intravenously over 30 minutes every 3 weeks, for a maximum of 4 doses, followed by single agent nivolumab at 480 mg administered intravenously over 30 minutes every 4 weeks, or
- Investigator’s choice:
  - Lenvatinib 8 mg orally daily (if body weight <60 kg) or 12 mg orally daily (if body weight ≥60 kg), or
  - Sorafenib 400 mg orally twice daily

In the YERVOY and nivolumab arm, the median duration of exposure to nivolumab was 4.7 months (range: <0.1 to 24.4 months), 45% were exposed for >6 months and 30% were exposed for >1 year.

Serious adverse reactions occurred in 53% of patients treated with YERVOY in combination with nivolumab. The most frequent non-liver-related serious adverse reactions reported in ≥2% were diarrhea/colitis (4.5%), gastrointestinal hemorrhage (3%), and rash (2.4%).

Liver-related serious adverse reactions occurred in 17% of patients treated with YERVOY in combination with nivolumab, including Grade 3-4 events in 16% of patients. The most frequently reported all grade liver-related serious adverse reactions occurring in ≥1% of patients were immune-mediated hepatitis (3%), increased AST/ALT (3%), hepatic failure (2.4%), ascites (2.4%), and hepatotoxicity (1.2%).

Fatal adverse reactions occurred in 12 (3.6%) patients who received YERVOY in combination with nivolumab; these included 4 (1.2%) patients who died due to immune-mediated or autoimmune hepatitis and 4 (1.2%) patients who died of hepatic failure.

Permanent discontinuation due to an adverse reaction occurred in 27% of patients treated with YERVOY in combination with nivolumab. Adverse reactions leading to permanent discontinuation in >1% of patients included immune-mediated hepatitis (1.8%), diarrhea/colitis (1.8%), and hepatic failure (1.2%).

Dosage interruptions due to an adverse reaction occurred in 62% of patients treated with YERVOY in combination with nivolumab. Adverse reactions which required dosage interruption in >5% of patients included increased AST (13%), increased ALT (11%), and diarrhea/colitis (8%).

The most common (>20%) adverse reactions were rash, pruritus, fatigue, and diarrhea.

Tables 12 and 13 summarize the adverse reactions and laboratory abnormalities, respectively, in CHECKMATE-9DW.

Table 12: Adverse Reactions Occurring in ≥10% of YERVOY in combination with Nivolumab-Treated Patients - CHECKMATE-9DW
Adverse Reaction | YERVOY and Nivolumab (n=332) |  | Lenvatinib or Sorafenib (n=325)
Adverse Reaction | All Grades (%) | Grades 3-4 (%) | All Grades (%) | Grades 3-4 (%)
Skin and Subcutaneous Tissue
Rasha | 36 | 3.6 | 15 | 1.2
Pruritus | 34 | 1.5 | 7 | 0.3
General
Fatiguea | 33 | 2.4 | 39 | 4
Pyrexiaa | 15 | 0.6 | 9 | 1.5
Edemaa | 13 | 1.2 | 13 | 1.5
Gastrointestinal
Diarrhea | 25 | 6 | 39 | 3.4
Abdominal paina | 14 | 1.2 | 27 | 2.5
Nausea | 10 | 0.3 | 16 | 0.9
Musculoskeletal and Connective Tissue
Musculoskeletal paina | 17 | 0.6 | 23 | 0.3
Arthralgia | 12 | 0.3 | 13 | 0.6
Metabolism and Nutrition
Decreased appetite | 16 | 1.2 | 28 | 1.8
Endocrine
Hypothyroidisma | 14 | 0 | 27 | 0
Hyperthyroidism | 11 | 0.6 | 1.5 | 0
Respiratory, Thoracic and Mediastinal
Cougha | 13 | 0 | 8 | 0
Toxicity was graded per NCI CTCAE v5
a Represents a composite of multiple related terms.

Clinically important adverse reactions reported in <10% of patients who received YERVOY with nivolumab were hyperglycemia (8%), adrenal insufficiency (4.2%), pneumonitis (2.7%), and pancreatitis (2.4%).

Table 13: Laboratory Values Worsening from Baselinea Occurring in ≥20% of YERVOY in combination with Nivolumab-Treated Patients - CHECKMATE-9DW
Laboratory Abnormality | YERVOY and Nivolumab; (n=332) |  | Lenvatinib or Sorafenib; (n=325)
Laboratory Abnormality | Grades 1-4 (%) | Grades 3-4 (%) |  | Grades 1-4 (%) | Grades 3-4 (%)
Chemistry
Increased AST | 62 | 29 |  | 51 | 14
Increased ALT | 61 | 17 |  | 46 | 9
Increased lipase | 58 | 16 |  | 39 | 5
Decreased albumin | 48 | 0.9 |  | 57 | 0.6
Hyponatremia | 45 | 6 |  | 42 | 3.8
Hyperglycemia | 44 | 15 |  | 32 | 2.1
Increased bilirubin | 44 | 10 |  | 44 | 8
Increased amylase | 41 | 6 |  | 26 | 1
Increased alkaline phosphatase | 36 | 1.2 |  | 38 | 5
Hypocalcemia | 29 | 0.9 |  | 46 | 0
Increased creatinine | 26 | 2.4 |  | 23 | 0.6
Hypokalemia | 21 | 2.1 |  | 20 | 2.6
Hematology
Anemia | 44 | 5 |  | 40 | 3.8
Lymphopenia | 40 | 6.1 |  | 40 | 8
Thrombocytopenia | 27 | 4 |  | 44 | 4.8
Neutropenia | 24 | 4 |  | 32 | 3.5
a Each test incidence is based on the number of patients who had both baseline and at least one on-study laboratory measurement available: YERVOY and nivolumab group (range: 168 to 331 patients) and lenvatinib or sorafenib group (range: 145 to 315 patients).

Previously Treated Hepatocellular Carcinoma

The safety of YERVOY 3 mg/kg in combination with nivolumab 1 mg/kg was evaluated in a subgroup of 49 patients with HCC and Child-Pugh Class A cirrhosis who progressed on or were intolerant to sorafenib enrolled in Cohort 4 of CHECKMATE-040. YERVOY and nivolumab were administered every 3 weeks for four doses, followed by single-agent nivolumab 240 mg every 2 weeks until disease progression or unacceptable toxicity.

During the YERVOY and nivolumab combination period, 33 of 49 (67%) patients received all four planned doses of YERVOY and nivolumab. During the entire treatment period, the median duration of exposure to YERVOY was 2.1 months (range: 0 to 4.5 months) and to nivolumab was 5.1 months (range: 0 to 35+ months). Forty-seven percent of patients were exposed to treatment for >6 months, and 35% of patients were exposed to treatment for >1 year. Serious adverse reactions occurred in 59% of patients. Treatment was discontinued in 29% of patients and delayed in 65% of patients for an adverse reaction.

Serious adverse reactions reported in ≥4% of patients were pyrexia, diarrhea, anemia, increased AST, adrenal insufficiency, ascites, esophageal varices hemorrhage, hyponatremia, increased blood bilirubin, and pneumonitis.

Table 14 summarizes the adverse reactions and Table 15 summarizes the laboratory abnormalities of YERVOY in combination with nivolumab in CHECKMATE-040.

Table 14: Adverse Reactions Occurring in ≥10% of Patients Receiving YERVOY in Combination with Nivolumab in Cohort 4 of CHECKMATE-040
Adverse Reaction | YERVOY and Nivolumab; (n=49)
 | All Grades (%) | Grades 3-4 (%)
Skin and Subcutaneous Tissue
Rash | 53 | 8
Pruritus | 53 | 4
Musculoskeletal and Connective Tissue
Musculoskeletal pain | 41 | 2
Arthralgia | 10 | 0
Gastrointestinal
Diarrhea | 39 | 4
Abdominal pain | 22 | 6
Nausea | 20 | 0
Ascites | 14 | 6
Constipation | 14 | 0
Dry mouth | 12 | 0
Dyspepsia | 12 | 2
Vomiting | 12 | 2
Stomatitis | 10 | 0
Respiratory, Thoracic and Mediastinal
Cough | 37 | 0
Dyspnea | 14 | 0
Pneumonitis | 10 | 2
Metabolism and Nutrition
Decreased appetite | 35 | 2
General
Fatigue | 27 | 2
Pyrexia | 27 | 0
Malaise | 18 | 2
Edema | 16 | 2
Influenza-like illness | 14 | 0
Chills | 10 | 0
Nervous System
Headache | 22 | 0
Dizziness | 20 | 0
Endocrine
Hypothyroidism | 20 | 0
Adrenal insufficiency | 18 | 4
Investigations
Weight decreased | 20 | 0
Psychiatric
Insomnia | 18 | 0
Blood and Lymphatic System
Anemia | 10 | 4
Infections
Influenza | 10 | 2
Vascular
Hypotension | 10 | 0

Clinically important adverse reactions reported in <10% of patients receiving YERVOY with nivolumab were hyperglycemia (8%), colitis (4%), and increased blood creatine phosphokinase (2%).

Table 15: Select Laboratory Abnormalities (≥10%) Worsening from Baseline in Patients Receiving YERVOY in Combination with Nivolumab in Cohort 4 of CHECKMATE-040
Laboratory Abnormality | YERVOY and Nivolumab; (n=47)
 | All Grades (%) | Grades 3-4 (%)
Hematology
Lymphopenia | 53 | 13
Anemia | 43 | 4.3
Neutropenia | 43 | 9
Leukopenia | 40 | 2.1
Thrombocytopenia | 34 | 4.3
Chemistry
Increased AST | 66 | 40
Increased ALT | 66 | 21
Increased bilirubin | 55 | 11
Increased lipase | 51 | 26
Hyponatremia | 49 | 32
Hypocalcemia | 47 | 0
Increased alkaline phosphatase | 40 | 4.3
Increased amylase | 38 | 15
Hypokalemia | 26 | 2.1
Hyperkalemia | 23 | 4.3
Increased creatinine | 21 | 0
Hypomagnesemia | 11 | 0

In patients who received YERVOY with nivolumab, virologic breakthrough occurred in 4 of 28 (14%) patients and 2 of 4 (50%) patients with active HBV or HCV at baseline, respectively. HBV virologic breakthrough was defined as at least a 1 log increase in HBV DNA for those patients with detectable HBV DNA at baseline. HCV virologic breakthrough was defined as a 1 log increase in HCV RNA from baseline.

First-line Treatment of Metastatic NSCLC: In Combination with Nivolumab

The safety of YERVOY in combination with nivolumab was evaluated in CHECKMATE-227, a randomized, multicenter, multi-cohort, open-label trial in patients with previously untreated metastatic or recurrent NSCLC with no EGFR or ALK genomic tumor aberrations [see Clinical Studies (14.6)]. The trial excluded patients with untreated brain metastases, carcinomatous meningitis, active autoimmune disease, or medical conditions requiring systemic immunosuppression. Patients received YERVOY 1 mg/kg by intravenous infusion over 30 minutes every 6 weeks and nivolumab 3 mg/kg by intravenous infusion over 30 minutes every 2 weeks or platinum-doublet chemotherapy every 3 weeks for 4 cycles. The median duration of therapy in YERVOY and nivolumab-treated patients was 4.2 months (range: 1 day to 25.5 months): 39% of patients received YERVOY and nivolumab for >6 months and 23% of patients received YERVOY and nivolumab for >1 year. The population characteristics were: median age 64 years (range: 26 to 87); 48% were ≥65 years of age, 76% White, and 67% male. Baseline ECOG performance status was 0 (35%) or 1 (65%), 85% were former/current smokers, 11% had brain metastases, 28% had squamous histology and 72% had non-squamous histology.

Serious adverse reactions occurred in 58% of patients. YERVOY and nivolumab were discontinued for adverse reactions in 24% of patients and 53% had at least one dose withheld for an adverse reaction.

The most frequent (≥2%) serious adverse reactions were pneumonia, diarrhea/colitis, pneumonitis, hepatitis, pulmonary embolism, adrenal insufficiency, and hypophysitis. Fatal adverse reactions occurred in 1.7% of patients; these included events of pneumonitis (4 patients), myocarditis, acute kidney injury, shock, hyperglycemia, multi-system organ failure, and renal failure. The most common (≥20%) adverse reactions were fatigue, rash, decreased appetite, musculoskeletal pain, diarrhea/colitis, dyspnea, cough, hepatitis, nausea, and pruritus.

Tables 16 and 17 summarize selected adverse reactions and laboratory abnormalities, respectively, in CHECKMATE-227.

Table 16: Adverse Reactions in ≥10% of Patients Receiving YERVOY and Nivolumab - CHECKMATE-227
Adverse Reaction | YERVOY and Nivolumab (n=576) |  | Platinum-Doublet Chemotherapy (n=570)
Adverse Reaction | All Grades (%) | Grades 3-4 (%) | All Grades (%) | Grades 3-4 (%)
General
Fatiguea | 44 | 6 | 42 | 4.4
Pyrexia | 18 | 0.5 | 11 | 0.4
Edemab | 14 | 0.2 | 12 | 0.5
Skin and Subcutaneous Tissue
Rashc | 34 | 4.7 | 10 | 0.4
Pruritusd | 21 | 0.5 | 3.3 | 0
Metabolism and Nutrition
Decreased appetite | 31 | 2.3 | 26 | 1.4
Musculoskeletal and Connective Tissue
Musculoskeletal paine | 27 | 1.9 | 16 | 0.7
Arthralgia | 13 | 0.9 | 2.5 | 0.2
Gastrointestinal
Diarrhea/colitisf | 26 | 3.6 | 16 | 0.9
Nausea | 21 | 1.0 | 42 | 2.5
Constipation | 18 | 0.3 | 27 | 0.5
Vomiting | 13 | 1.0 | 18 | 2.3
Abdominal paing | 10 | 0.2 | 9 | 0.7
Respiratory, Thoracic, and Mediastinal
Dyspneah | 26 | 4.3 | 16 | 2.1
Coughi | 23 | 0.2 | 13 | 0
Hepatobiliary
Hepatitisj | 21 | 9 | 10 | 1.2
Endocrine
Hypothyroidismk | 16 | 0.5 | 1.2 | 0
Hyperthyroidisml | 10 | 0 | 0.5 | 0
Infections and Infestations
Pneumoniam | 13 | 7 | 8 | 4.0
Nervous System
Headache | 11 | 0.5 | 6 | 0
a Includes fatigue and asthenia.
b Includes eyelid edema, face edema, generalized edema, localized edema, edema, edema peripheral, and periorbital edema.
c Includes autoimmune dermatitis, dermatitis, dermatitis acneiform, dermatitis allergic, dermatitis atopic, dermatitis bullous, dermatitis contact, dermatitis exfoliative, dermatitis psoriasiform, granulomatous dermatitis, rash generalized, drug eruption, dyshidrotic eczema, eczema, exfoliative rash, nodular rash, rash, rash erythematous, rash generalized, rash macular, rash maculo-papular, rash papular, rash pruritic, rash pustular, toxic skin eruption.
d Includes pruritus and pruritus generalized.
e Includes back pain, bone pain, musculoskeletal chest pain, musculoskeletal discomfort, musculoskeletal pain, myalgia, and pain in extremity.
f Includes colitis, colitis microscopic, colitis ulcerative, diarrhea, enteritis infectious, enterocolitis, enterocolitis infectious, and enterocolitis viral.
g Includes abdominal discomfort, abdominal pain, abdominal pain lower, abdominal pain upper, and abdominal tenderness.
h Includes dyspnea and dyspnea exertional.
i Includes cough and productive cough.
j Includes alanine aminotransferase increased, aspartate aminotransferase increased, autoimmune hepatitis, blood bilirubin increased, hepatic enzyme increased, hepatic failure, hepatic function abnormal, hepatitis, hepatitis E, hepatocellular injury, hepatotoxicity, hyperbilirubinemia, immune-mediated hepatitis, liver function test abnormal, liver function test increased, transaminases increased.
k Includes autoimmune thyroiditis, blood thyroid stimulating hormone increased, hypothyroidism, primary hypothyroidism, thyroiditis, and tri-iodothyronine free decreased.
l Contains blood thyroid stimulating hormone decreased, hyperthyroidism, and tri-iodothyronine free increased.
m Includes lower respiratory tract infection, lower respiratory tract infection bacterial, lung infection, pneumonia, pneumonia adenoviral, pneumonia aspiration, pneumonia bacterial, pneumonia klebsiella, pneumonia influenzal, pneumonia viral, atypical pneumonia, organizing pneumonia.

Other clinically important adverse reactions in CHECKMATE-227 were:

Skin and Subcutaneous Tissue: urticaria, alopecia, erythema multiforme, vitiligo

Gastrointestinal: stomatitis, pancreatitis, gastritis

Musculoskeletal and Connective Tissue: arthritis, polymyalgia rheumatica, rhabdomyolysis

Nervous System: peripheral neuropathy, autoimmune encephalitis

Blood and Lymphatic System: eosinophilia

Eye Disorders: blurred vision, uveitis

Cardiac: atrial fibrillation, myocarditis

Table 17: Laboratory Values Worsening from Baselinea Occurring in ≥20% of Patients on YERVOY and Nivolumab - CHECKMATE-227
Laboratory Abnormality | YERVOY and Nivolumab |  | Platinum-doublet Chemotherapy
Laboratory Abnormality | Grades 1-4 (%) | Grades 3-4 (%) | Grades 1-4 (%) | Grades 3-4 (%)
Hematology
Anemia | 46 | 3.6 | 78 | 14
Lymphopenia | 46 | 5 | 60 | 15
Chemistry
Hyponatremia | 41 | 12 | 26 | 4.9
Increased AST | 39 | 5 | 26 | 0.4
Increased ALT | 36 | 7 | 27 | 0.7
Increased lipase | 35 | 14 | 14 | 3.4
Increased alkaline phosphatase | 34 | 3.8 | 20 | 0.2
Increased amylase | 28 | 9 | 18 | 1.9
Hypocalcemia | 28 | 1.7 | 17 | 1.3
Hyperkalemia | 27 | 3.4 | 22 | 0.4
Increased creatinine | 22 | 0.9 | 17 | 0.2
a Each test incidence is based on the number of patients who had both baseline and at least one on-study laboratory measurement available: YERVOY and nivolumab group (range: 494 to 556 patients) and chemotherapy group (range: 469 to 542 patients).

First-line Treatment of Metastatic or Recurrent NSCLC: In Combination with Nivolumab and Platinum-Doublet Chemotherapy

The safety of YERVOY in combination with nivolumab and platinum-doublet chemotherapy was evaluated in CHECKMATE-9LA [see Clinical Studies (14.6)]. Patients received either YERVOY 1 mg/kg administered every 6 weeks in combination with nivolumab 360 mg administered every 3 weeks and platinum-doublet chemotherapy administered every 3 weeks for 2 cycles; or platinum-doublet chemotherapy administered every 3 weeks for 4 cycles. The median duration of therapy in YERVOY in combination with nivolumab and platinum-doublet chemotherapy was 6 months (range: 1 day to 19 months): 50% of patients received YERVOY and nivolumab for >6 months and 13% of patients received YERVOY and nivolumab for >1 year.

Serious adverse reactions occurred in 57% of patients who were treated with YERVOY in combination with nivolumab and platinum-doublet chemotherapy. The most frequent (>2%) serious adverse reactions were pneumonia, diarrhea, febrile neutropenia, anemia, acute kidney injury, musculoskeletal pain, dyspnea, pneumonitis, and respiratory failure. Fatal adverse reactions occurred in 7 (2%) patients, and included hepatic toxicity, acute renal failure, sepsis, pneumonitis, diarrhea with hypokalemia, and massive hemoptysis in the setting of thrombocytopenia.

Study therapy with YERVOY in combination with nivolumab and platinum-doublet chemotherapy was permanently discontinued for adverse reactions in 24% of patients and 56% had at least one treatment withheld for an adverse reaction. The most common (>20%) adverse reactions were fatigue, musculoskeletal pain, nausea, diarrhea, rash, decreased appetite, constipation, and pruritus.

Tables 18 and 19 summarize selected adverse reactions and laboratory abnormalities, respectively, in CHECKMATE-9LA.

Table 18: Adverse Reactions in >10% of Patients Receiving YERVOY and Nivolumab and Platinum-Doublet Chemotherapy - CHECKMATE-9LA
Adverse Reaction | YERVOY and Nivolumab and Platinum-Doublet Chemotherapy (n=358) |  | Platinum-Doublet Chemotherapy (n=349)
Adverse Reaction | All Grades (%) | Grades 3-4 (%) | All Grades (%) | Grades 3-4 (%)
General
Fatiguea | 49 | 5 | 40 | 4.9
Pyrexia | 14 | 0.6 | 10 | 0.6
Musculoskeletal and Connective Tissue
Musculoskeletal painb | 39 | 4.5 | 27 | 2.0
Gastrointestinal
Nausea | 32 | 1.7 | 41 | 0.9
Diarrheac | 31 | 6 | 18 | 1.7
Constipation | 21 | 0.6 | 23 | 0.6
Vomiting | 18 | 2.0 | 17 | 1.4
Abdominal paind | 12 | 0.6 | 11 | 0.9
Skin and Subcutaneous Tissue
Rashe | 30 | 4.7 | 10 | 0.3
Pruritusf | 21 | 0.8 | 2.9 | 0
Alopecia | 11 | 0.8 | 10 | 0.6
Metabolism and Nutrition
Decreased appetite | 28 | 2.0 | 22 | 1.7
Respiratory, Thoracic and Mediastinal
Coughg | 19 | 0.6 | 15 | 0.9
Dyspneah | 18 | 4.7 | 14 | 3.2
Endocrine
Hypothyroidismi | 19 | 0.3 | 3.4 | 0
Nervous System
Headache | 11 | 0.6 | 7 | 0
Dizzinessj | 11 | 0.6 | 6 | 0
Toxicity was graded per NCI CTCAE v4.
a Includes fatigue and asthenia.
b Includes myalgia, back pain, pain in extremity, musculoskeletal pain, bone pain, flank pain, muscle spasms, musculoskeletal chest pain, musculoskeletal disorder, osteitis, musculoskeletal stiffness, non-cardiac chest pain, arthralgia, arthritis, arthropathy, joint effusion, psoriatic arthropathy, synovitis.
c Includes colitis, ulcerative colitis, diarrhea, and enterocolitis.
d Includes abdominal discomfort, abdominal pain, lower abdominal pain, upper abdominal pain, and gastrointestinal pain.
e Includes acne, dermatitis, acneiform dermatitis, allergic dermatitis, atopic dermatitis, bullous dermatitis, generalized exfoliative dermatitis, eczema, keratoderma blennorrhagica, palmar-plantar erythrodysesthesia syndrome, rash, erythematous rash, generalized rash, macular rash, maculo-papular rash, morbilliform rash, papular rash, pruritic rash, skin exfoliation, skin reaction, skin toxicity, Stevens-Johnson syndrome, urticaria.
f Includes pruritus and generalized pruritus.
g Includes cough, productive cough, and upper-airway cough syndrome.
h Includes dyspnea, dyspnea at rest, and exertional dyspnea.
i Includes autoimmune thyroiditis, increased blood thyroid stimulating hormone, hypothyroidism, thyroiditis, and decreased free tri-iodothyronine.
j Includes dizziness, vertigo and positional vertigo

Table 19: Laboratory Values Worsening from Baselinea Occurring in >20% of Patients on YERVOY and Nivolumab and Platinum-Doublet Chemotherapy - CHECKMATE-9LA
Laboratory Abnormality | YERVOY and Nivolumab and Platinum-Doublet Chemotherapy |  | Platinum-Doublet Chemotherapy
Laboratory Abnormality | Grades 1-4 (%) | Grades 3-4 (%) | Grades 1-4 (%) | Grades 3-4 (%)
Hematology
Anemia | 70 | 9 | 74 | 16
Lymphopenia | 41 | 6 | 40 | 11
Neutropenia | 40 | 15 | 42 | 15
Leukopenia | 36 | 10 | 40 | 9
Thrombocytopenia | 23 | 4.3 | 24 | 5
Chemistry
Hyperglycemia | 45 | 7 | 42 | 2.6
Hyponatremia | 37 | 10 | 27 | 7
Increased ALT | 34 | 4.3 | 24 | 1.2
Increased lipase | 31 | 12 | 10 | 2.2
Increased alkaline phosphatase | 31 | 1.2 | 26 | 0.3
Increased amylase | 30 | 7 | 19 | 1.3
Increased AST | 30 | 3.5 | 22 | 0.3
Hypomagnesemia | 29 | 1.2 | 33 | 0.6
Hypocalcemia | 26 | 1.4 | 22 | 1.8
Increased creatinine | 26 | 1.2 | 23 | 0.6
Hyperkalemia | 22 | 1.7 | 21 | 2.1
a Each test incidence is based on the number of patients who had both baseline and at least one on-study laboratory measurement available: YERVOY and nivolumab and platinum-doublet chemotherapy group (range: 197 to 347 patients) and platinum-doublet chemotherapy group (range: 191 to 335 patients).

First-line Treatment of Unresectable Malignant Pleural Mesothelioma: In Combination with Nivolumab

The safety of YERVOY in combination with nivolumab was evaluated in CHECKMATE-743, a randomized, open-label trial in patients with previously untreated unresectable malignant pleural mesothelioma [see Clinical Studies (14.7)]. Patients received either YERVOY 1 mg/kg over 30 minutes by intravenous infusion every 6 weeks and nivolumab 3 mg/kg over 30 minutes by intravenous infusion every 2 weeks for up to 2 years; or platinum-doublet chemotherapy for up to 6 cycles. The median duration of therapy in YERVOY and nivolumab-treated patients was 5.6 months (range: 0 to 26.2 months); 48% of patients received YERVOY and nivolumab for >6 months and 24% of patients received YERVOY and nivolumab for >1 year.

Serious adverse reactions occurred in 54% of patients who were treated with YERVOY in combination with nivolumab. The most frequent (≥2%) serious adverse reactions were pneumonia, pyrexia, diarrhea, pneumonitis, pleural effusion, dyspnea, acute kidney injury, infusion-related reaction, musculoskeletal pain, and pulmonary embolism. Fatal adverse reactions occurred in 4 (1.3%) patients and included pneumonitis, acute heart failure, sepsis, and encephalitis.

Both YERVOY and nivolumab were permanently discontinued due to adverse reactions in 23% of patients and 52% had at least one dose withheld due to an adverse reaction. An additional 4.7% of patients permanently discontinued YERVOY alone due to adverse reactions.

The most common (≥20%) adverse reactions were fatigue, musculoskeletal pain, rash, diarrhea, dyspnea, nausea, decreased appetite, cough, and pruritus.

Tables 20 and 21 summarize adverse reactions and laboratory abnormalities, respectively, in CHECKMATE-743.

Table 20: Adverse Reactions in ≥10% of Patients Receiving YERVOY and Nivolumab - CHECKMATE-743
Adverse Reaction | YERVOY and Nivolumab (n=300) |  | Chemotherapy (n=284)
Adverse Reaction | All Grades (%) | Grades 3-4 (%) | All Grades (%) | Grades 3-4 (%)
General
Fatiguea | 43 | 4.3 | 45 | 6
Pyrexiab | 18 | 1.3 | 4.6 | 0.7
Edemac | 17 | 0 | 8 | 0
Musculoskeletal and Connective Tissue
Musculoskeletal paind | 38 | 3.3 | 17 | 1.1
Arthralgia | 13 | 1.0 | 1.1 | 0
Skin and Subcutaneous Tissue
Rashe | 34 | 2.7 | 11 | 0.4
Pruritusf | 21 | 1.0 | 1.4 | 0
Gastrointestinal
Diarrheag | 32 | 6 | 12 | 1.1
Nausea | 24 | 0.7 | 43 | 2.5
Constipation | 19 | 0.3 | 30 | 0.7
Abdominal painh | 15 | 1 | 10 | 0.7
Vomiting | 14 | 0 | 18 | 2.1
Respiratory, Thoracic, and Mediastinal
Dyspneai | 27 | 2.3 | 16 | 3.2
Coughj | 23 | 0.7 | 9 | 0
Metabolism and Nutrition
Decreased appetite | 24 | 1.0 | 25 | 1.4
Endocrine
Hypothyroidismk | 15 | 0 | 1.4 | 0
Infections and Infestations
Upper respiratory tract infectionl | 12 | 0.3 | 7 | 0
Pneumoniam | 10 | 4.0 | 4.2 | 2.1
a Includes fatigue and asthenia.
b Includes pyrexia and tumor-associated fever.
c Includes edema, generalized edema, peripheral edema, and peripheral swelling.
d Includes musculoskeletal pain, back pain, bone pain, flank pain, involuntary muscle contractions, muscle spasms, muscle twitching, musculoskeletal chest pain, musculoskeletal stiffness, myalgia, neck pain, non-cardiac chest pain, pain in extremity, polymyalgia rheumatica, and spinal pain.
e Includes rash, acne, acneiform dermatitis, allergic dermatitis, atopic dermatitis, autoimmune dermatitis, bullous dermatitis, contact dermatitis, dermatitis, drug eruption, dyshidrotic eczema, eczema, erythematous rash, exfoliative rash, generalized exfoliative dermatitis, generalized rash, granulomatous dermatitis, keratoderma blennorrhagica, macular rash, maculopapular rash, morbilliform rash, nodular rash, papular rash, psoriasiform dermatitis, pruritic rash, pustular rash, skin exfoliation, skin reaction, skin toxicity, Stevens-Johnson syndrome, toxic skin eruption, and urticaria.
f Includes pruritus, allergic pruritus, and generalized pruritus.
g Includes diarrhea, colitis, enteritis, infectious enteritis, enterocolitis, infectious enterocolitis, microscopic colitis, ulcerative colitis, and viral enterocolitis.
h Includes abdominal pain, abdominal discomfort, abdominal tenderness, gastrointestinal pain, lower abdominal pain, and upper abdominal pain.
i Includes dyspnea, dyspnea at rest, and exertional dyspnea.
j Includes cough, productive cough, and upper-airway cough syndrome.
k Includes hypothyroidism, autoimmune thyroiditis, decreased free tri-iodothyronine, increased blood thyroid stimulating hormone, primary hypothyroidism, thyroiditis, and autoimmune hypothyroidism.
l Includes upper respiratory tract infection, nasopharyngitis, pharyngitis, and rhinitis.
m Includes pneumonia, lower respiratory tract infection, lung infection, aspiration pneumonia, and Pneumocystis jirovecii pneumonia.

Table 21: Laboratory Values Worsening from Baselinea Occurring in ≥20% of Patients on YERVOY and Nivolumab - CHECKMATE-743
Laboratory Abnormality | YERVOY and Nivolumab |  | Chemotherapy
Laboratory Abnormality | Grades 1-4 (%) | Grades 3-4 (%) | Grades 1-4 (%) | Grades 3-4 (%)
Chemistry
Hyperglycemia | 53 | 3.7 | 34 | 1.1
Increased AST | 38 | 7 | 17 | 0
Increased ALT | 37 | 7 | 15 | 0.4
Increased lipase | 34 | 13 | 9 | 0.8
Hyponatremia | 32 | 8 | 21 | 2.9
Increased alkaline phosphatase | 31 | 3.1 | 12 | 0
Hyperkalemia | 30 | 4.1 | 16 | 0.7
Hypocalcemia | 28 | 0 | 16 | 0
Increased amylase | 26 | 5 | 13 | 0.9
Increased creatinine | 20 | 0.3 | 20 | 0.4
Hematology
Lymphopenia | 43 | 8 | 57 | 14
Anemia | 43 | 2.4 | 75 | 15
a Each test incidence is based on the number of patients who had both baseline and at least one on-study laboratory measurement available: YERVOY and nivolumab group (range: 109 to 297 patients) and chemotherapy group (range: 90 to 276 patients).

First-line Treatment of Unresectable Advanced or Metastatic ESCC: In Combination with Nivolumab

The safety of YERVOY in combination with nivolumab was evaluated in CHECKMATE-648, a randomized, active-controlled, multicenter, open-label trial in patients with previously untreated unresectable advanced, recurrent or metastatic ESCC [see Clinical Studies (14.8)]. Patients received one of the following treatments:

- YERVOY 1 mg/kg every 6 weeks in combination with nivolumab 3 mg/kg every 2 weeks.
- 5-FU (fluorouracil) 800 mg/m^2/day intravenously on days 1 through 5 (for 5 days), and cisplatin 80 mg/m^2 intravenously on day 1 (of a 4-week cycle).

Among patients who received YERVOY and nivolumab, the median duration of exposure was 2.8 months (range: 0 to 24 months).

Serious adverse reactions occurred in 69% of patients receiving YERVOY in combination with nivolumab.

The most frequent serious adverse reactions reported in ≥2% of patients who received YERVOY with nivolumab were pneumonia (10%), pyrexia (4.3%), pneumonitis (4.0%), aspiration pneumonia (3.7%), dysphagia (3.7%), hepatic function abnormal (2.8%), decreased appetite (2.8%), adrenal insufficiency (2.5%), and dehydration (2.5%).

Fatal adverse reactions occurred in 5 (1.6%) patients who received YERVOY in combination with nivolumab; these included pneumonitis, interstitial lung disease, pulmonary embolism, and acute respiratory distress syndrome.

YERVOY and/or nivolumab were discontinued in 23% of patients and delayed in 46% of patients for an adverse reaction.

The most common adverse reactions reported in ≥20% of patients treated with YERVOY in combination with nivolumab were rash, fatigue, pyrexia, nausea, diarrhea, and constipation.

Tables 22 and 23 summarize the adverse reactions and laboratory abnormalities, respectively, in CHECKMATE-648.

Table 22: Adverse Reactions in ≥10% of Patients Receiving YERVOY and Nivolumab - CHECKMATE-648
Adverse Reaction | YERVOY and Nivolumab (n=322) |  | Cisplatin and 5-FU (n=304)
Adverse Reaction | All Grades (%) | Grades 3-4 (%) | All Grades (%) | Grades 3-4 (%)
Skin and Subcutaneous Tissue
Rasha | 31 | 3.1 | 7 | 0
Pruritis | 17 | 0.9 | 3.6 | 0
General
Fatiguec | 28 | 2.5 | 41 | 4.9
Pyrexiab | 23 | 0.9 | 12 | 0.3
Gastrointestinal
Nausea | 22 | 0.6 | 56 | 2.6
Diarrhea | 22 | 1.9 | 20 | 2.0
Constipation | 20 | 0.3 | 43 | 1.0
Vomiting | 15 | 1.6 | 19 | 3.0
Dysphagia | 12 | 5 | 12 | 4.9
Stomatitisd | 11 | 0.6 | 35 | 3.0
Abdominal paine | 10 | 0.9 | 11 | 0.7
Metabolism and Nutrition
Decreased appetite | 17 | 4.0 | 50 | 6
Musculoskeletal and Connective Tissue
Musculoskeletal painf | 14 | 0.6 | 8 | 0.3
Infections and Infestations
Pneumoniag | 14 | 8 | 10 | 2.6
Endocrine
Hypothyroidism | 14 | 0 | 0.3 | 0
Respiratory, Thoracic and Mediastinal
Coughh | 13 | 0.3 | 13 | 0.3
Investigations
Weight decreased | 12 | 1.9 | 11 | 1.0
Toxicity was graded per NCI CTCAE v4.
a Includes dermatitis, dermatitis acneiform, dermatitis allergic, dermatitis bullous, drug eruption, exfoliative rash, rash erythematous, rash follicular, rash macular, rash maculo-papular, rash papular, and rash pruritic.
b Includes tumor associated fever.
c Includes asthenia and malaise.
d Includes aphthous ulcer, mouth ulceration, and mucosal inflammation.
e Includes abdominal discomfort, abdominal pain lower, and abdominal pain upper.
f Includes back pain, bone pain, musculoskeletal chest pain, myalgia, neck pain, pain in extremity, and spinal pain.
g Includes organizing pneumonia, pneumonia bacterial, and pneumonia pseudomonal.
h Includes productive cough.

Table 23: Laboratory Values Worsening from Baselinea Occurring in ≥10% of Patients on YERVOY and Nivolumab - CHECKMATE-648
Laboratory Abnormality | YERVOY and Nivolumab (n=322) |  | Cisplatin and 5-FU (n=304)
Laboratory Abnormality | Grades 1-4 (%) | Grades 3-4 (%) | Grades 1-4 (%) | Grades 3-4 (%)
Hematology
Anemia | 52 | 7 | 66 | 14
Lymphopenia | 50 | 13 | 44 | 8
Neutropenia | 13 | 1.3 | 48 | 13
Thrombocytopenia | 12 | 1.0 | 29 | 2.8
Chemistry
Hyponatremia | 45 | 11 | 40 | 8
Hyperglycemia | 43 | 4.3 | 36 | 0.8
Increased AST | 39 | 6 | 11 | 1.4
Increased ALT | 33 | 6 | 8 | 0.7
Hypocalcemia | 32 | 0 | 23 | 0.7
Increased alkaline phosphatase | 31 | 3.3 | 15 | 0
Hyperkalemia | 23 | 1.6 | 24 | 0.7
Hypokalemia | 19 | 5 | 17 | 6
Hypercalcemia | 15 | 2.0 | 8 | 0
Hypoglycemia | 15 | 1.2 | 7 | 0
Increased creatinine | 15 | 0.7 | 31 | 0.7
Hypomagnesemia | 15 | 0 | 25 | 1.8
a Each test incidence is based on the number of patients who had both baseline and at least one on-study laboratory measurement available: YERVOY and nivolumab group (range: 59 to 307 patients) or Cisplatin and 5-FU group (range: 56 to 283 patients).

6.2 Postmarketing Experience

The following adverse reactions have been identified during post-approval use of YERVOY. Because these reactions are reported voluntarily from a population of uncertain size, it is not always possible to reliably estimate their frequency or establish a causal relationship to drug exposure.

Blood and lymphatic system disorders: hemophagocytic lymphohistiocytosis (HLH)

Immune System: graft-versus-host disease, solid organ transplant rejection

Skin and Subcutaneous Tissue: Drug reaction with eosinophilia and systemic symptoms (DRESS syndrome)

8 USE IN SPECIFIC POPULATIONS

8.1 Pregnancy

Risk Summary

Based on findings from animal studies and its mechanism of action [see Clinical Pharmacology (12.1)], YERVOY can cause fetal harm when administered to a pregnant woman. There is insufficient human data for YERVOY exposure in pregnant women. In animal reproduction studies, administration of ipilimumab to cynomolgus monkeys from the onset of organogenesis through delivery resulted in higher incidences of abortion, stillbirth, premature delivery (with corresponding lower birth weight), and higher incidences of infant mortality in a dose-related manner (see Data). The effects of ipilimumab are likely to be greater during the second and third trimesters of pregnancy. Human IgG1 is known to cross the placental barrier and ipilimumab is an IgG1; therefore, ipilimumab has the potential to be transmitted from the mother to the developing fetus. Advise pregnant women of the potential risk to a fetus. Report pregnancies to Bristol-Myers Squibb at 1-844-593-7869.

In the U.S. general population, the estimated background risk of major birth defects and miscarriage in clinically recognized pregnancies is 2% to 4% and 15% to 20%, respectively.

Data

Animal Data

In a combined study of embryo-fetal and peri-postnatal development, pregnant cynomolgus monkeys received ipilimumab every 3 weeks from the onset of organogenesis in the first trimester through parturition. No treatment-related adverse effects on reproduction were detected during the first two trimesters of pregnancy. Beginning in the third trimester, administration of ipilimumab at doses resulting in exposures approximately 2.6 to 7.2 times the human exposure at a dose of 3 mg/kg resulted in dose-related increases in abortion, stillbirth, premature delivery (with corresponding lower birth weight), and an increased incidence of infant mortality. In addition, developmental abnormalities were identified in the urogenital system of 2 infant monkeys exposed in utero to 30 mg/kg of ipilimumab (7.2 times the humans exposure based on area under the curve at a dose of 3 mg/kg). One female infant monkey had unilateral renal agenesis of the left kidney and ureter, and 1 male infant monkey had an imperforate urethra with associated urinary obstruction and subcutaneous scrotal edema.

Genetically engineered mice heterozygous for CTLA-4 (CTLA-4+/−), the target for ipilimumab, appeared healthy and gave birth to healthy CTLA-4+/− heterozygous offspring. Mated CTLA-4+/− heterozygous mice also produced offspring deficient in CTLA-4 (homozygous negative, CTLA-4−/−). The CTLA-4−/− homozygous negative offspring appeared healthy at birth, exhibited signs of multiorgan lymphoproliferative disease by 2 weeks of age, and all died by 3 to 4 weeks of age with massive lymphoproliferation and multiorgan tissue destruction.

8.2 Lactation

Risk Summary

There are no data on the presence of YERVOY in human milk or its effects on the breastfed child or milk production. In monkeys, ipilimumab was present in milk (see Data). Because of the potential for serious adverse reactions in breastfed children, advise women not to breastfeed during treatment with YERVOY and for 3 months following the last dose.

Data

In monkeys treated at dose levels resulting in exposures 2.6 and 7.2 times higher than those in humans at a 3 mg/kg dose, ipilimumab was present in milk at concentrations of 0.1 mcg/mL and 0.4 mcg/mL, representing a ratio of up to 0.3% of the steady-state serum concentration of the drug.

8.3 Females and Males of Reproductive Potential

Pregnancy Testing

Verify pregnancy status in females of reproductive potential prior to initiating YERVOY [see Use in Specific Populations (8.1)].

Contraception

YERVOY can cause fetal harm when administered to a pregnant woman [see Use in Specific Populations (8.1)]. Advise females of reproductive potential to use effective contraception during treatment with YERVOY and for 3 months following the last dose.

8.4 Pediatric Use

The safety and effectiveness of YERVOY have been established in pediatric patients aged 12 years and older for the following indications: as a single agent and in combination with nivolumab for unresectable or metastatic melanoma, in combination with nivolumab for the treatment of MSI-H or dMMR unresectable and metastatic CRC, and in combination with nivolumab for MSI-H or dMMR mCRC that has progressed following treatment with a fluoropyrimidine, oxaliplatin, and irinotecan. Use of YERVOY for these indications is supported by evidence from adequate and well-controlled studies in adults with melanoma or MSI-H or dMMR mCRC and additional pharmacokinetic data in pediatric patients. Ipilimumab exposures in pediatric patients 12 years and older are comparable to that of adults, and the courses of melanoma and MSI-H or dMMR mCRC are similar in pediatric patients aged 12 years and older to that of adults to allow extrapolation of safety and efficacy [see Adverse Reactions (6.1), Clinical Pharmacology (12.3), Clinical Studies (14.4)].

The safety and effectiveness of YERVOY have not been established in pediatric patients younger than 12 years old with unresectable or metastatic melanoma or MSI-H or dMMR mCRC.

The safety and effectiveness of YERVOY have not been established in pediatric patients for the adjuvant treatment of melanoma or for the treatment of advanced renal cell carcinoma, hepatocellular carcinoma, metastatic non-small cell lung cancer, malignant pleural mesothelioma and esophageal cancer.

In a dose-finding trial (NCT01445379), 33 patients aged 2 to 21 years (median 13 years) with relapsed or refractory solid tumors were evaluated including unresectable stage IIIc or stage IV melanoma (12), progressive or refractory sarcomas (17), renal or bladder carcinoma (3), and neuroblastoma (1). No responses in the patients with non-melanoma solid tumors and no new safety signals were observed in pediatric patients in this study.

8.5 Geriatric Use

Single Agent

Of the 511 patients treated with YERVOY in Study MDX010-20 (unresectable or metastatic melanoma), 28% were 65 years and over. No overall differences in safety or effectiveness were observed between these patients and younger patients.

In Combination with Nivolumab

Of the 314 patients randomized to YERVOY administered with nivolumab in CHECKMATE-067, 41% were 65 years or older and 11% were 75 years or older. No overall differences in safety or effectiveness were reported between elderly patients and younger patients.

Of the 576 patients randomized to YERVOY 1 mg/kg every 6 weeks with nivolumab 3 mg/kg every 2 weeks in CHECKMATE-227 (NSCLC), 48% were 65 years or older and 10% were 75 years or older. No overall difference in safety was reported between older patients and younger patients; however, there was a higher discontinuation rate due to adverse reactions in patients aged 75 years or older (29%) relative to all patients who received YERVOY with nivolumab (18%). Of the 396 patients in the primary efficacy population (PD-L1 ≥1%) randomized to YERVOY 1 mg/kg every 6 weeks with nivolumab 3 mg/kg every 2 weeks in CHECKMATE-227, the hazard ratio for overall survival was 0.70 (95% CI: 0.55, 0.89) in the 199 patients younger than 65 years compared to 0.91 (95% CI: 0.72, 1.15) in the 197 patients 65 years or older [see Clinical Studies (14.6)].

Of the 303 patients randomized to YERVOY 1 mg/kg every 6 weeks in combination with nivolumab 3 mg/kg every 2 weeks in CHECKMATE-743 (malignant pleural mesothelioma), 77% were 65 years old or older and 26% were 75 years or older. No overall difference in safety was reported between older patients and younger patients; however, there were higher rates of serious adverse reactions and discontinuation rate due to adverse reactions in patients aged 75 years or older (68% and 35%, respectively) relative to all patients who received YERVOY with nivolumab (54% and 28%, respectively). For patients aged 75 years or older who received chemotherapy, the rate of serious adverse reactions was 34% and discontinuation due to adverse reactions was 26% relative to 28% and 19% respectively for all patients. The hazard ratio for overall survival was 0.76 (95% CI: 0.52, 1.11) in the 71 patients younger than 65 years compared to 0.74 (95% CI: 0.59, 0.93) in the 232 patients 65 years or older randomized to YERVOY in combination with nivolumab.

Of the 550 patients randomized to YERVOY 1 mg/kg with nivolumab in CHECKMATE-214 (renal cell carcinoma), 38% were 65 years or older and 8% were 75 years or older. No overall difference in safety was observed between these patients and younger patients. In geriatric patients with intermediate or poor risk, no overall difference in effectiveness was observed.

Of the 354 patients with dMMR or MSI-H metastatic CRC (mCRC) who were randomized to YERVOY in combination with nivolumab, 44% were 65 years or older and 14% were 75 years or older. Of the 353 patients randomized to nivolumab, as a single agent, 45% were 65 years or older and 13% were 75 years or older. There was a higher incidence of any Grade 3 or 4 adverse reactions (55%) in patients aged 65 years or older receiving YERVOY in combination with nivolumab compared to those younger than 65 receiving the combination (42%). There was a higher incidence of adverse reactions leading to discontinuation in patients aged 65 years or older receiving YERVOY in combination with nivolumab (23%) compared to those younger than 65 receiving the combination (15%). No overall differences in effectiveness were reported between elderly patients and younger patients receiving YERVOY in combination with nivolumab [see Clinical Studies (14.4)].

Of the 335 patients with unresectable hepatocellular carcinoma who were randomized to YERVOY in combination with nivolumab, 52% were 65 years or older and 14% were 75 years or older. No overall difference in safety was reported between elderly patients and younger patients.

Of the 49 patients who received YERVOY 3 mg/kg with nivolumab in Cohort 4 of CHECKMATE-040 (previously treated hepatocellular carcinoma), 29% were between 65 years and 74 years of age and 8% were 75 years or older. Clinical studies of YERVOY in combination with nivolumab did not include sufficient numbers of patients with hepatocellular carcinoma aged 65 and over to determine whether they respond differently from younger patients.

Of the 325 patients who received YERVOY 1 mg/kg every 6 weeks in combination with nivolumab 3 mg/kg every 2 weeks in CHECKMATE-648 (ESCC), 43% were 65 years old or older and 7% were 75 years or older. No overall difference in safety was reported between older patients and younger patients; however, there was a higher discontinuation rate due to adverse reactions in patients aged 75 years or older (38%) relative to all patients who received YERVOY with nivolumab (23%). For patients aged 75 years or older who received chemotherapy, the discontinuation rate due to adverse reactions was 33% relative to 23% for all patients.

Study CA184-029 (adjuvant treatment of melanoma) and CHECKMATE-142 (metastatic colorectal cancer) did not include sufficient numbers of patients aged 65 years and older to determine whether they respond differently from younger patients.

In Combination with Nivolumab and Platinum-Doublet Chemotherapy

Of the 361 patients randomized to YERVOY 1 mg/kg every 6 weeks in combination with nivolumab 360 mg every 3 weeks and platinum-doublet chemotherapy every 3 weeks (for 2 cycles) in CHECKMATE-9LA (NSCLC), 51% were 65 years or older and 10% were 75 years or older. No overall difference in safety was reported between older patients and younger patients; however, there was a higher discontinuation rate due to adverse reactions in patients aged 75 years or older (43%) relative to all patients who received YERVOY with nivolumab and chemotherapy (24%). For patients aged 75 years or older who received chemotherapy only, the discontinuation rate due to adverse reactions was 16% relative to all patients who had a discontinuation rate of 13%. Based on an updated analysis for overall survival, of the 361 patients randomized to YERVOY in combination with nivolumab and platinum-doublet chemotherapy in CHECKMATE-9LA, the hazard ratio for overall survival was 0.61 (95% CI: 0.47, 0.80) in the 176 patients younger than 65 years compared to 0.73 (95% CI: 0.56, 0.95) in the 185 patients 65 years or older.

11 DESCRIPTION

Ipilimumab is a human cytotoxic T-lymphocyte antigen 4 (CTLA-4)-blocking antibody. Ipilimumab is a recombinant IgG1 kappa immunoglobulin with an approximate molecular weight of 148 kDa. Ipilimumab is produced in mammalian (Chinese hamster ovary) cell culture.

YERVOY (ipilimumab) injection, for intravenous use is a sterile, preservative-free, clear to slightly opalescent, colorless to pale-yellow solution, which may contain a small amount of visible translucent-to-white, amorphous ipilimumab particulates. It is supplied in single-dose vials of 50 mg/10 mL or 200 mg/40 mL. Each milliliter contains 5 mg of ipilimumab and the following inactive ingredients: diethylene triamine pentaacetic acid (DTPA) (0.04 mg), mannitol (10 mg), polysorbate 80 (vegetable origin) (0.1 mg), sodium chloride (5.85 mg), tris hydrochloride (3.15 mg), and Water for Injection, USP at a pH of 7.

12 CLINICAL PHARMACOLOGY

12.1 Mechanism of Action

CTLA-4 is a negative regulator of T-cell activity. Ipilimumab is a monoclonal antibody that binds to CTLA-4 and blocks the interaction of CTLA-4 with its ligands, CD80/CD86. Blockade of CTLA-4 has been shown to augment T-cell activation and proliferation, including the activation and proliferation of tumor infiltrating T-effector cells. Inhibition of CTLA-4 signaling can also reduce T-regulatory cell function, which may contribute to a general increase in T-cell responsiveness, including the anti-tumor immune response.

12.3 Pharmacokinetics

The pharmacokinetics (PK) of ipilimumab was studied in 785 patients with unresectable or metastatic melanoma who received doses of 0.3, 3, or 10 mg/kg once every 3 weeks for 4 doses. The PK of ipilimumab is linear in the dose range of 0.3 mg/kg to 10 mg/kg. Following administration of YERVOY every 3 weeks, the systemic accumulation was 1.5-fold or less. Steady-state concentrations of ipilimumab were reached by the third dose; the mean minimum concentration (Cmin) at steady state was 19.4 mcg/mL at 3 mg/kg and 58.1 mcg/mL at 10 mg/kg every 3 weeks.

Elimination

The mean (percent coefficient of variation) terminal half-life (t1/2) was 15.4 days (34%) and then mean (percent coefficient of variation) clearance (CL) was 16.8 mL/h (38%).

The CL of ipilimumab was unchanged in presence of anti-ipilimumab antibodies.

Specific Populations

The CL of ipilimumab increased with increasing body weight supporting the recommended body weight (mg/kg) based dosing. The following factors had no clinically important effect on the CL of ipilimumab: age (range: 23 to 88 years), sex, performance status, renal impairment (glomerular filtration rate ≥15 mL/min/1.73 m^2), mild hepatic impairment (total bilirubin [TB] >1 to 1.5 times the upper limit of normal [ULN] or AST > ULN), previous cancer therapy, and baseline lactate dehydrogenase (LDH) levels. The effect of race was not examined due to limited data available in non-White racial groups. YERVOY has not been studied in patients with moderate (TB >1.5 to 3 times ULN and any AST) or severe (TB >3 times ULN and any AST) hepatic impairment.

Pediatric Patients

The exposures of ipilimumab in pediatric patients 12 years and older are comparable to those in adult patients at the recommended dosage.

Drug Interaction Studies

Ipilimumab with Nivolumab

When YERVOY 1 mg/kg was administered with nivolumab 3 mg/kg every 3 weeks, the CL of ipilimumab was unchanged compared to when YERVOY was administered alone.

When YERVOY 3 mg/kg every 3 weeks was administered in combination with nivolumab 1 mg/kg every 3 weeks, the CL of ipilimumab was unchanged compared to ipilimumab administered alone and the CL of nivolumab was increased by 29% compared to nivolumab administered alone.

When YERVOY 1 mg/kg every 6 weeks was administered in combination with nivolumab 3 mg/kg every 2 weeks, the CL of ipilimumab increased by 30% compared to YERVOY administered alone and the CL of nivolumab was unchanged compared to nivolumab administered alone.

When YERVOY 1 mg/kg every 6 weeks was administered in combination with nivolumab 360 mg every 3 weeks and chemotherapy, the CL of ipilimumab increased by 22% compared to YERVOY administered alone and the CL of nivolumab was unchanged compared to nivolumab administered alone.

12.6 Immunogenicity

The observed incidence of anti-drug antibodies (ADA) is highly dependent on the sensitivity and specificity of the assay. Differences in assay methods preclude meaningful comparisons of the incidence of ADA in the studies described below with the incidence of ADA in other studies, including those of YERVOY or of other ipilimumab products.

Eleven (1.1%) of 1024 evaluable patients with unresectable or metastatic melanoma tested positive for treatment-emergent binding antibodies against ipilimumab in an electrochemiluminescent (ECL) based assay. This assay had substantial limitations in detecting anti-ipilimumab antibodies in the presence of ipilimumab. Seven (4.9%) of 144 patients receiving ipilimumab developed anti-ipilimumab antibodies and 7 (4.5%) of 156 patients receiving placebo for the adjuvant treatment of melanoma tested positive for anti-ipilimumab antibodies using an ECL assay with improved drug tolerance. No patients tested positive for neutralizing antibodies. No infusion-related reactions occurred in patients who tested positive for anti-ipilimumab antibodies.

Of the 499 patients evaluable for anti-ipilimumab antibodies in CHECKMATE-214 and CHECKMATE-142, 27 (5.4%) were positive for anti-ipilimumab antibodies; there were no patients with neutralizing antibodies against ipilimumab. There was no evidence of increased incidence of infusion reactions to YERVOY in patients with anti-ipilimumab antibodies.

Of 483 patients evaluable for anti-ipilimumab antibodies in CHECKMATE-227 Part 1, 8.5% were positive for treatment-emergent anti-ipilimumab antibodies. No patients had neutralizing antibodies against ipilimumab. In Part 1 of the same study, of 491 patients evaluable for anti-nivolumab antibodies, 36.7% were positive for anti-nivolumab antibodies and 1.4% had neutralizing antibodies against nivolumab.

Of 305 patients evaluable for anti-ipilimumab antibodies in CHECKMATE-9LA, 8% were positive for anti-ipilimumab antibodies and 1.6% were positive for anti-ipilimumab neutralizing antibodies. There was no evidence of increased incidence of infusion reactions to YERVOY in patients with anti-ipilimumab antibodies. Of 308 patients evaluable for anti-nivolumab antibodies in CHECKMATE-9LA, 34% were positive for anti-nivolumab antibodies and 2.6% had neutralizing antibodies against nivolumab.

Of 271 patients evaluable for anti-ipilimumab antibodies in CHECKMATE-743, 13.7% were positive for anti-ipilimumab antibodies and 0.4% were positive for anti-ipilimumab neutralizing antibodies. Of 269 patients evaluable for anti-nivolumab antibodies in CHECKMATE-743, 25.7% were positive for anti-nivolumab antibodies and 0.7% had neutralizing antibodies against nivolumab.

Anti-drug antibody and neutralizing antibody responses were monitored throughout the treatment period where the benefit to risk ratio was assessed. Incidence of anti-drug antibodies and neutralizing antibodies are presented in Table 24.

Table 24: YERVOY Anti-Drug Antibody (ADA) and Neutralizing Antibody (NAb) Incidence
Treatment Regimena | Indication(s) | ADA | NAbb
YERVOY as a single agent | Melanoma | 1.1%; (11/1024) | 0; (0/11)
YERVOY as a single agent | Adjuvant Melanoma | 4.9; (7/144) | 0; (0/7)
YERVOY with nivolumab for 4 doses followed by nivolumab as a single agent | Melanoma | 8.4%; (33/391) | 3%; (1/33)
YERVOY with nivolumab for 4 doses followed by nivolumab as a single agent | HCC | 5.3%; (13/244) | 0; (0/13)
YERVOY with nivolumab for 4 doses followed by nivolumab as a single agent | RCC and CRC | 5.4%; (27/499) | 0%; (0/27)
YERVOY with nivolumab | Malignant Pleural Mesothelioma | 13.7%; (37/271) | 2.7%; (1/37)
YERVOY with nivolumab | NSCLC | 8.5%; (41/483) | 0; (0/41)
YERVOY with nivolumab and 2 cycles of platinum-doublet chemotherapy | NSCLC | 7.5%; (23/305) | 21.7%; (5/23)
a Details of each treatment regimen are described in Section 14 [see Clinical Studies (14)].
b NAb incidence is reported among the subset of patients positive for ADA.
ADA = treatment-emergent anti-ipilimumab antibodies, NAb = neutralizing antibodies, HCC = hepatocellular carcinoma, RCC = renal cell carcinoma, CRC = colorectal cancer, NSCLC = non-small cell lung cancer.

Effects of Anti-Drug Antibodies

Presence of treatment-emergent anti-ipilimumab antibodies did not affect ipilimumab clearance after administration of ipilimumab as monotherapy or in combination with nivolumab. These anti-drug antibody-associated pharmacokinetic changes were not considered to be clinically significant. There was no identified clinically significant effect of anti-drug antibodies on incidence of infusion-related reactions. In hepatocellular carcinoma, there was no identified clinically significant effect of anti-drug antibodies on efficacy for ipilimumab in combination with nivolumab. For other indications, the effects of anti-drug antibodies on effectiveness have not been fully characterized.

13 NONCLINICAL TOXICOLOGY

13.1 Carcinogenesis, Mutagenesis, Impairment of Fertility

The carcinogenic potential of ipilimumab has not been evaluated in long-term animal studies, and the genotoxic potential of ipilimumab has not been evaluated.

Fertility studies have not been performed with ipilimumab.

14 CLINICAL STUDIES

14.1 Unresectable or Metastatic Melanoma

The efficacy of YERVOY was investigated in a Study MDX010-20, a randomized (3:1:1), double-blind, double-dummy trial (NCT00094653) that included patients with unresectable or metastatic melanoma previously treated with one or more of the following: aldesleukin, dacarbazine, temozolomide, fotemustine, or carboplatin. The trial enrolled only patients with HLA-A2*0201 genotype; this HLA genotype facilitates the immune presentation of the investigational peptide vaccine. The trial excluded patients with active autoimmune disease or those receiving systemic immunosuppression for organ transplantation. Patients were randomized to YERVOY administered at a dose of 3 mg/kg as an intravenous infusion every 3 weeks for 4 doses with an investigational peptide vaccine with incomplete Freund’s adjuvant - gp100 administered at a dose of 2 mg peptide by deep subcutaneous injection every 3 weeks for 4 doses; gp100 administered at a dose of 2 mg by deep subcutaneous injection every 3 weeks for 4 doses as a single agent with a placebo; or YERVOY administered at a dose of 3 mg/kg by intravenous infusion every 3 weeks for 4 doses with a placebo. The major efficacy outcome measure was overall survival (OS) in the YERVOY and gp100 arm compared to that in the single-agent gp100 arm. Secondary efficacy outcome measures were OS in the YERVOY and gp100 arm compared to the YERVOY arm, OS in the YERVOY arm compared to the gp100 arm, best overall response rate (BORR) as assessed by the investigator at week 24 between each of the trial arms, and duration of response. Assessment of tumor response was conducted at weeks 12 and 24, and every 3 months thereafter. Patients with evidence of objective tumor response at 12 or 24 weeks had assessment for confirmation of durability of response at 16 or 28 weeks, respectively.

A total of 676 patients were randomized, 403 to YERVOY and gp100 arm, 137 to YERVOY single agent arm and 136 to gp100 single agent arm. Of the randomized patients, 61%, 59%, and 54% in the YERVOY and gp100, YERVOY, and gp100 arms, respectively, were male. Twenty-nine percent were ≥65 years of age, the median age was 57 years, 71% had M1c stage, 12% had a history of previously treated brain metastasis, 98% had ECOG performance status of 0 and 1, 23% had received aldesleukin, and 38% had elevated LDH level. Sixty-one percent of patients randomized to either YERVOY-containing arm received all 4 planned doses. The median duration of follow-up was 8.9 months.

The efficacy results are shown in Table 25 and Figure 1.

Table 25: Efficacy Results for Study MDX010-20
 | YERVOY 3 mg/kg; n=137 | YERVOY 3 mg/kg and gp100 n=403 | gp100; n=136
Overall Survival
Median in months (95% CI) | 10 (8.0, 13.8) | 10 (8.5, 11.5) | 6 (5.5, 8.7)
Hazard ratio (vs. gp100) (95% CI) | 0.66 (0.51, 0.87) | 0.68 (0.55, 0.85)
p-value | p=0.0026a | p=0.0004
Hazard ratio (vs. YERVOY) (95% CI) |  | 1.04 (0.83, 1.30)
Best Overall Response Rate (BORR); (95% CI) | 10.9%; (6.3%, 17.4%) | 5.7%; (3.7%, 8.4%) | 1.5%; (0.2%, 5.2%)
Median duration of response in months | NRb | 11.5 | NRb
a Not adjusted for multiple comparisons.
b Not Reached

Figure 1: Kaplan-Meier Curves for Overall Survival in Study MDX010-20

Previously Untreated Metastatic Melanoma: In Combination with Nivolumab

CHECKMATE-067 (NCT01844505) was a multicenter, randomized (1:1:1), double-blind trial in which 945 patients with previously untreated, unresectable or metastatic melanoma were randomized to one of the following arms: YERVOY and nivolumab, nivolumab, or YERVOY. Patients were required to have completed adjuvant or neoadjuvant treatment at least 6 weeks prior to randomization and have no prior treatment with anti-CTLA-4 antibody and no evidence of active brain metastasis, ocular melanoma, autoimmune disease, or medical conditions requiring systemic immunosuppression.

Patients were randomized to receive:

- YERVOY 3 mg/kg with nivolumab 1 mg/kg intravenously every 3 weeks for 4 doses, followed by nivolumab as a single agent at a dose of 3 mg/kg by intravenous infusion every 2 weeks (YERVOY and nivolumab arm),
- Nivolumab 3 mg/kg by intravenous infusion every 2 weeks (nivolumab arm), or
- YERVOY 3 mg/kg intravenously every 3 weeks for 4 doses followed by placebo every 2 weeks (YERVOY arm)

Randomization was stratified by PD-L1 expression (≥5% vs. <5% tumor cell membrane expression) as determined by a clinical trial assay, BRAF V600 mutation status, and M stage per the AJCC staging system (M0, M1a, M1b vs. M1c). Tumor assessments were conducted 12 weeks after randomization then every 6 weeks for the first year, and every 12 weeks thereafter. The major efficacy outcome measures were investigator-assessed PFS per RECIST v1.1 and OS. Additional efficacy outcome measures were confirmed ORR and duration of response.

The trial population characteristics were: median age 61 years (range: 18 to 90); 65% male; 97% White; ECOG performance score 0 (73%) or 1 (27%). Disease characteristics were: AJCC Stage IV disease (93%); M1c disease (58%); elevated LDH (36%); history of brain metastases (4%); BRAF V600 mutation-positive melanoma (32%); PD-L1 ≥5% tumor cell membrane expression as determined by the clinical trials assay (46%); and prior adjuvant therapy (22%).

CHECKMATE-067 demonstrated statistically significant improvements in OS and PFS for patients randomized to either nivolumab-containing arm as compared with the YERVOY arm. The trial was not designed to assess whether adding YERVOY to nivolumab improves PFS or OS compared to nivolumab as a single agent. Efficacy results are shown in Table 26 and Figure 2.

Table 26: Efficacy Results - CHECKMATE-067
 | YERVOY and Nivolumab (n=314) | Nivolumab (n=316) | YERVOY (n=315)
Overall Survivala
Deaths (%) | 128 (41) | 142 (45) | 197 (63)
Hazard ratiob (vs. YERVOY); (95% CI) | 0.55; (0.44, 0.69) | 0.63; (0.50, 0.78)
p-valuec, d | <0.0001 | <0.0001
Progression-free Survivala
Disease progression or death | 151 (48%) | 174 (55%) | 234 (74%)
Median (months); (95% CI) | 11.5 (8.9, 16.7) | 6.9 (4.3, 9.5) | 2.9 (2.8, 3.4)
Hazard ratiob (vs. YERVOY); (95% CI) | 0.42; (0.34, 0.51) | 0.57; (0.47, 0.69)
p-valuec, e | <0.0001 | <0.0001
Confirmed Overall Response Ratea | 50% | 40% | 14%
(95% CI) | (44, 55) | (34, 46) | (10, 18)
p-valuef | <0.0001 | <0.0001
Complete response | 8.9% | 8.5% | 1.9%
Partial response | 41% | 31% | 12%
Duration of Response
Proportion ≥6 months in duration | 76% | 74% | 63%
Range (months) | 1.2+ to 15.8+ | 1.3+ to 14.6+ | 1.0+ to 13.8+
a OS results are based on final OS analysis with 28 months of minimum follow-up; PFS (co-primary endpoint) and ORR (secondary endpoint) results were based on primary analysis with 9 months of minimum follow-up.
b Based on a stratified proportional hazards model.
c Based on stratified log-rank test.
d If the maximum of the two OS p-values is less than 0.04 (a significance level assigned by the Hochberg procedure), then both p-values are considered significant.
e p-value is compared with 0.005 of the allocated alpha for final PFS treatment comparisons.
f Based on the stratified Cochran-Mantel-Haenszel test.
+ Censored observation

Figure 2: Overall Survival - CHECKMATE-067

Based on a minimum follow-up of 48 months, the median OS was not reached (95% CI: 38.2, NR) in the YERVOY and nivolumab arm. The median OS was 36.9 months (95% CI: 28.3, NR) in the nivolumab arm and 19.9 months (95% CI: 16.9, 24.6) in the YERVOY arm.

Based on a minimum follow-up of 28 months, the median PFS was 11.7 months (95% CI: 8.9, 21.9) in the YERVOY and nivolumab arm, 6.9 months (95% CI: 4.3, 9.5) in the nivolumab arm, and 2.9 months (95% CI: 2.8, 3.2) in the YERVOY arm. Based on a minimum follow-up of 28 months, the proportion of responses lasting ≥24 months was 55% in the YERVOY and nivolumab arm, 56% in the nivolumab arm, and 39% in the YERVOY arm.

14.2 Adjuvant Treatment of Melanoma

The efficacy of YERVOY was evaluated in Study E1609 (NCT01274338), an open-label, multicenter, randomized trial for the adjuvant treatment of cutaneous melanoma in patients with completely resected node positive disease (either clinically detectable or any size with ulceration or mitosis ≥1/mm^2), in transit metastasis, satellites, or metastatic disease. The trial excluded patients with a history of prior therapy for melanoma and autoimmune disease requiring steroid treatment. Patients were randomized to receive one of the following regimens:

- YERVOY 3 mg/kg intravenously every 3 weeks for 4 doses, followed by the same dose every 12 weeks for up to 4 additional doses,
- High-dose interferon α-2b (HDI) intravenously at 20 million units/m^2 per day, 5 days per week, for 4 weeks (induction), followed by 10 million units/m^2 per day SC every other day, 3 days per week, for 48 weeks (maintenance), or
- YERVOY 10 mg/kg intravenously every 3 weeks for 4 doses, followed by the same dose every 12 weeks for up to 4 additional doses.

Randomization was stratiﬁed by AJCC 7th edition stage (IIIB, IIIC, M1a, or M1b). Tumor assessments were conducted every 3 months in patients <2 years from study entry, then every 6 months in patients 2-5 years from study entry, and every 12 months in patients >5 years from study entry for up to 20 years. Treatment continued for a maximum of 60 weeks with ipilimumab or 52 weeks with HDI, or until unacceptable toxic effects, disease progression, or withdrawal of consent. The major efficacy outcome measures were investigator-assessed recurrence-free survival (RFS) by imaging (for CNS lesions) or imaging and positive cytology or histology (for non-CNS lesions) and overall survival (OS). Only the efficacy results for the recommended starting dose of 3 mg/kg YERVOY are described below.

A total of 1051 patients were randomized to YERVOY 3 mg/kg (n=523) and HDI (n=528). The median age was 54 years (range: 18 to 83), 62% were male, 97% were white, 0.3% were Asian, and 0.4% were Black. Regarding disease stage, 53% had Stage IIIB, 40% had Stage IIIC (with no in-transit metastases), and 7% had Stage IV disease.

The efficacy results are in Table 27 and Figure 3.

Table 27: Efficacy Results for E1609
 | YERVOY 3 mg/kg n=523 | HDI n=528
Overall Survival
Number of deaths (%) | 130 (25) | 134 (25)
Hazard ratio (95% CI) | 0.78 (0.61, 0.99)
p-value (stratified log-ranka) | 0.044
5-year OS Rates (95% CI) | 72 (68, 76) | 67 (62, 71)
Recurrence-Free Survival
Number of events (%) | 246 (47) | 232 (44)
Median in years (95% CI) | 4.5 (2.7, NA) | 2.5 (1.8, 3.5)
Hazard ratio (95% CI) | 0.85 (0.71, 1.02)
a Two-sided p-value from log-rank test stratified by AJCC stage.

Figure 3: Kaplan-Meier Curves for Overall Survival with Ipilimumab 3 mg/kg vs. HDI in Study E1609

14.3 Advanced Renal Cell Carcinoma

The efficacy of YERVOY with nivolumab was evaluated in CHECKMATE-214 (NCT02231749), a randomized (1:1), open-label study in patients with previously untreated advanced RCC. Patients were included regardless of their PD-L1 status. CHECKMATE-214 excluded patients with any history of or concurrent brain metastases, active autoimmune disease, or medical conditions requiring systemic immunosuppression. Patients were randomized to nivolumab 3 mg/kg and YERVOY 1 mg/kg administered intravenously every 3 weeks for 4 doses followed by nivolumab 3 mg/kg every two weeks or to sunitinib administered orally 50 mg daily for the first 4 weeks of each 6-week cycle. Treatment continued until disease progression or unacceptable toxicity. Patients were stratified by International Metastatic RCC Database Consortium (IMDC) prognostic score and region. The major efficacy outcome measures were OS, PFS (IRRC-assessed), and confirmed ORR (IRRC-assessed) in intermediate/poor risk patients. Intermediate/poor risk patients had at least 1 or more of 6 prognostic risk factors as per the IMDC criteria: less than one year from time of initial RCC diagnosis to randomization, Karnofsky performance status (KPS) <80%, hemoglobin less than the lower limit of normal, corrected calcium >10 mg/dL, platelet count >ULN, and absolute neutrophil count >ULN.

A total of 847 patients were randomized, 425 to YERVOY with nivolumab and 422 to sunitinib. The median age was 61 years (range: 21 to 85) with 38% ≥65 years of age and 8% ≥75 years of age. The majority of patients were male (73%) and White (87%) and 26% and 74% of patients had a baseline KPS of 70% to 80% and 90% to 100%, respectively.

Efficacy results from CHECKMATE-214 are presented in Table 28 and Figure 4. In intermediate/poor risk patients, the trial demonstrated statistically significant improvement in OS and ORR for patients randomized to YERVOY and nivolumab arm as compared with sunitinib arm. OS benefit was observed regardless of PD-L1 expression level. The trial did not demonstrate a statistically significant improvement in PFS.

Table 28: Efficacy Results for CHECKMATE-214
Efficacy Parameter | Intermediate/Poor-Risk
 | YERVOY 1 mg/kg and Nivolumab n=425 | Sunitinib n=422
Overall Survival
Number of deaths | 140 (32.9%) | 188 (44.5%)
Median in months | NE | 25.9
Hazard ratio (99.8% CI)a | 0.63 (0.44, 0.89)
p-valueb,c | <0.0001
Confirmed Objective Response Rate (95% CI) | 41.6% (36.9%, 46.5%) | 26.5% (22.4%, 31.0%)
Complete Response | 40 (9.4%) | 5 (1.2%)
Partial Response | 137 (32.2%) | 107 (25.4%)
Median duration of response in months (95% CI) | NE (21.8, NE) | 18.2 (14.8, NE)
p-valued,e | <0.0001
Progression-free Survival
Number of events (progression or death) | 228 (53.6%) | 228 (54.0%)
Median in months | 11.6 | 8.4
Hazard ratio (99.1% CI)a | 0.82 (0.64, 1.05)
p-valueb | NSf
a Based on a stratified proportional hazards model.
b Based on a stratified log-rank test.
c p-value is compared to alpha 0.002 in order to achieve statistical significance.
d Based on the stratified DerSimonian-Laird test.
e p-value is compared to alpha 0.001 in order to achieve statistical significance.
f Not Significant at alpha level of 0.009.

Figure 4: Kaplan-Meier Curves for Overall Survival (Intermediate/Poor Risk Population) in CHECKMATE-214

CHECKMATE-214 also randomized 249 favorable risk patients as per IMDC criteria to nivolumab and YERVOY (n=125) or to sunitinib (n=124). These patients were not evaluated as part of the efficacy analysis population. OS in favorable risk patients receiving nivolumab and YERVOY compared to sunitinib has a hazard ratio of 1.45 (95% CI: 0.75, 2.81). The efficacy of nivolumab and YERVOY in previously untreated renal cell carcinoma with favorable risk disease has not been established.

14.4 Microsatellite Instability-High or Mismatch Repair Deficient Metastatic Colorectal Cancer

Treatment of MSI-H or dMMR mCRC In Combination with Nivolumab

CHECKMATE-8HW (NCT03143153) was a randomized, 3-arm, open-label trial in immunotherapy-naive patients across all lines of therapy with unresectable or metastatic CRC with known tumor MSI-H or dMMR (MSI-H/dMMR) status as determined in accordance with local standard of practice using PCR, NGS or IHC, assays. Central assessment of MSI-H status using PCR (Idylla MSI) test and dMMR status using IHC (Omnis MMR) test was conducted retrospectively on patient tumor specimens used for local MSI-H/dMMR status determination. Patients with confirmed MSI-H/dMMR status by either central test comprised the primary study population.

The trial excluded patients with brain metastasis that were symptomatic, had active autoimmune disease, used systemic corticosteroids or immunosuppressants, or had been treated with checkpoint inhibitors.

Patients were randomized to receive one of the following treatments:

- YERVOY 1 mg/kg every 3 weeks and nivolumab 240 mg every 3 weeks for a maximum of 4 doses, then nivolumab 480 mg every 4 weeks
- Nivolumab 240 mg every 2 weeks for 6 doses, then nivolumab 480 mg every 4 weeks.
- Investigator’s choice chemotherapy
  - mFOLFOX6 (oxaliplatin, leucovorin, and FU) with or without either bevacizumab or cetuximab: Oxaliplatin 85 mg/m^2, leucovorin 400 mg/m^2, and FU 400 mg/m^2 bolus followed by FU 2400 mg/m^2 over 46 hours every 2 weeks. Bevacizumab 5 mg/kg or cetuximab 500 mg/m^2 administered prior to mFOLFOX6 every 2 weeks.
  - FOLFIRI (irinotecan, leucovorin, and FU) with or without either bevacizumab or cetuximab: Irinotecan 180 mg/m^2, leucovorin 400 mg/m^2, and FU 400 mg/m^2 bolus and FU 2400 mg/m^2 over 46 hours every 2 weeks. Bevacizumab 5 mg/kg on or cetuximab 500 mg/m^2 administered prior to FOLFIRI every 2 weeks.

Randomization was stratified by tumor location (right vs left) and by prior lines of therapy (0, 1, 2L+). Patients randomized to the chemotherapy arm could receive YERVOY plus nivolumab combination upon progression assessed by BICR.

Study treatment was administered until disease progression, unacceptable toxicity, or for up to 2 years for patients who received YERVOY plus nivolumab or nivolumab monotherapy. Patients who discontinued combination therapy because of an adverse reaction attributed to YERVOY were permitted to continue nivolumab as a single agent. Nivolumab with or without YERVOY could be administered beyond RECIST 1.1-assessed progressive disease if there was a clinical benefit as determined by investigator and therapy was tolerated. Tumor assessments per RECIST v1.1 were conducted every 6 weeks for the first 24 weeks, then every 8 weeks thereafter up until week 96, then every 16 weeks thereafter up until week 144, and then every 24 weeks.

The evaluation of efficacy relied on the comparison of patients with centrally confirmed MSI-H/dMMR mCRC randomized to YERVOY in combination with nivolumab versus chemotherapy in the first-line (1L) setting and the comparison of patients with centrally confirmed MSI-H/dMMR mCRC randomized to YERVOY in combination with nivolumab vs nivolumab in all lines setting.

The major efficacy outcome measure was BICR-assessed PFS per RECIST 1.1. Additional efficacy measures included ORR and duration of response assessed by BICR and OS.

The baseline characteristics of the total of 839 patients randomized were: the median age was 63 years (range: 20 to 87), with 46% ≥65 years of age and 14% ≥75 years of age; 50% were male and 87% were White, 9.3% were Asian, 1.5% Black or African American, and 2.3% other race; 9.2% were Hispanic or Latino, 50% Not Hispanic or Latino, 41% ethnicity unknown. Baseline ECOG performance status was 0 (52%) and (48%); number of prior lines of therapy was 0 (56%) and 1 (24%), and ≥2 (19%); tumor location was right-sided or left-sided for 69% and 31% of patients. The baseline characteristics in patients with centrally confirmed MSI-H/dMMR is consistent with all randomized patients.

First Line YERVOY in combination with nivolumab

Among 303 patients in the first-line setting were randomly assigned to YERVOY in combination with nivolumab (202) and to chemotherapy (101), 171 and 84 patients had centrally confirmed MSI-H/dMMR status in YERVOY in combination with nivolumab arm and chemotherapy arm, respectively.

In the 1L setting, 200 of 202 patients assigned to receive YERVOY in combination with nivolumab and 88 of 101 patients assigned to received chemotherapy received at least 1 dose of study treatment. Among the 88 patients who received chemotherapy, 58% and 42% of patients received oxaliplatin-containing regimens and irinotecan-containing regimens, respectively, and 66 (75%) patients received a targeted agent, either bevacizumab (64%) or cetuximab (11%).

The BICR-assessed PFS efficacy results for patients with centrally confirmed MSI-H/dMMR randomized to the YERVOY and nivolumab arm compared with chemotherapy in the 1L setting are presented in Table 29 and Figure 5. The comparative results of ORR and OS between arms were not available at the time of the PFS analysis due to statistical testing strategy.

Table 29: Efficacy Results - CHECKMATE-8HW
 | YERVOY and Nivolumab (n=171) | Chemotherapy (n=84)
Progression-free Survival
Disease progression or death (%) | 48 (28) | 52 (62)
Median in monthsb (95% CI) | NR; (38.4, NE) | 5.8; (4.4, 7.8)
Hazard ratioc (95% CI) | 0.21 (0.14, 0.32)
p-valuea | <0.0001
NR: Not Reached; NE: Not Estimable.
Minimum follow-up was 6.1 months at data cutoff date 12Oct2023.
a Based on log-rank test stratified by the same factors as used in the Cox proportional hazards model. The p-value threshold for statistical significance was 0.0209.
b Based on Kaplan-Meier estimates.
c HR from a Cox proportional hazards model stratified by tumor sidedness (left vs right) per IRT

Figure 5: Progression-free Survival, (First line YERVOY + nivolumab vs Chemotherapy)- CHECKMATE-8HW

All Lines YERVOY in combination with nivolumab

Among 707 patients across all treatment lines who were randomly assigned to YERVOY in combination with nivolumab (354) and to nivolumab (353) single agent, 296 and 286 patients had centrally confirmed MSI-H/dMMR status in the YERVOY in combination with nivolumab arm and in the nivolumab arm, respectively. Patients receiving at least 1 dose of study treatment included 352 of 354 patients randomized to OPDIVO in combination with ipilimumab, and 351 of 353 patients randomized to single agent OPDIVO.

The BICR-assessed PFS and ORR efficacy results for patients with centrally confirmed MSI-H/dMMR randomized to the YERVOY in combination with nivolumab compared with nivolumab single agent across all treatment lines setting are presented in Table 30 and Figure 6. At the time of PFS analysis OS between arms were not available due to statistical testing strategy.

Table 30: Efficacy Results All Lines - CHECKMATE-8HW
 | YERVOY and Nivolumab (n=296) | Nivolumab (n=286)
Progression-free Survival
Disease progression or death n (%) | 101 (34) | 136 (48)
Median (months)b; (95% CI) | NR; (53.82, NE) | 39.3; (22.1, NE)
Hazard ratioc (95% CI) | 0.62 (0.48, 0.81)
p-valuea | 0.0003
Objective Response Rate (ORR)
Response Rate, n (%); (95% CI) | 209 (71%); (65, 76) | 165 (58%); (52, 63)
Complete Response Rate, n (%) | 90 (30%) | 80 (28%)
Partial Response, n (%) | 119 (40%) | 65 (30%)
p-valued | 0.0011
NR: Not Reached; NE: Not Estimable.
Minimum follow-up was 16.7 months at data cutoff date 28Aug2024.
a Based on log-rank test stratified by the same factors as used in the Cox proportional hazards model. The p-value threshold for statistical significance was 0.0095.
b Based on Kaplan-Meier estimates.
c HR from a Cox proportional hazards model stratified by tumor sidedness (left vs right) and prior lines of therapy (0, 1, ≥2) per IRT.
d Based on Cochran-Mantel-Haenszel test stratified by the same factors as used in the Cox proportional hazards model. The p-value threshold for statistical significance was 0.006.

Figure 6: Progression-free Survival (All lines (YERVOY + Nivolumab vs Nivolumab)- CHECKMATE-8HW

14.5 Hepatocellular Carcinoma

Treatment of Unresectable or Metastatic Hepatocellular Carcinoma (HCC)

CHECKMATE-9DW (NCT04039607) was a randomized (1:1), open-label trial in adults (18 years of age or older) with unresectable or metastatic HCC. Patients had histologically confirmed HCC, Child Pugh Class A, ECOG performance status 0 or 1, and no prior systemic therapy for advanced disease. Esophagogastroduodenoscopy was not mandated prior to enrollment. The trial excluded patients with active autoimmune disease, brain or leptomeningeal metastases, a history of hepatic encephalopathy (within 12 months of randomization), a platelet count <60,000, clinically significant ascites, medical conditions requiring systemic immunosuppression, infection with HIV, or active co-infection with hepatitis B virus (HBV) and hepatitis C virus (HCV) or HBV and hepatitis D virus (HDV).

Patients were randomized to receive either:

- YERVOY 3 mg/kg administered intravenously over 30 minutes in combination with nivolumab 1 mg/kg administered intravenously over 30 minutes every 3 weeks, for a maximum of 4 doses, followed by single agent nivolumab at 480 mg administered intravenously over 30 minutes every 4 weeks, or
- Investigator’s choice:
  - Lenvatinib 8 mg orally daily (if body weight <60 kg) or 12 mg orally daily (if body weight ≥60 kg), or
  - Sorafenib 400 mg orally twice daily

Randomization was stratified by etiology (HBV vs. HCV vs. non-viral), macrovascular invasion and/or extrahepatic spread (present or absent), and alpha-fetoprotein levels (≥400 or <400 ng/mL). Study treatment for YERVOY in combination with nivolumab continued until disease progression, unacceptable toxicity, or up to 2 years. Patients who discontinued combination therapy because of an adverse reaction attributed to YERVOY were permitted to continue nivolumab as a single agent. Treatment beyond RECIST 1.1 defined disease progression was permitted if the patient was clinically stable and considered to be deriving clinical benefit by the investigator. Tumor assessments were performed at baseline, after randomization at week 9 and week 16, then every 8 weeks up to 48 weeks, and then every 12 weeks thereafter until disease progression, treatment discontinuation, or initiation of subsequent therapy. The primary efficacy outcome measure was OS in all randomized patients. Additional efficacy measures included BICR-assessed ORR and DOR based on RECIST 1.1 criteria.

A total of 668 patients were randomized to receive YERVOY in combination with nivolumab (n=335) or investigator’s choice (n=333) of lenvatinib or sorafenib. In the investigator arm, 85% and 15% of treated patients received lenvatinib or sorafenib, respectively. The trial population characteristics were: median age was 66 years (range: 20 to 89), with 53% ≥65 years old; 82% male; 53% White, 44% Asian, 2.2% Black; 12% Hispanic or Latino, 48% Not Hispanic or Latino, 40% not reported. Baseline ECOG performance status was 0 (71%) or 1 (29%). Thirty-four percent (34%) of patients had HBV infection, 28% had HCV infection, and 36% had no evidence of HBV or HCV infection.

Nineteen percent (19%) of patients had alcoholic liver disease and 11% had non-alcoholic fatty liver disease. The majority of patients had BCLC stage C (73%) disease at baseline, 19% had stage B, and 6% had stage A. Patients with Child-Pugh scores of 5, 6, and 7 were 77%, 20%, and 3%, respectively; 1 patient with Child Pugh 8 was enrolled. A total of 54% of patients had extrahepatic spread; 25% had macrovascular invasion; and 33% had AFP levels ≥400 µg/L.

CHECKMATE-9DW demonstrated a statistically significant improvement in OS and ORR. The minimum follow-up was 26.8 months. Efficacy results are shown in Table 31 and Figure 7.

Table 31: Efficacy Results - CHECKMATE-9DW
 | YERVOY and Nivolumab (n=335) | Lenvatinib or Sorafenib (n=333)
Overall Survival
Deaths (%) | 194 (58%) | 228 (68%)
Median (months); (95% CI) | 23.7; (18.8, 29.4) | 20.6; (17.5, 22.5)
Hazard ratio (95% CI) a | 0.79 (0.65, 0.96)
p-value b | 0.0180
Overall Response Rate, n (%)c | 121 (36.1) | 44 (13.2)
(95% CI) | (31.0, 41.5) | (9.8, 17.3)
p-value d | <0.0001
Complete response (%) | 23 (6.9) | 6 (1.8)
Partial response (%) | 98 (29.3) | 38 (11.4)
Duration of Response (months) c
Median; (95% CI) | 30.4; (21.2, NRe) | 12.9; (10.2, 31.2)
Range | 1.5+, 36.9+ | 2.1+, 32.5+
a Based on stratified Cox proportional hazard model.
b Based on a 2-sided stratified log-rank test. Boundary for statistical significance: p-value ≤0.0257
c Assessed by BICR using RECIST 1.1
d Based on a 2-sided stratified Cochran-Mantel-Haenszel test. Boundary for statistical significance: p-value ≤0.025
e NR: Not Reached
+ Censored observation

Figure 7: Overall Survival - CHECKMATE-9DW

Previously Treated Hepatocellular Carcinoma

CHECKMATE-040 (NCT01658878) was a multicenter, multiple cohort, open-label trial conducted in patients with HCC who progressed on or were intolerant to sorafenib. Additional eligibility criteria included histologic confirmation of HCC and Child-Pugh Class A cirrhosis. The trial excluded patients with active autoimmune disease, brain metastasis, a history of hepatic encephalopathy, clinically significant ascites, infection with HIV, or active co-infection with hepatitis B virus (HBV) and hepatitis C virus (HCV) or HBV and hepatitis D virus (HDV); however, patients with only active HBV or HCV were eligible.

The efficacy of YERVOY 3 mg/kg in combination with nivolumab 1 mg/kg was evaluated in Cohort 4 of CHECKMATE-040. A total of 49 patients received the combination regimen, which was administered every 3 weeks for four doses, followed by single-agent nivolumab at 240 mg every 2 weeks until disease progression or unacceptable toxicity.

The median age was 60 years (range: 18 to 80); 88% were male; 74% were Asian, and 25% were White. Baseline ECOG performance status was 0 (61%) or 1 (39%). Fifty-seven percent (57%) of patients had active HBV infection, 8% had active HCV infection, and 35% had no evidence of active HBV or HCV. The etiology for HCC was alcoholic liver disease in 16% and non-alcoholic liver disease in 6% of patients. Child-Pugh class and score was A5 for 82% and A6 for 18%; 80% of patients had extrahepatic spread; 35% had vascular invasion; and 51% had alfa-fetoprotein (AFP) levels ≥400 µg/L. Prior treatment history included surgery (74%), radiotherapy (29%), or local treatment (59%). All patients had received prior sorafenib, of whom 10% were unable to tolerate sorafenib; 29% of patients had received 2 or more prior systemic therapies.

Efficacy results are shown in Table 32.

Table 32: Efficacy Results - Cohort 4 of CHECKMATE-040
 | YERVOY and Nivolumab (Cohort 4) (n=49)
Overall Response Rate per BICR,a n (%), RECIST v1.1 | 16 (33%)
(95% CI)b | (20, 48)
Complete response | 4 (8%)
Partial response | 12 (24%)
Duration of Response per BICR,a RECIST v1.1 | n=16
Range (months) | 4.6, 30.5+
Percent with duration ≥6 months | 88%
Percent with duration ≥12 months | 56%
Percent with duration ≥24 months | 31%
Overall Response Rate per BICR,a n (%), mRECIST | 17 (35%)
(95% CI)b | (22, 50)
Complete response | 6 (12%)
Partial response | 11 (22%)
a Confirmed by BICR.
b Confidence interval is based on the Clopper and Pearson method.

14.6 Metastatic Non-Small Cell Lung Cancer

First-line Treatment of Metastatic Non-Small Cell Lung Cancer (NSCLC) Expressing PD-L1 (≥1%): In Combination with Nivolumab

CHECKMATE-227 (NCT02477826) was a randomized, open-label, multi-part trial in patients with metastatic or recurrent NSCLC. The study included patients (18 years of age or older) with histologically confirmed Stage IV or recurrent NSCLC (per the 7th International Association for the Study of Lung Cancer [ASLC] classification), ECOG performance status 0 or 1, and no prior anticancer therapy. Patients were enrolled regardless of their tumor PD-L1 status. Patients with known EGFR mutations or ALK translocations sensitive to available targeted inhibitor therapy, untreated brain metastases, carcinomatous meningitis, active autoimmune disease, or medical conditions requiring systemic immunosuppression were excluded from the study. Patients with treated brain metastases were eligible if neurologically returned to baseline at least 2 weeks prior to enrolment, and either off corticosteroids, or on a stable or decreasing dose of <10 mg daily prednisone equivalents.

Primary efficacy results were based on Part 1a of the study, which was limited to patients with PD-L1 tumor expression ≥1%. Tumor specimens were evaluated prospectively using the PD-L1 IHC 28-8 pharmDx assay at a central laboratory. Randomization was stratified by tumor histology (non-squamous versus squamous). The evaluation of efficacy relied on the comparison between:

- YERVOY 1 mg/kg administered intravenously over 30 minutes every 6 weeks in combination with nivolumab 3 mg/kg administered intravenously over 30 minutes every 2 weeks; or
- Platinum-doublet chemotherapy

Chemotherapy regimens consisted of pemetrexed (500 mg/m^2) and cisplatin (75 mg/m^2) or pemetrexed (500 mg/m^2) and carboplatin (AUC 5 or 6) for non-squamous NSCLC or gemcitabine (1000 or 1250 mg/m^2) and cisplatin (75 mg/m^2) or gemcitabine (1000 mg/m^2) and carboplatin (AUC 5) (gemcitabine was administered on Days 1 and 8 of each cycle) for squamous NSCLC.

Study treatment continued until disease progression, unacceptable toxicity, or for up to 24 months. Treatment continued beyond disease progression if a patient was clinically stable and was considered to be deriving clinical benefit by the investigator. Patients who discontinued combination therapy because of an adverse event attributed to YERVOY were permitted to continue nivolumab as a single agent. Tumor assessments were performed every 6 weeks from the first dose of study treatment for the first 12 months, then every 12 weeks until disease progression or study treatment was discontinued. The primary efficacy outcome measure was OS. Additional efficacy outcome measures included PFS, ORR, and duration of response as assessed by BICR.

In Part 1a, a total of 793 patients were randomized to receive either YERVOY in combination with nivolumab (n=396) or platinum-doublet chemotherapy (n=397). The median age was 64 years (range: 26 to 87) with 49% of patients ≥65 years and 10% of patients ≥75 years, 76% White, and 65% male. Baseline ECOG performance status was 0 (34%) or 1 (65%), 50% with PD-L1 ≥50%, 29% with squamous and 71% with non-squamous histology, 10% had brain metastases, and 85% were former/current smokers.

The study demonstrated a statistically significant improvement in OS for PD-L1 ≥1% patients randomized to the YERVOY and nivolumab arm compared to platinum-doublet chemotherapy arm. The OS results are presented in Table 33 and Figure 8.

Table 33: Efficacy Results (PD-L1 ≥1%) - CHECKMATE-227 Part 1a
 | YERVOY and Nivolumab (n=396) | Platinum-Doublet Chemotherapy (n=397)
Overall Survival
Events (%) | 258 (65%) | 298 (75%)
Median (months)a; (95% CI) | 17.1; (15, 20.1) | 14.9; (12.7, 16.7)
Hazard ratio (95% CI)b | 0.79 (0.67, 0.94)
Stratified log-rank p-value | 0.0066
a Kaplan-Meier estimate.
b Based on a stratified Cox proportional hazard model.

Figure 8: Overall Survival (PD-L1 ≥1%) - CHECKMATE-227

BICR-assessed PFS showed a HR of 0.82 (95% CI: 0.69, 0.97), with a median PFS of 5.1 months (95% CI: 4.1, 6.3) in the YERVOY and nivolumab arm and 5.6 months (95% CI: 4.6, 5.8) in the platinum-doublet chemotherapy arm. The BICR-assessed confirmed ORR was 36% (95% CI: 31, 41) in the YERVOY and nivolumab arm and 30% (95% CI: 26, 35) in the platinum-doublet chemotherapy arm. Median duration of response observed in the YERVOY and nivolumab arm was 23.2 months and 6.2 months in the platinum-doublet chemotherapy arm.

First-line Treatment of Metastatic or Recurrent NSCLC: In Combination with Nivolumab and Platinum-Doublet Chemotherapy

CHECKMATE-9LA (NCT03215706) was a randomized, open-label trial in patients with metastatic or recurrent NSCLC. The trial included patients (18 years of age or older) with histologically confirmed Stage IV or recurrent NSCLC (per the 7th International Association for the Study of Lung Cancer classification [IASLC]), ECOG performance status 0 or 1, and no prior anticancer therapy (including EGFR and ALK inhibitors) for metastatic disease. Patients were enrolled regardless of their tumor PD-L1 status. Patients with known EGFR mutations or ALK translocations sensitive to available targeted inhibitor therapy, untreated brain metastases, carcinomatous meningitis, active autoimmune disease, or medical conditions requiring systemic immunosuppression were excluded from the study. Patients with stable brain metastases were eligible for enrollment.

Patients were randomized 1:1 to receive either:

- YERVOY 1 mg/kg administered intravenously over 30 minutes every 6 weeks, nivolumab 360 mg administered intravenously over 30 minutes every 3 weeks, and platinum-doublet chemotherapy administered intravenously every 3 weeks for 2 cycles, or
- platinum-doublet chemotherapy administered every 3 weeks for 4 cycles.

Platinum-doublet chemotherapy consisted of either carboplatin (AUC 5 or 6) and pemetrexed 500 mg/m^2, or cisplatin 75 mg/m^2 and pemetrexed 500 mg/m^2 for non-squamous NSCLC; or carboplatin (AUC 6) and paclitaxel 200 mg/m^2 for squamous NSCLC. Patients with non-squamous NSCLC in the control arm could receive optional pemetrexed maintenance therapy. Stratification factors for randomization were tumor PD-L1 expression level (≥1% versus <1% or non-quantifiable), histology (squamous versus non-squamous), and sex (male versus female). Study treatment continued until disease progression, unacceptable toxicity, or for up to 2 years. Treatment could continue beyond disease progression if a patient was clinically stable and was considered to be deriving clinical benefit by the investigator. Patients who discontinued combination therapy because of an adverse reaction attributed to YERVOY were permitted to continue nivolumab as a single agent as part of the study. Tumor assessments were performed every 6 weeks from the first dose of study treatment for the first 12 months, then every 12 weeks until disease progression or study treatment was discontinued. The primary efficacy outcome measure was OS. Additional efficacy outcome measures included PFS, ORR, and duration of response as assessed by BICR.

A total of 719 patients were randomized to receive either YERVOY in combination with nivolumab and platinum-doublet chemotherapy (n=361) or platinum-doublet chemotherapy (n=358). The median age was 65 years (range: 26 to 86) with 51% of patients ≥65 years and 10% of patients ≥75 years. The majority of patients were White (89%) and male (70%). Baseline ECOG performance status was 0 (31%) or 1 (68%), 57% had tumors with PD-L1 expression ≥1% and 37% had tumors with PD-L1 expression that was <1%, 32% had tumors with squamous histology and 68% had tumors with non-squamous histology, 17% had CNS metastases, and 86% were former or current smokers.

The study demonstrated a statistically significant benefit in OS, PFS, and ORR. Efficacy results from the prespecified interim analysis when 351 events were observed (87% of the planned number of events for final analysis) are presented in Table 34.

Table 34: Efficacy Results - CHECKMATE-9LA
 | YERVOY and Nivolumab and Platinum-Doublet Chemotherapy (n=361) | Platinum-Doublet Chemotherapy (n=358)
Overall Survival
Events (%) | 156 (43.2) | 195 (54.5)
Median (months) (95% CI) | 14.1 (13.2, 16.2) | 10.7 (9.5, 12.5)
Hazard ratio (96.71% CI)a | 0.69 (0.55, 0.87)
Stratified log-rank p-valueb | 0.0006
Progression-free Survival per BICR
Events (%) | 232 (64.3) | 249 (69.6)
Hazard ratio (97.48% CI)a | 0.70 (0.57, 0.86)
Stratified log-rank p-valuec | 0.0001
Median (months)d (95% CI) | 6.8 (5.6, 7.7) | 5.0 (4.3, 5.6)
Overall Response Rate per BICR (%) | 38 | 25
(95% CI)e | (33, 43) | (21, 30)
Stratified CMH test p-valuef | 0.0003
Duration of Response per BICR
Median (months) (95% CI)d | 10.0 (8.2, 13.0) | 5.1 (4.3, 7.0)
a Based on a stratified Cox proportional hazard model.
b p-value is compared with the allocated alpha of 0.033 for this interim analysis.
c p-value is compared with the allocated alpha of 0.0252 for this interim analysis.
d Kaplan-Meier estimate.
e Confidence interval based on the Clopper and Pearson Method.
f p-value is compared with the allocated alpha of 0.025 for this interim analysis.

With an additional 4.6 months of follow-up the hazard ratio for overall survival was 0.66 (95% CI: 0.55, 0.80) and median survival was 15.6 months (95% CI: 13.9, 20.0) and 10.9 months (95% CI: 9.5, 12.5) for patients receiving YERVOY and nivolumab and platinum-doublet chemotherapy or platinum-doublet chemotherapy, respectively (Figure 9).

Figure 9: Overall Survival - CHECKMATE-9LA

14.7 Malignant Pleural Mesothelioma

CHECKMATE-743 (NCT02899299) was a randomized, open-label trial in patients with unresectable malignant pleural mesothelioma. The trial included patients with histologically confirmed and previously untreated malignant pleural mesothelioma with no palliative radiotherapy within 14 days of initiation of therapy. Patients with interstitial lung disease, active autoimmune disease, medical conditions requiring systemic immunosuppression, or active brain metastasis were excluded from the trial. Patients were randomized 1:1 to receive either:

- YERVOY 1 mg/kg over 30 minutes by intravenous infusion every 6 weeks and nivolumab 3 mg/kg over 30 minutes by intravenous infusion every 2 weeks for up to 2 years, or
- cisplatin 75 mg/m^2 and pemetrexed 500 mg/m^2, or carboplatin 5 AUC and pemetrexed 500 mg/m^2 administered every 3 weeks for 6 cycles.

Stratification factors for randomization were tumor histology (epithelioid vs. sarcomatoid or mixed histology subtypes) and sex (male vs. female). Study treatment continued for up to 2 years, or until disease progression or unacceptable toxicity. Patients who discontinued combination therapy because of an adverse reaction attributed to YERVOY were permitted to continue nivolumab as a single agent. Treatment could continue beyond disease progression if a patient was clinically stable and was considered to be deriving clinical benefit by the investigator. Tumor assessments were performed every 6 weeks from the first dose of study treatment for the first 12 months, then every 12 weeks until disease progression or study treatment was discontinued. The primary efficacy outcome measure was OS. Additional efficacy outcome measures included PFS, ORR, and duration of response as assessed by BICR utilizing modified RECIST criteria.

A total of 605 patients were randomized to receive either YERVOY in combination with nivolumab (n=303) or chemotherapy (n=302). The median age was 69 years (range: 25 to 89), with 72% of patients ≥65 years and 26% ≥75 years; 85% were White, 11% were Asian, and 77% were male. Baseline ECOG performance status was 0 (40%) or 1 (60%), 35% had Stage III and 51% had Stage IV disease, 75% had epithelioid and 25% had non-epithelioid histology, 75% had tumors with PD-L1 expression ≥1%, and 22% had tumors with PD-L1 expression <1%.

The trial demonstrated a statistically significant improvement in OS for patients randomized to YERVOY in combination with nivolumab compared to chemotherapy. Efficacy results from the prespecified interim analysis are presented in Table 35 and Figure 10.

Table 35: Efficacy Results - CHECKMATE-743
 | YERVOY and Nivolumab (n=303) | Chemotherapy (n=302)
Overall Survivala
Events (%) | 200 (66) | 219 (73)
Median (months)b; (95% CI) | 18.1 (16.8, 21.5) | 14.1 (12.5, 16.2)
Hazard ratio (95% CI)c | 0.74 (0.61, 0.89)
Stratified log-rank p-valued | 0.002
Progression-free Survival
Events (%) | 218 (72) | 209 (69)
Hazard ratio (95% CI)c | 1.0 (0.82, 1.21)
Median (months)b; (95% CI) | 6.8 (5.6, 7.4) | 7.2 (6.9, 8.1)
Overall Response Ratee | 40% | 43%
(95% CI) | (34, 45) | (37, 49)
Duration of Response
Median (months)a (95% CI) | 11.0 (8.1, 16.5) | 6.7 (5.3, 7.1)
a At the time of the interim analysis, 419 deaths (89% of the deaths needed for the final analysis) had occurred.
b Kaplan-Meier estimate.
c Stratified Cox proportional hazard model.
d p-value is compared with the allocated alpha of 0.0345 for this interim analysis.
e Based on confirmed response by BICR.

Figure 10: Overall Survival - CHECKMATE-743

In a prespecified exploratory analysis based on histology, in the subgroup of patients with epithelioid histology, the hazard ratio (HR) for OS was 0.85 (95% CI: 0.68, 1.06), with median OS of 18.7 months in the YERVOY and nivolumab arm and 16.2 months in the chemotherapy arm. In the subgroup of patients with non-epithelioid histology, the HR for OS was 0.46 (95% CI: 0.31, 0.70), with median OS of 16.9 months in the YERVOY and nivolumab arm and 8.8 months in the chemotherapy arm.

14.8 Esophageal Cancer

CHECKMATE-648 (NCT03143153) was a randomized, active-controlled, open-label trial in patients with previously untreated unresectable advanced, recurrent or metastatic ESCC (squamous or adenosquamous histology). The trial enrolled patients whose tumor was evaluable for tumor cell (TC) PD-L1 expression [also called PD-L1 tumor proportion score (TPS)], which was evaluated using the PD-L1 IHC 28-8 pharmDx assay at a central laboratory. Patients were not amenable to chemoradiation or surgery with curative intent. A retrospective scoring of a patient’s tumor PD-L1 status using Combined Positive Score (CPS) was also conducted using the PD-L1-stained tumor specimens used for randomization. Prior treatment with curative intent was allowed if completed more than six months prior to trial enrollment. The trial excluded patients with brain metastasis that were symptomatic, had active autoimmune disease, used systemic corticosteroids or immunosuppressants, or patients at high risk of bleeding or fistula due to apparent invasion of tumor to organs adjacent to the esophageal tumor. Patients were randomized to receive one of the following treatments:

- YERVOY 1 mg/kg every 6 weeks in combination with nivolumab 3 mg/kg every 2 weeks.
- Fluorouracil 800 mg/m^2/day intravenously on days 1 through 5 (for 5 days), and cisplatin 80 mg/m^2 intravenously on day 1 (of a 4-week cycle).

Patients were treated until disease progression, unacceptable toxicity, or up to 2 years. Patients who discontinued combination therapy because of an adverse reaction attributed to YERVOY were permitted to continue nivolumab as a single agent.

Randomization was stratified by TC PD-L1 expression (≥1% vs. <1% or indeterminate), region (East Asia vs. Rest of Asia vs. Rest of World), ECOG performance status (0 vs. 1), and number of organs with metastases (≤1 vs. ≥2). The major efficacy outcome measures were OS and BICR-assessed PFS in patients with TC PD-L1 expression ≥1%. Additional efficacy measures included OS in all randomized patients, BICR-assessed PFS in all randomized patients, and ORR assessed by BICR in TC PD-L1 expression ≥1% and in all randomized patients. The tumor assessments per RECIST v1.1 were conducted every 6 weeks up to and including week 48, then every 12 weeks thereafter.

A total of 649 patients were randomized in Arms A and C of the CHECKMATE-648 study, among whom 644 and 601 patients had quantifiable TC PD-L1 expression and CPS at baseline, respectively; 84% (546/649) had tumors with PD-L1 CPS ≥1. The trial population characteristics in patients with PD-L1 CPS ≥1 were: median age 63 years (range: 26 to 81), 45% were ≥65 years of age, 84% were male, 71% were Asian, 25% were White, and 1.6% were Black or African American. Patients had histological confirmation of squamous cell carcinoma (99%) or adenosquamous cell carcinoma (1.3%) in the esophagus. Baseline ECOG performance status was 0 (46%) or 1 (54%).

A statistically significant improvement in OS was demonstrated in patients randomized to YERVOY in combination with nivolumab compared with chemotherapy; however, an exploratory analysis of OS in patients with PD-L1 CPS <1 showed a HR of 1.0 (95% CI 0.52, 1.94), including that the improvement in the ITT population was primarily attributed to the results observed in the subgroup of patients with PD-L1 CPS ≥1. Efficacy results are shown in Table 36 and Figures 11 and 12.

Table 36: Efficacy Results - Arms A and C of CHECKMATE-648
 | YERVOY and Nivolumab (n=158) | Cisplatin and Fluorouracil (n=157) | YERVOY and Nivolumab (n=266) | Cisplatin and Fluorouracil (n=280)
 | TC PD-L1 expression ≥1% |  | PD-L1 CPS ≥1
Overall Survival
Deaths (%) | 106 (67) | 121 (77) | 179 (67) | 205 (73)
Median (months); (95% CI) | 13.7; (11.2, 17.0) | 9.1; (7.7, 10) | 12.7; (10.9, 15.5) | 9.8; (8.8, 11.6)
Hazard ratio (95% CI)b | 0.64; (0.49, 0.84) |  | 0.76; (0.62, 0.93)
p-valuec | 0.0010S1 |  | -
Progression-free Survivala
Disease progression or death (%) | 123 (78) | 100 (64) | 206 (77) | 184 (66)
Median (months); (95% CI) | 4.0; (2.4, 4.9) | 4.4; (2.9, 5.8) | 2.8; (2.6, 4.2) | 5.6; (4.2, 5.9)
Hazard ratio (95% CI)b | 1.02; (0.78, 1.34) |  | 1.2; (1.0, 1.5)
p-valuec | NS |  | -
Overall Response Rate, n (%)a, NT | 56 (35.4) | 31 (19.7) | 74 (28) | 76 (27)
(95% CI) | (28.0, 43.4) | (13.8, 26.8) | (22.5, 33.6) | (22.0, 32.8)
Complete response (%) | 28 (17.7) | 8 (5.1) | 32 (12.0) | 18 (6.4)
Partial response (%) | 28 (17.7) | 23 (14.6) | 42 (15.8) | 58 (20.7)
Median; (95% CI) | 11.8; (7.1, 27.4) | 5.7; (4.4, 8.7) | 11.8; (7.1, 23.6) | 6.9; (5.7, 8.2)
Range | 1.4+, 34.5+ | 1.4+, 31.8+ | 1.4+, 34.5+ | 1.4+, 31.8+
a Assessed by BICR.
b Based on stratified Cox proportional hazard model. Hazard ratios are reported for each nivolumab- containing arm compared to chemotherapy within each analysis population.
c Based on a stratified 2-sided log-rank test.
S1 Significant p-value compared to stopping boundary of 0.014.
NS: Not Statistically significant, NT: Not evaluated for statistical significance as per pre-specified hierarchical testing procedure.

Figure 11: Overall Survival - CHECKMATE-648

(A) OS in TC PD-L1 ≥1%

(B) OS in PD-L1 CPS ≥1

Figure 12: Progression-free Survival – CHECKMATE-648

(A) PFS in TC PD-L1 ≥1%

(B) PFS in PD-L1 CPS ≥1

16 HOW SUPPLIED/STORAGE AND HANDLING

YERVOY (ipilimumab) injection is a sterile, preservative-free, clear to slightly opalescent, colorless to pale-yellow solution. YERVOY is available as follows:

Carton Contents | NDC
One 50 mg/10 mL (5 mg/mL), single-dose vial | NDC 0003-2327-11
One 200 mg/40 mL (5 mg/mL), single-dose vial | NDC 0003-2328-22

Store YERVOY under refrigeration at 2°C to 8°C (36°F to 46°F). Protect YERVOY from light by storing in the original carton until time of use. Do not freeze or shake.

17 PATIENT COUNSELING INFORMATION

Advise the patient to read the FDA-approved patient labeling (Medication Guide).

Immune-Mediated Adverse Reactions

Advise patients that YERVOY can cause immune-mediated adverse reactions including the following [see Warnings and Precautions (5.1)]:

- Immune-Mediated Diarrhea or Colitis: Advise patients to contact their healthcare provider immediately for signs or symptoms of diarrhea or colitis.
- Immune-Mediated Hepatitis: Advise patients to contact their healthcare provider immediately for signs or symptoms of hepatitis.
- Immune-Mediated Dermatologic Adverse Reactions: Advise patients to contact their healthcare provider immediately if they develop a new rash.
- Immune-Mediated Endocrinopathies: Advise patients to contact their healthcare provider immediately for signs or symptoms of hypophysitis, adrenal insufficiency, hypothyroidism, hyperthyroidism, and diabetes mellitus.
- Immune-Mediated Pneumonitis: Advise patients to contact their healthcare provider immediately for any new or worsening symptoms of pneumonitis.
- Immune-Mediated Nephritis with Renal Dysfunction: Advise patients to contact their healthcare provider immediately for signs or symptoms of nephritis.

Infusion-Related Reactions

- Advise patients who are receiving YERVOY of the potential risk of an infusion-related reaction [see Warnings and Precautions (5.2)].

Embryo-Fetal Toxicity

- Advise pregnant women of the potential risk to a fetus. Advise females of reproductive potential to inform their healthcare provider of a known or suspected pregnancy [see Warnings and Precautions (5.4), Use in Specific Populations (8.3)].
- Advise females of reproductive potential to use effective contraception during treatment with YERVOY and for 3 months after the last dose [see Use in Specific Populations (8.3)].
- Advise patients who may have been exposed to YERVOY during pregnancy to contact Bristol-Myers Squibb at 1-844-593-7869 [see Use in Specific Populations (8.1)].

Lactation

- Advise women not to breastfeed during treatment with YERVOY and for 3 months after the last dose [see Use in Specific Populations (8.2)].

Manufactured by:
Bristol-Myers Squibb Company
Princeton, NJ 08543 USA
U.S. License No. 1713

[print code]

MEDICATION GUIDE

YERVOY® (yur-voi)
(ipilimumab)
injection

Read this Medication Guide before you start receiving YERVOY and before each infusion. There may be new information. If your healthcare provider prescribes YERVOY in combination with nivolumab, also read the Medication Guide that comes with nivolumab. This Medication Guide does not take the place of talking with your healthcare provider about your medical condition or your treatment.

What is the most important information I should know about YERVOY?

YERVOY is a medicine that may treat certain cancers by working with your immune system. YERVOY can cause your immune system to attack normal organs and tissues in any area of your body and can affect the way they work. These problems can sometimes become severe or life-threatening and can lead to death. You may have more than one of these problems at the same time. These problems may happen anytime during treatment or even after your treatment has ended. Some of these problems may happen more often when YERVOY is used in combination with nivolumab.

Call or see your healthcare provider right away if you develop any new or worse signs or symptoms, including:

Intestinal problems.

- diarrhea (loose stools) or more frequent bowel movements than usual
- stools that are black, tarry, sticky, or have blood or mucus
- severe stomach-area (abdominal) pain or tenderness

Liver problems.

- yellowing of your skin or the whites of your eyes
- severe nausea or vomiting
- pain on the right side of your stomach-area (abdomen)

- dark urine (tea colored)
- bleeding or bruising more easily than normal

Skin problems.

- rash
- itching

- skin blistering or peeling
- painful sores in mouth or nose, throat, or genital area

Hormone gland problems.

- headache that will not go away or unusual headaches
- eye sensitivity to light
- eye problems
- rapid heartbeat
- increased sweating
- extreme tiredness
- weight gain or weight loss
- feeling more hungry or thirsty than usual

- urinating more often than usual
- hair loss
- feeling cold
- constipation
- your voice gets deeper
- dizziness or fainting
- changes in mood or behavior, such as decreased sex drive, irritability, or forgetfulness

Lung problems.

- new or worsening cough

- shortness of breath

- chest pain

Kidney problems.

- decrease in your amount of urine
- blood in your urine

- swelling of your ankles
- loss of appetite

Eye problems.

- blurry vision, double vision, or other vision problems

- eye pain or redness

Problems can also happen in other organs and tissues. These are not all of the signs and symptoms of immune system problems that can happen with YERVOY. Call or see your healthcare provider right away for any new or worsening signs or symptoms.

- Chest pain, irregular heartbeat, shortness of breath or swelling of ankles
- Confusion, sleepiness, memory problems, changes in mood or behavior, stiff neck, balance problems, tingling or numbness of the arms or legs
- Double vision, blurry vision, sensitivity to light, eye pain, changes in eyesight
- Persistent or severe muscle pain or weakness, muscle cramps
- Low red blood cells, bruising

Getting medical treatment right away may help keep these problems from becoming more serious. Your healthcare provider will check you for these problems during your treatment with YERVOY. Your healthcare provider may treat you with corticosteroid or hormone replacement medicines. Your healthcare provider may also need to delay or completely stop treatment with YERVOY if you have severe side effects.

What is YERVOY?

YERVOY is a prescription medicine used:

- to treat a kind of skin cancer called melanoma.
  - YERVOY may be used alone or in combination with nivolumab in adults and children 12 years of age and older when melanoma has spread or cannot be removed by surgery.
  - YERVOY may be used alone in adults to help prevent melanoma from coming back after it and lymph nodes that contain cancer have been removed by surgery.
- in adults with kidney cancer (renal cell carcinoma). YERVOY may be used in combination with nivolumab in certain people when their cancer has spread.
- in adults and children 12 years of age and older, with a type of colon or rectal cancer (colorectal cancer).
  - YERVOY may be used in combination with nivolumab when your colon or rectal cancer:
    - cannot be removed with surgery, or has spread, and
    - is microsatellite instability-high (MSI-H) or mismatch repair deficient (dMMR).
- in adults with liver cancer (hepatocellular carcinoma).
  - YERVOY may be used in combination with nivolumab as your first treatment when your liver cancer:
    - cannot be removed by surgery, or
    - has spread.
  - YERVOY may be used in combination with nivolumab when your liver cancer:
    - cannot be removed by surgery, or
    - has spread, and
    - you have received prior treatment with sorafenib.
- in adults with a type of lung cancer called non-small cell lung cancer (NSCLC).
  - YERVOY may be used in combination with nivolumab as your first treatment for NSCLC:
    - when your lung cancer has spread to other parts of your body (metastatic), and
    - your tumors are positive for PD-L1, but do not have an abnormal EGFR or ALK gene.
  - YERVOY may be used in combination with nivolumab and 2 cycles of chemotherapy that contains platinum and another chemotherapy medicine, as the first treatment of your NSCLC when your lung cancer:
    - has spread or grown, or comes back, and
    - your tumor does not have an abnormal EGFR or ALK gene.
- in adults with a type of cancer that affects the lining of the lungs and chest wall called malignant pleural mesothelioma.
  - YERVOY may be used in combination with nivolumab as your first treatment for malignant pleural mesothelioma that cannot be removed by surgery.
- in adults with cancer of the tube that connects your throat to your stomach (esophageal cancer).
  - YERVOY may be used in combination with nivolumab as your first treatment when your esophageal cancer:
    - is a type called squamous cell carcinoma, and
    - cannot be removed with surgery (advanced), or has spread to the other parts of the body (metastatic), and
    - your tumors are positive for PD-L1.

It is not known if YERVOY is safe and effective in children younger than 12 years of age with melanoma that has spread or cannot be removed by surgery, or with MSI-H or dMMR metastatic colorectal cancer.

It is not known if YERVOY is safe and effective in children for the treatment of any other cancers.

Before you receive YERVOY, tell your healthcare provider about all your medical conditions, including if you:

- have immune system problems such as ulcerative colitis, Crohn’s disease, or lupus
- have received an organ transplant
- have received or plan to receive a stem cell transplant that uses donor stem cells (allogeneic)
- have a condition that affects your nervous system, such as myasthenia gravis or Guillain-Barré syndrome
- are pregnant or plan to become pregnant. YERVOY can harm your unborn baby.
Females who are able to become pregnant:
  1. Your healthcare provider will give you a pregnancy test before you start treatment with YERVOY.
  2. You should use an effective method of birth control during treatment and for 3 months after your last dose of YERVOY. Talk to your healthcare provider about birth control methods that you can use during this time.
  3. Tell your healthcare provider right away if you become pregnant or think you may be pregnant during treatment with YERVOY. You or your healthcare provider should contact Bristol-Myers Squibb at 1-844-593-7869 as soon as you become aware of a pregnancy.
- are breastfeeding or plan to breastfeed. It is not known if YERVOY passes into your breast milk. Do not breastfeed during treatment and for 3 months after your last dose of YERVOY.

Tell your healthcare provider about all the medicines you take, including prescription and over-the-counter medicines, vitamins, and herbal supplements.

How will I receive YERVOY?

- Your healthcare provider will give you YERVOY into your vein through an intravenous (IV) line.
- YERVOY is usually given over 30 minutes.
- If you are receiving YERVOY as treatment for melanoma that has been removed by surgery to help prevent it from coming back, YERVOY will be given over 30 minutes.
- In combination with nivolumab, YERVOY is usually given every 3 weeks for up to 4 doses. After that, nivolumab alone is usually given every 2 or 4 weeks.
- For NSCLC that has spread to other parts of your body, YERVOY is given every 6 weeks and nivolumab is given every 3 weeks for up to 2 years. Your healthcare provider will determine if you will also need to receive chemotherapy every 3 weeks for 2 cycles.
- For malignant pleural mesothelioma that cannot be removed by surgery, YERVOY is given every 6 weeks and nivolumab is given every 3 weeks for up to 2 years.
- When YERVOY is used in combination with nivolumab for esophageal squamous cell carcinoma (ESCC), YERVOY is given every 6 weeks and nivolumab is given every 2 or 3 weeks for up to 2 years.
- Your healthcare provider will decide how many treatments you will need.
- Your healthcare provider will do blood tests before starting and during treatment with YERVOY.
- If you miss any appointments, call your healthcare provider as soon as possible to reschedule your appointment.

What are the possible side effects of YERVOY?

YERVOY can cause serious side effects, including:

- See “What is the most important information I should know about YERVOY?”
- Severe infusion-related reactions. Tell your healthcare provider or nurse right away if you get these symptoms during an infusion of YERVOY:

- chills or shaking
- itching or rash
- flushing
- shortness of breath or wheezing

- dizziness
- feel like passing out
- fever
- back or neck pain

- Complications, including graft-versus-host disease (GVHD), in people who have received a bone marrow (stem cell) transplant that uses donor stem cells (allogeneic). These complications can be severe and can lead to death. These complications may happen if you underwent transplantation either before or after being treated with YERVOY. Your healthcare provider will monitor you for these complications.

The most common side effects of YERVOY when used alone include:

- feeling tired
- diarrhea
- nausea
- itching
- rash
- vomiting

- headache
- weight loss
- fever
- decreased appetite
- difficulty falling or staying asleep

The most common side effects of YERVOY when used in combination with nivolumab include:

- feeling tired
- diarrhea
- rash
- itching
- nausea
- pain in muscles, bones, and joints
- fever
- cough
- decreased appetite

- vomiting
- stomach-area (abdominal) pain
- shortness of breath
- upper respiratory tract infection
- headache
- low thyroid hormone levels (hypothyroidism)
- constipation
- decreased weight
- dizziness

The most common side effects of YERVOY when used in combination with nivolumab and chemotherapy include:

- feeling tired
- pain in muscles, bones, and joints
- nausea
- diarrhea

- rash
- decreased appetite
- constipation
- itching

These are not all of the possible side effects of YERVOY.

Call your doctor for medical advice about side effects. You may report side effects to FDA at 1-800-FDA-1088.

General information about the safe and effective use of YERVOY.

Medicines are sometimes prescribed for purposes other than those listed in a Medication Guide. If you would like more information about YERVOY, talk with your healthcare provider. You can ask your healthcare provider or pharmacist for information about YERVOY that is written for health professionals.

What are the ingredients of YERVOY?

Active ingredient: ipilimumab

Inactive ingredients: diethylene triamine pentaacetic acid (DTPA), mannitol, polysorbate 80 (vegetable origin), sodium chloride, tris hydrochloride, and Water for Injection

Manufactured by: Bristol-Myers Squibb Company, Princeton, NJ 08543 USA
U.S. License No. 1713

YERVOY® is a trademark of Bristol-Myers Squibb Company. All other trademarks are the property of their respective owners.

For more information, call 1-800-321-1335

This Medication Guide has been approved by the U.S. Food and Drug Administration. Revised: May 2025

YERVOY 50 mg/10 mL Representative Packaging

See How Supplied section for a complete list of available packages of YERVOY.

NDC 0003-2327-11
Rx only
YERVOY®
(ipilimumab)
Injection
50 mg/10 mL
(5 mg/mL)
For Intravenous Infusion Only
Single-use vial; Discard unused portion
DISPENSE ENCLOSED MEDICATION GUIDE TO EACH PATIENT
Bristol-Myers Squibb

YERVOY 200 mg/40 mL Representative Packaging

NDC 0003-2328-22
Rx only
YERVOY®
(ipilimumab)
Injection
200 mg/40 mL
(5 mg/mL)
For Intravenous Infusion Only
Single-use vial; Discard unused portion
DISPENSE ENCLOSED MEDICATION GUIDE TO EACH PATIENT
Bristol-Myers Squibb